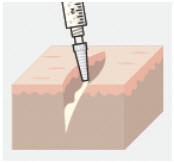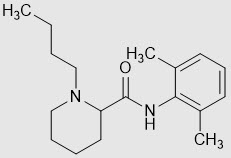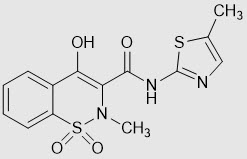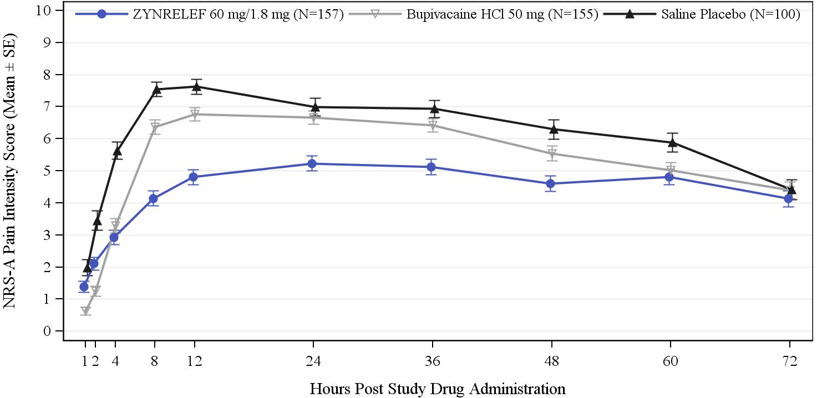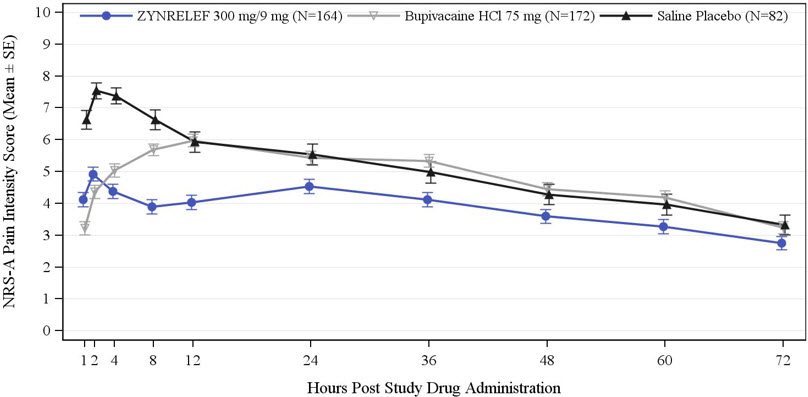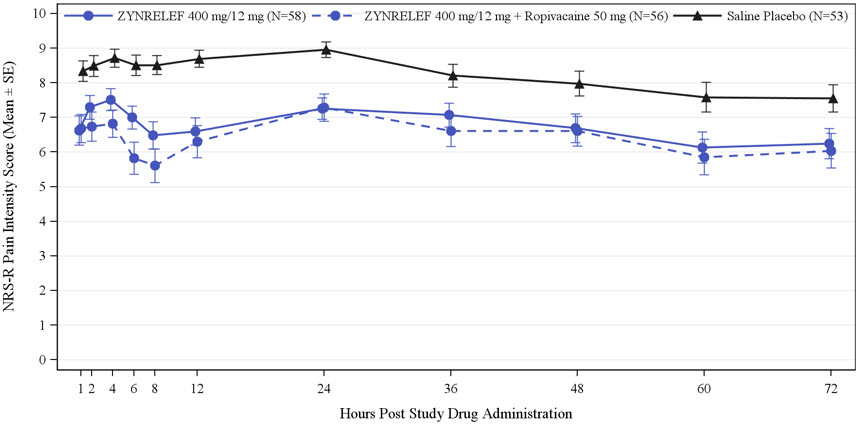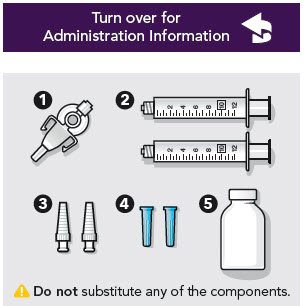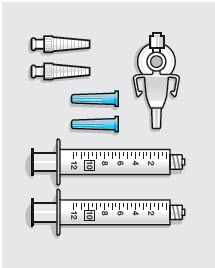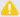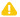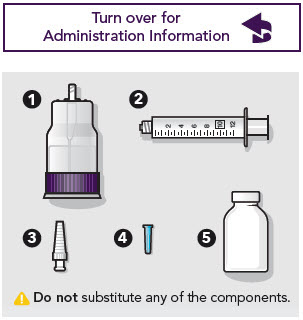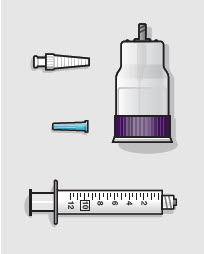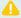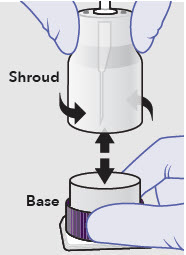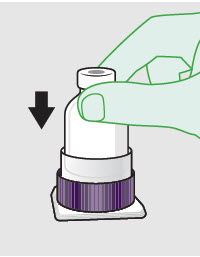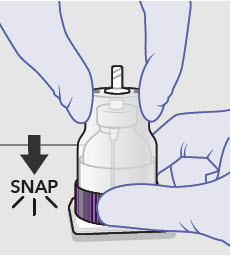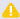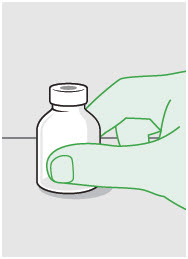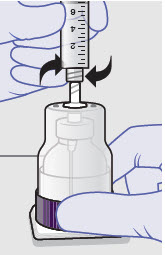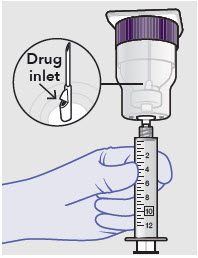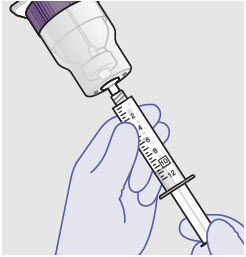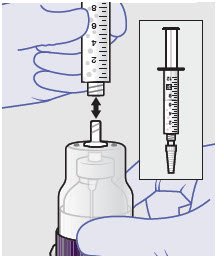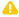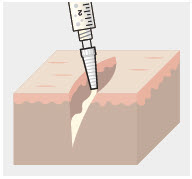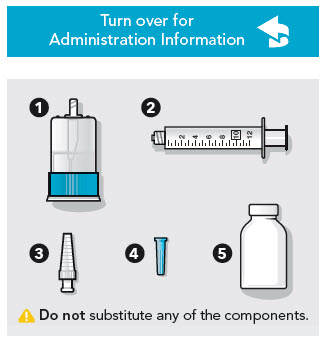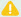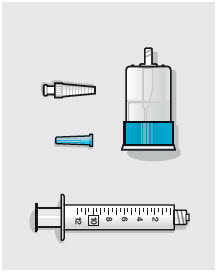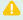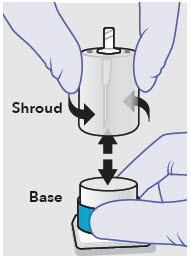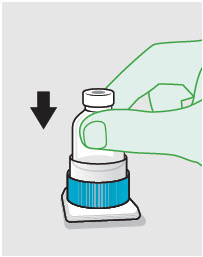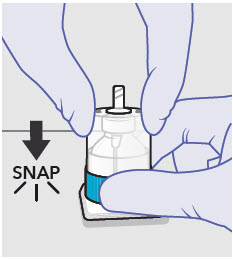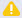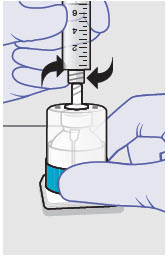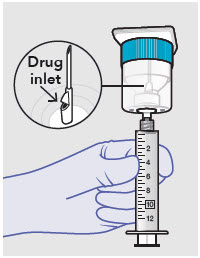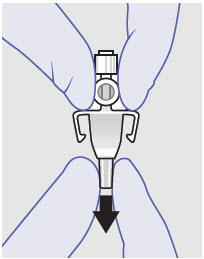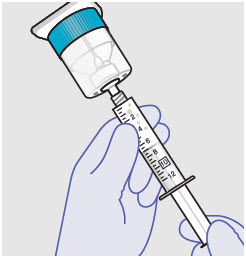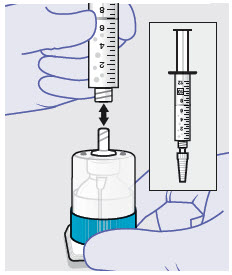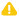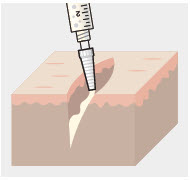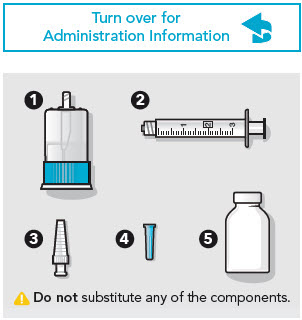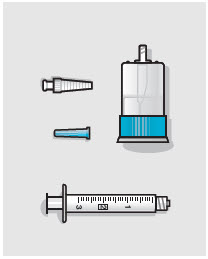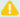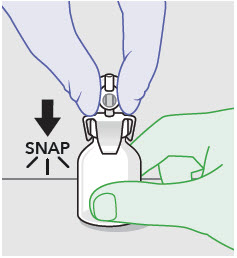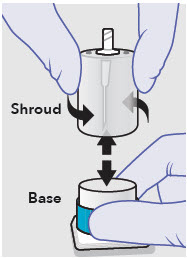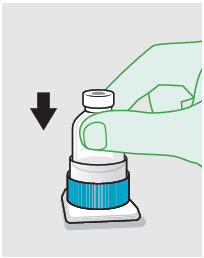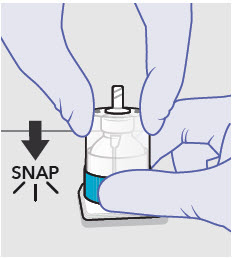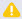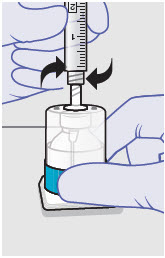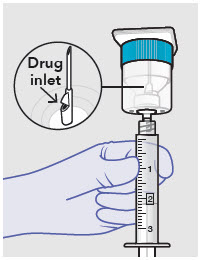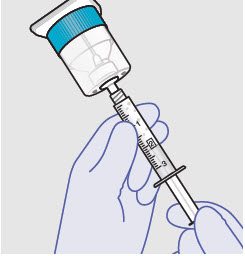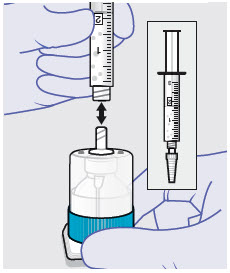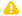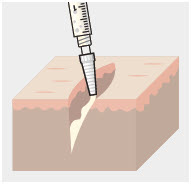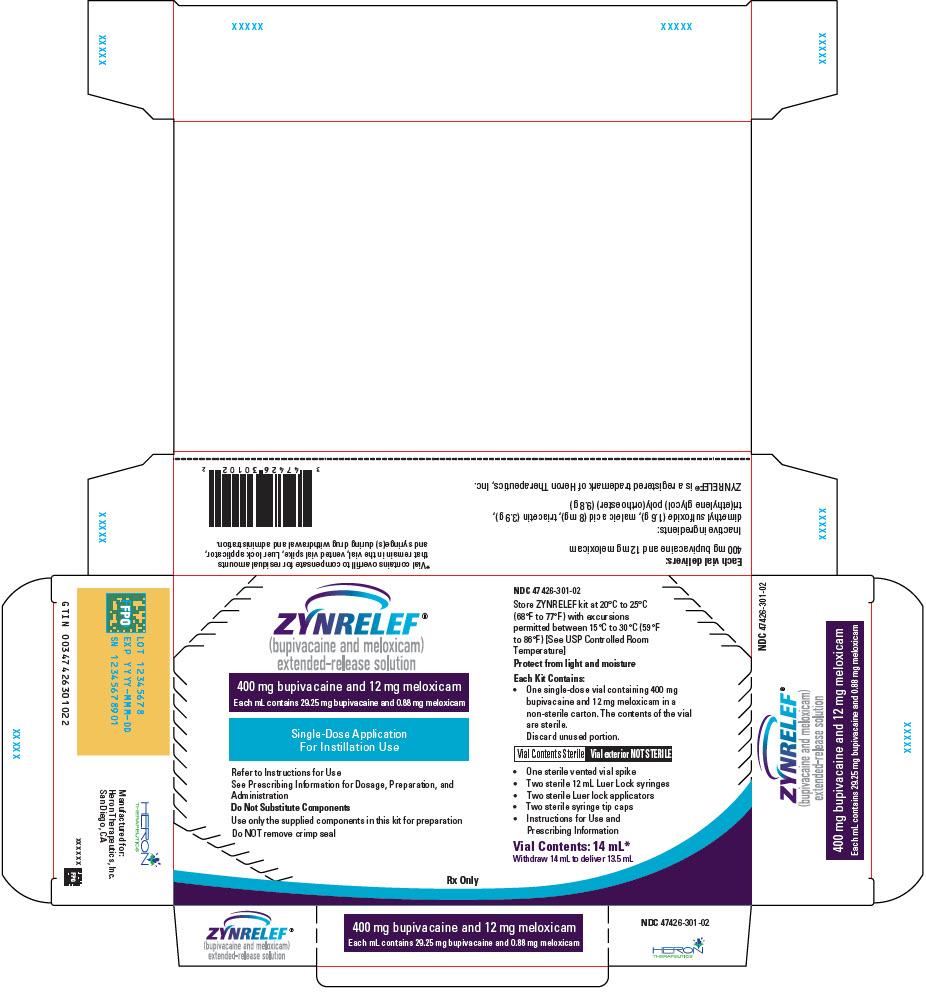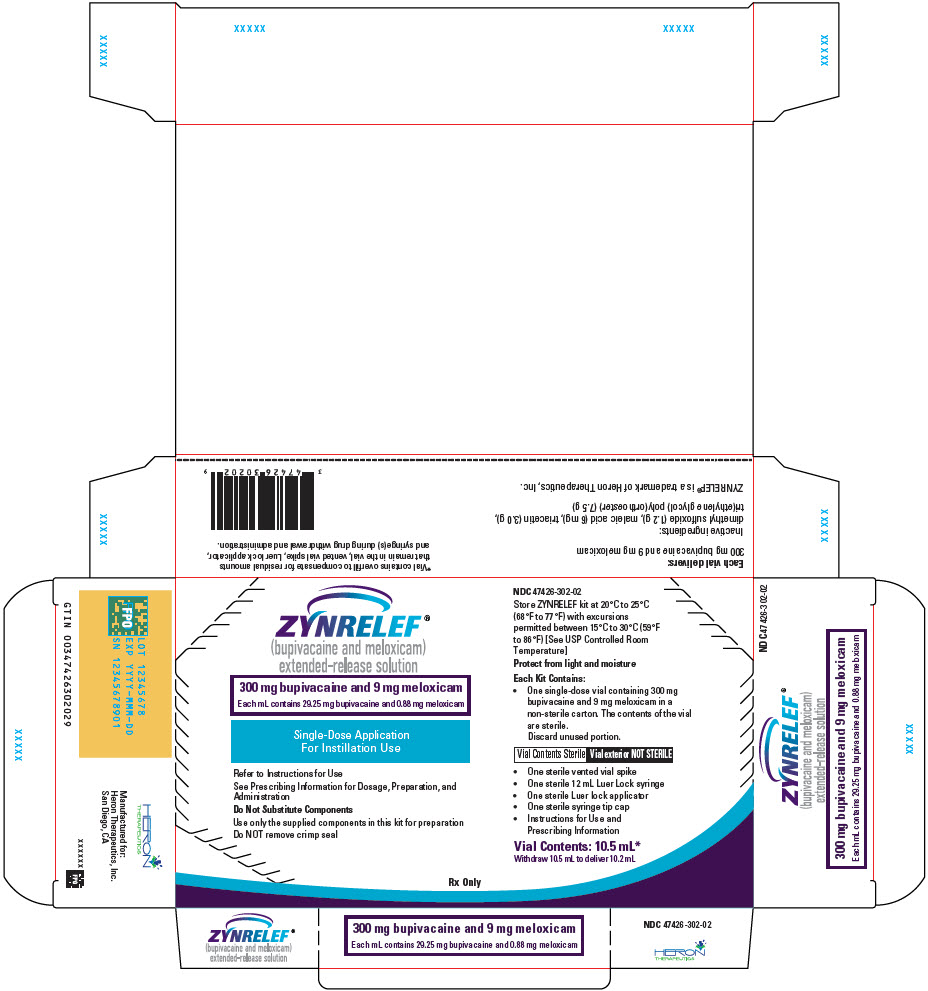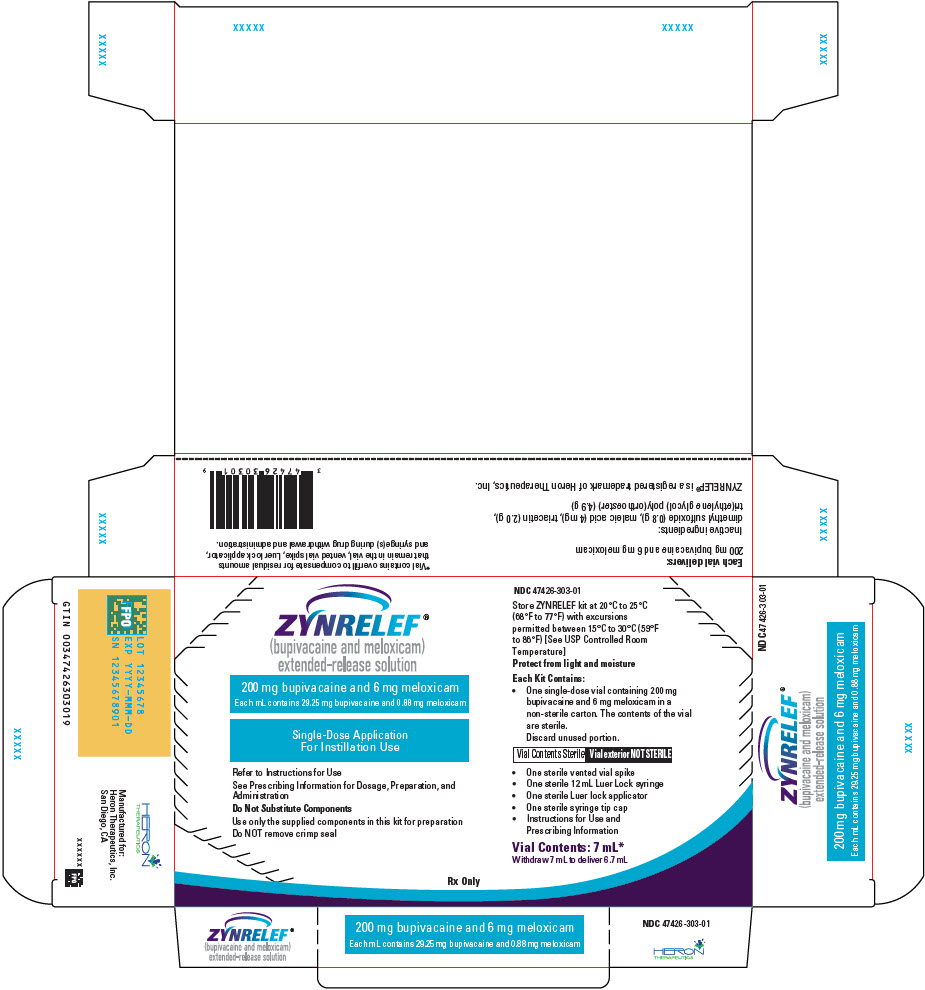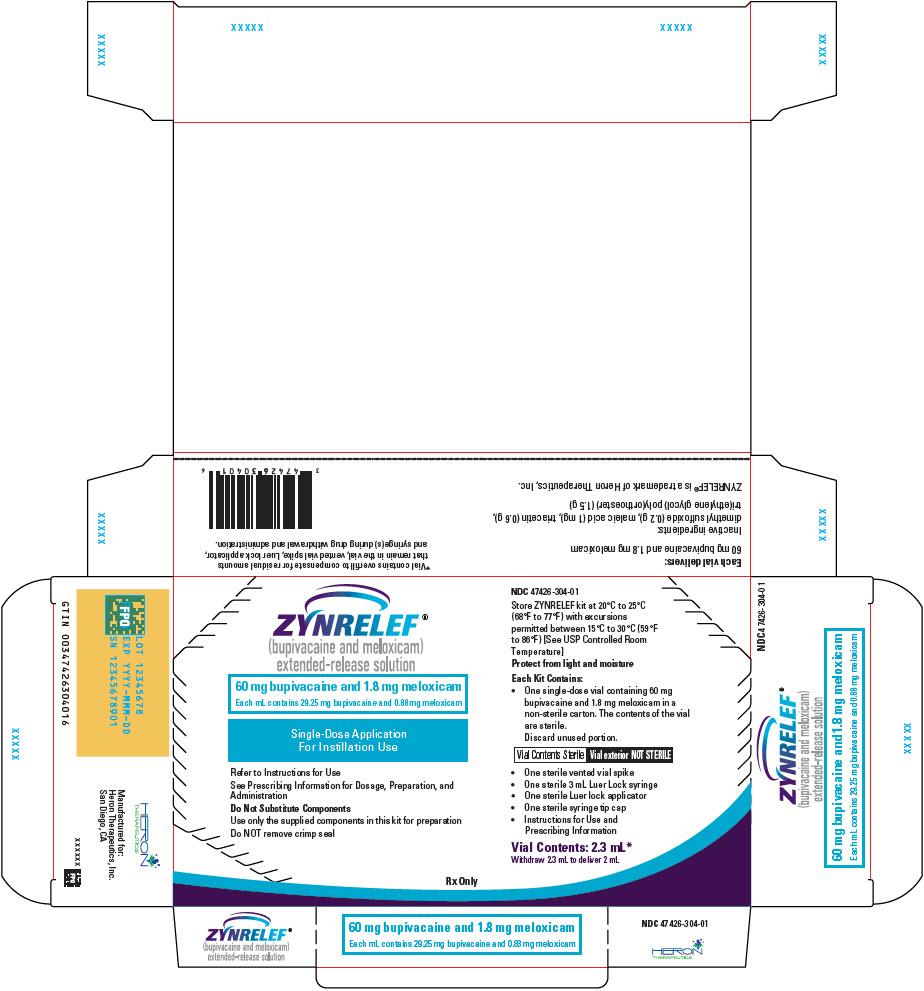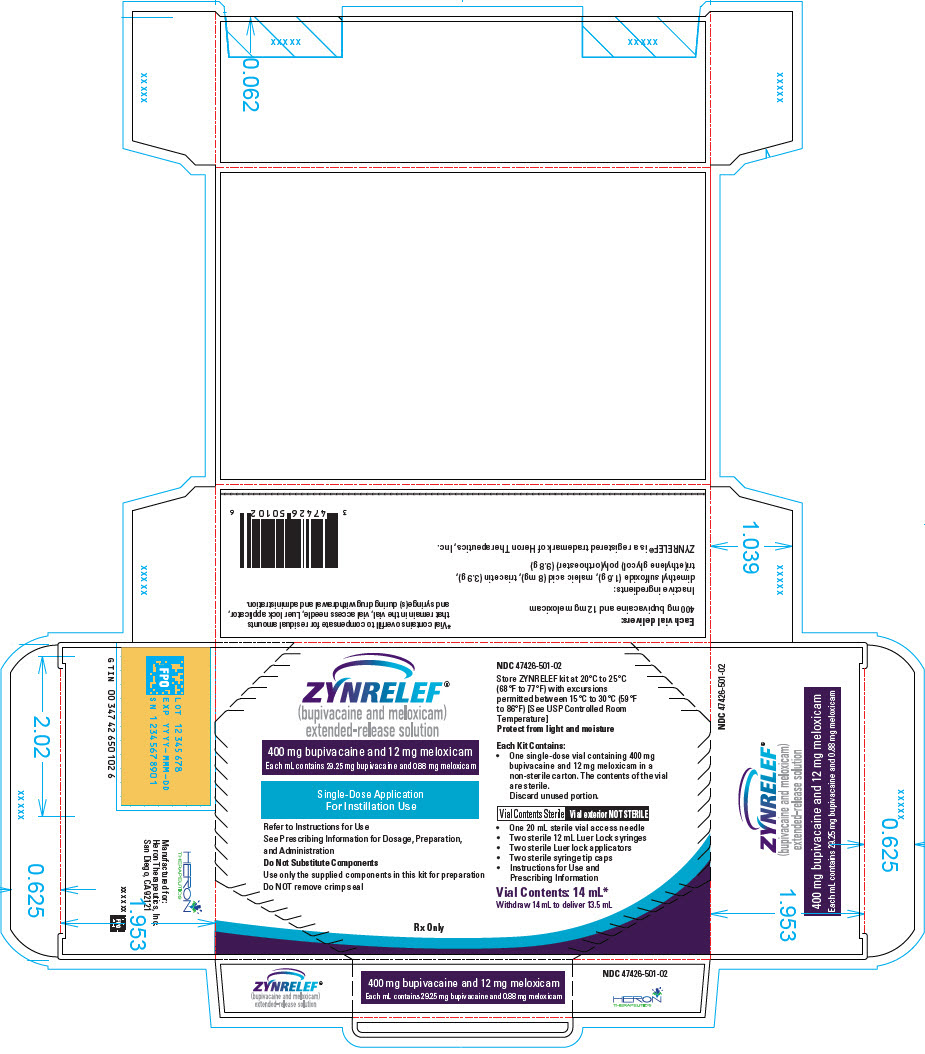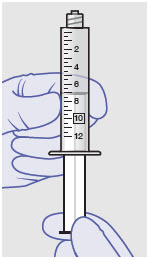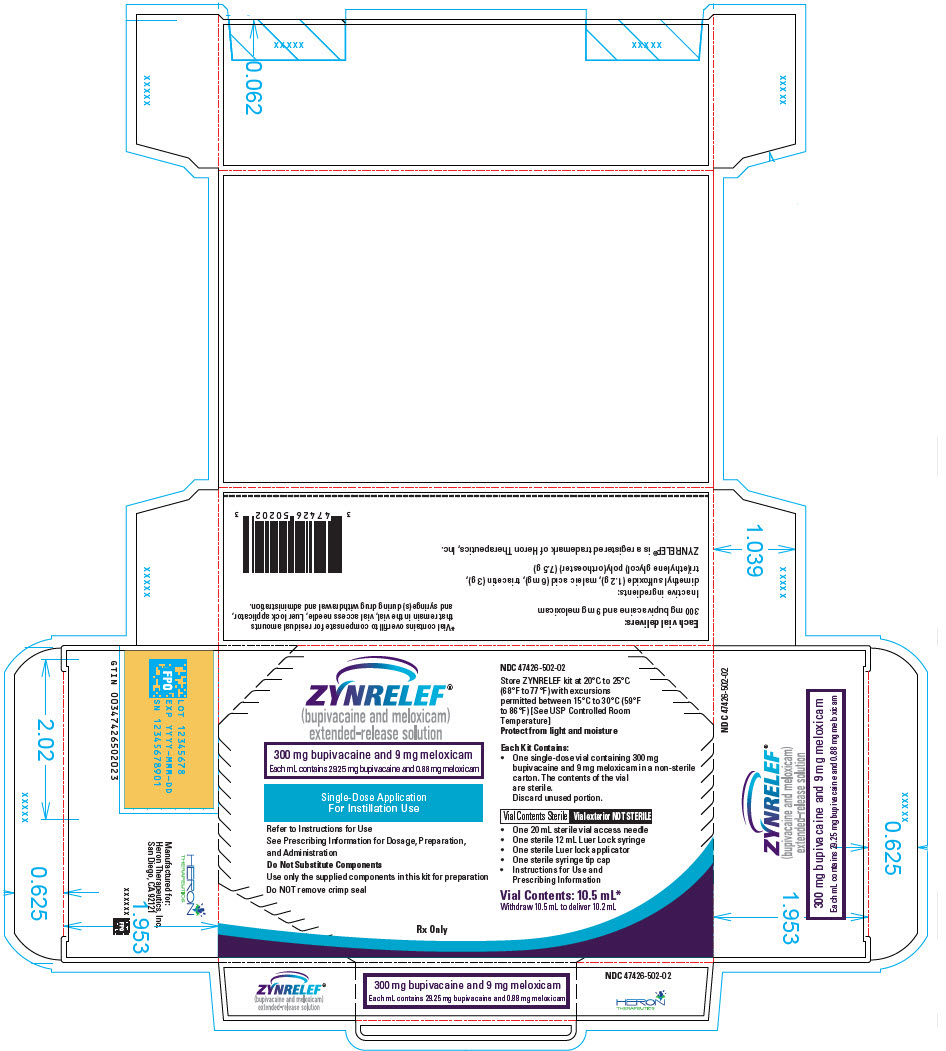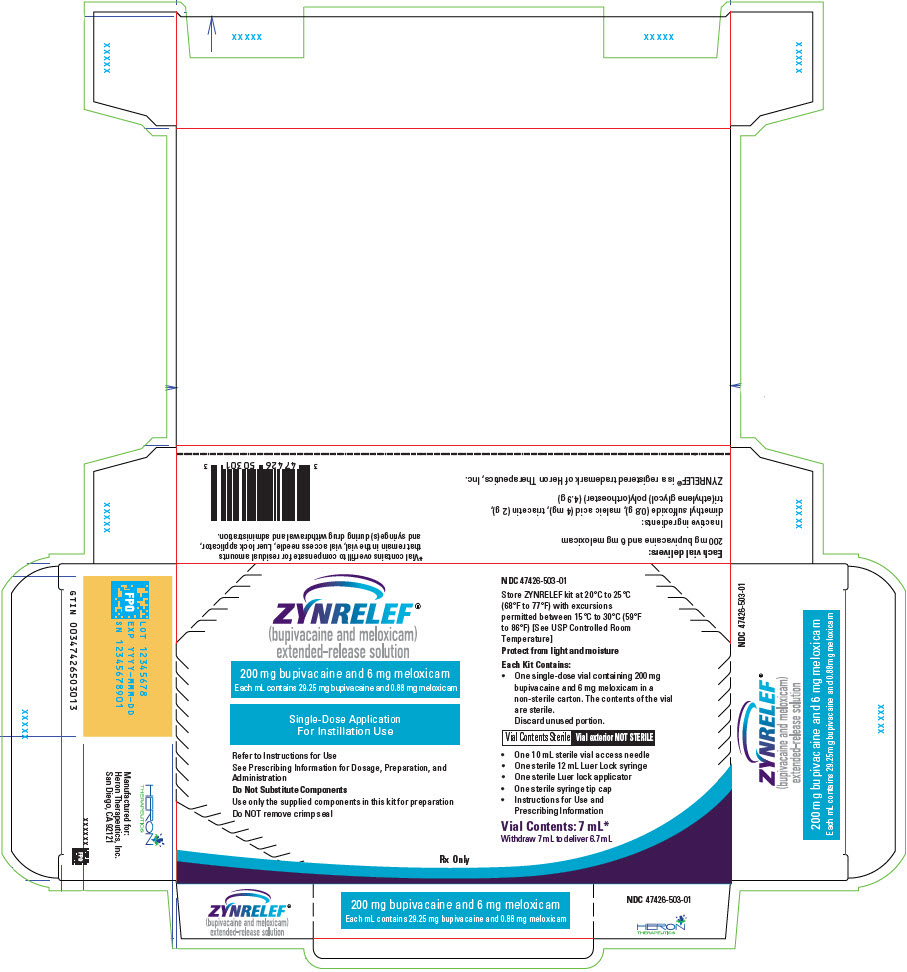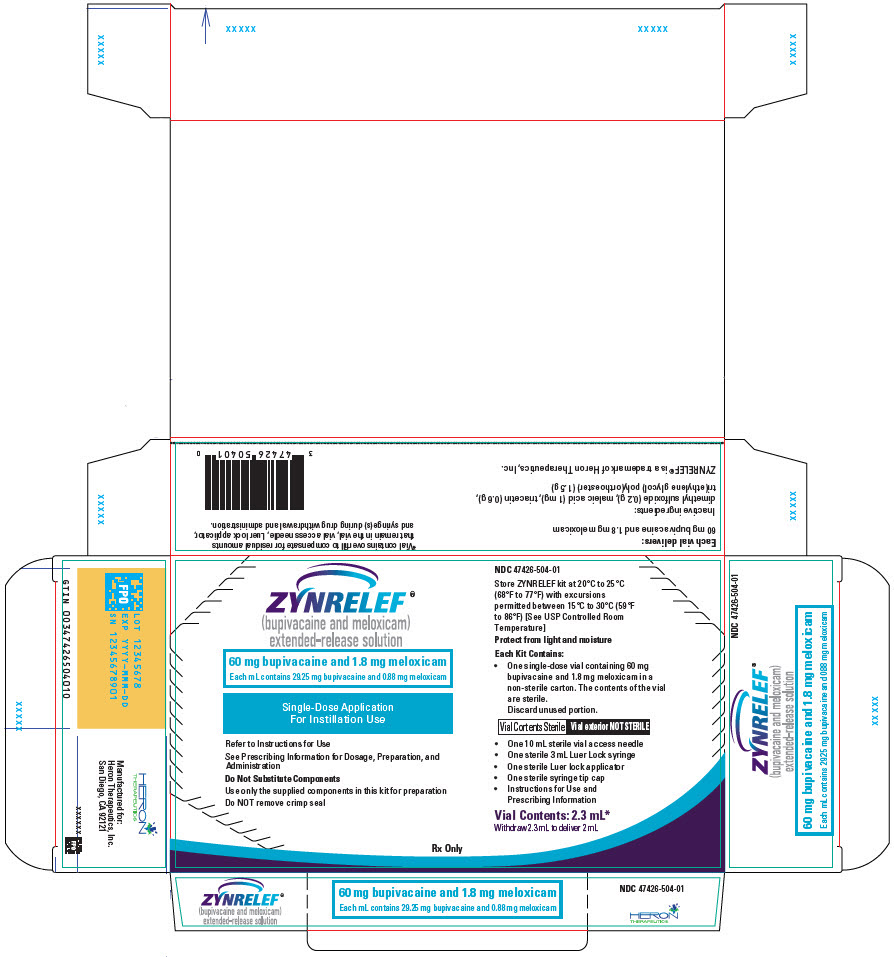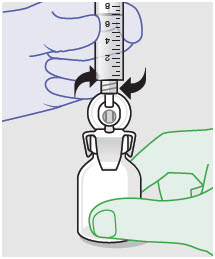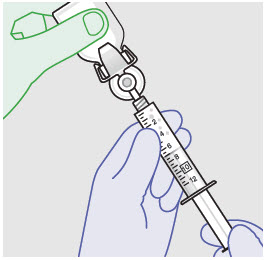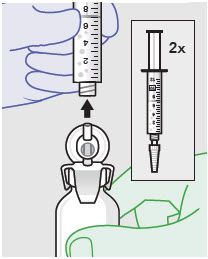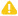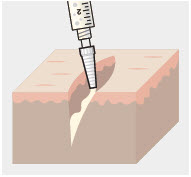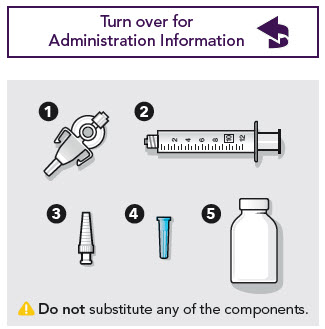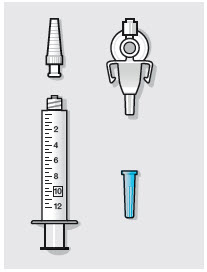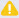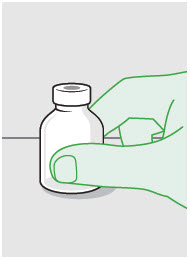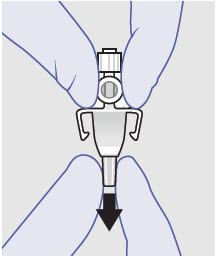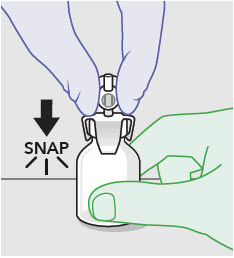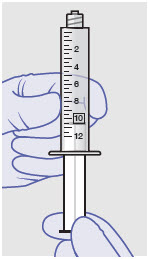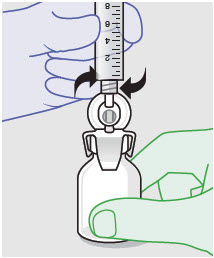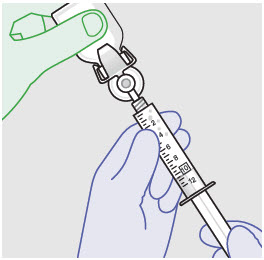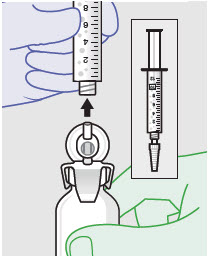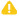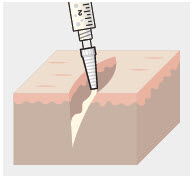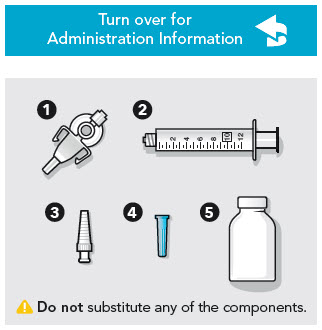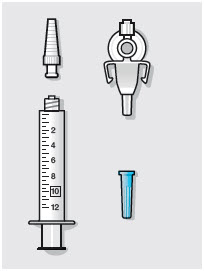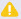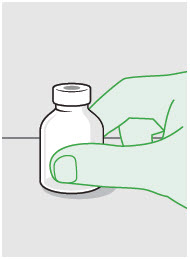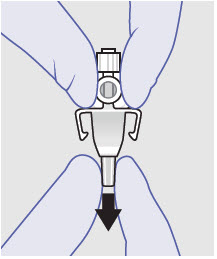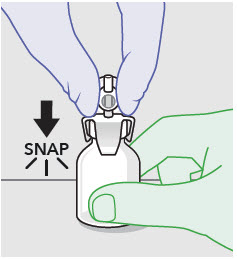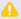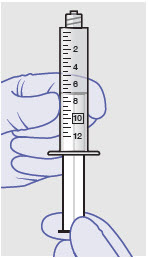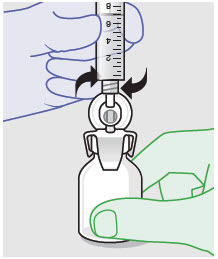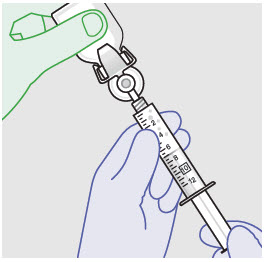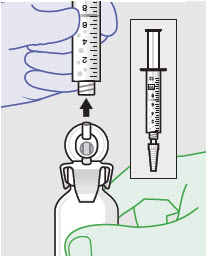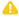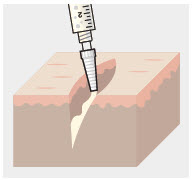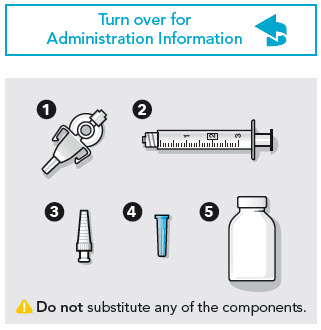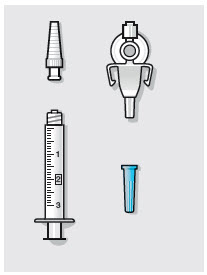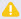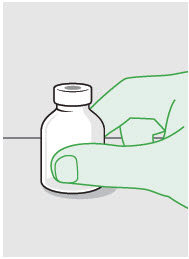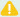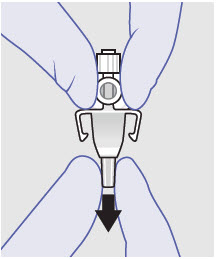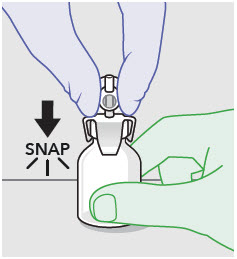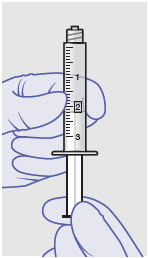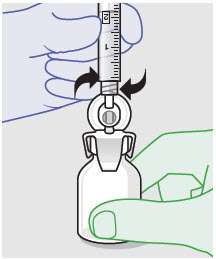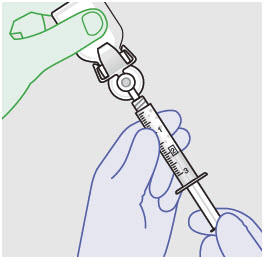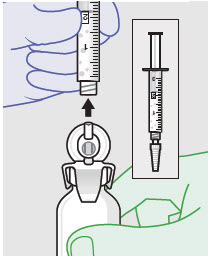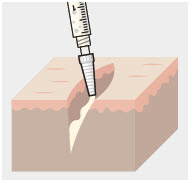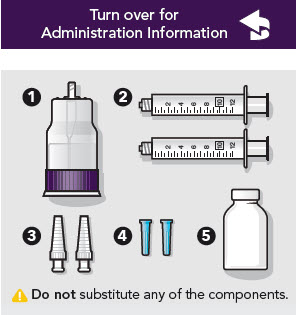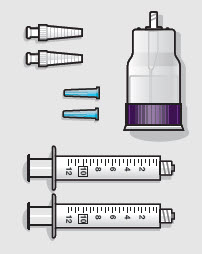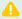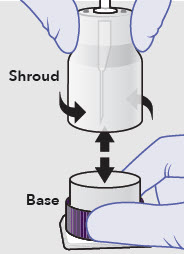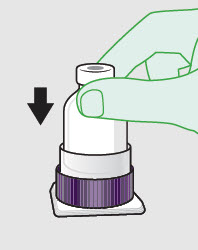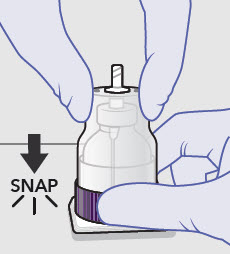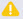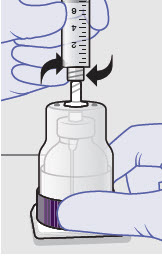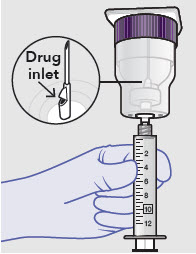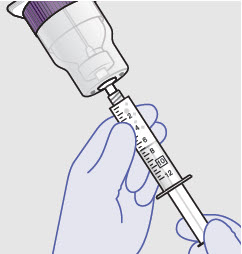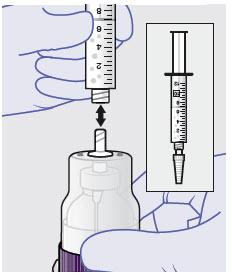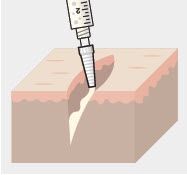 DRUG LABEL: ZYNRELEF
NDC: 47426-301 | Form: SOLUTION
Manufacturer: Heron Therapeutics, Inc.
Category: prescription | Type: HUMAN PRESCRIPTION DRUG LABEL
Date: 20250530

ACTIVE INGREDIENTS: BUPIVACAINE 400 mg/14 mL; MELOXICAM 12 mg/14 mL
INACTIVE INGREDIENTS: dimethyl sulfoxide 1.6 g/14 mL; maleic acid 8 mg/14 mL; triacetin 3.9 g/14 mL; DETOSU/TRIETHYLENE GLYCOL/TRIETHYLENE GLYCOL POLYGLYCOLIDE COPOLYMER 9.8 g/14 mL

HIGHLIGHTS OF PRESCRIBING INFORMATION

These highlights do not include all the information needed to use ZYNRELEF® safely and effectively. See full prescribing information for ZYNRELEF.
ZYNRELEF (bupivacaine and meloxicam) extended-release solution, for instillation use
Initial U.S. Approval: 2021

WARNING: RISK OF SERIOUS CARDIOVASCULAR AND GASTROINTESTINAL EVENTS

See full prescribing information for complete boxed warning.

- Nonsteroidal anti-inflammatory drugs (NSAIDs) cause an increased risk of serious cardiovascular thrombotic events, including myocardial infarction and stroke, which can be fatal. This risk may occur early in treatment and may increase with duration of use (5.1)
- ZYNRELEF is contraindicated in the setting of coronary artery bypass graft (CABG) surgery (4, 5.1)
- NSAIDs cause an increased risk of serious gastrointestinal (GI) adverse events including bleeding, ulceration, and perforation of the stomach or intestines, which can be fatal. These events can occur at any time during use and without warning symptoms. Elderly patients and patients with a prior history of peptic ulcer disease and/or GI bleeding are at greater risk for serious GI events (5.2)

RECENT MAJOR CHANGES

Indications and Usage (1) | 01/2024
Dosage and Administration (2.1, 2.2, 2.3, 2.4, 2.5) | 09/2024
Warnings and Precautions (5.10, 5.14) | 11/2024

1 INDICATIONS AND USAGE

ZYNRELEF is indicated in adults for postsurgical analgesia for up to 72 hours after:

- soft tissue surgical procedures
- orthopedic surgical procedures
  - foot and ankle procedures
  - other orthopedic surgical procedures (e.g., total joint arthroplasty) in which direct exposure to articular cartilage is avoided [see Warnings and Precautions (5.10)]

Limitations of Use

Safety and efficacy have not been established in highly vascular surgeries, such as intrathoracic, large 4 or more level spinal, and head and neck procedures (1).

2 DOSAGE AND ADMINISTRATION

- ZYNRELEF is intended for single-dose administration only (2.1). Administer ZYNRELEF via instillation only.
- The toxic effects of local anesthetics are additive. Avoid additional use of local anesthetics within 96 hours following administration of ZYNRELEF (2.1).
- ZYNRELEF should only be prepared and administered with the components provided in the ZYNRELEF kit (2.1).
- ZYNRELEF is applied without a needle into the surgical site following final irrigation and suction and prior to suturing (2.1).
  - The recommended dose of ZYNRELEF is up to a maximum dose of 400 mg/12 mg (14 mL) (2.4).
- See Full Prescribing Information for important preparation and administration instructions, dose selection, and compatibility considerations (2.2, 2.3, 2.4, 2.5).

3 DOSAGE FORMS AND STRENGTHS

ZYNRELEF (bupivacaine and meloxicam) extended-release solution is available in four dosage strengths as single-dose glass vials:

- 400 mg bupivacaine and 12 mg meloxicam
- 300 mg bupivacaine and 9 mg meloxicam
- 200 mg bupivacaine and 6 mg meloxicam
- 60 mg bupivacaine and 1.8 mg meloxicam

4 CONTRAINDICATIONS

ZYNRELEF is contraindicated for:

- Patients with a known hypersensitivity (e.g., anaphylactic reactions and serious skin reactions) to any local anesthetic agent of the amide-type, NSAIDs, or to any of the other components of ZYNRELEF (4)
- Patients with a history of asthma, urticaria, or other allergic-type reactions after taking aspirin or other NSAIDs. Severe, sometimes fatal, anaphylactic reactions to NSAIDs have been reported in such patients (4)
- Patients undergoing obstetrical paracervical block anesthesia (4)
- Patients undergoing coronary artery bypass graft (CABG) surgery (4)

5 WARNINGS AND PRECAUTIONS

Dose-Related Toxicity: Monitor cardiovascular and respiratory vital signs and patient's state of consciousness after application of ZYNRELEF (5.3).

When using ZYNRELEF with other local anesthetics, overall local anesthetic exposure must be considered through 72 hours (5.3).

Hepatotoxicity: If abnormal liver tests persist or worsen, perform a clinical evaluation of the patient (5.5).

Hypertension: Patients taking some antihypertensive medications may have impaired response to these therapies when taking NSAIDs. Monitor blood pressure (5.6, 7).

Heart Failure and Edema: Avoid use of ZYNRELEF in patients with severe heart failure unless benefits are expected to outweigh risk of worsening heart failure (5.7).

Renal Toxicity: Monitor renal function in patients with renal or hepatic impairment, heart failure, dehydration, or hypovolemia. Avoid use of ZYNRELEF in patients with advanced renal disease unless benefits are expected to outweigh risk of worsening renal function (5.8).

Anaphylactic Reactions: Seek emergency help if an anaphylactic reaction occurs (5.9).

Risk of Joint Cartilage Necrosis and Degeneration with Unapproved Intra-articular Use: Animal studies evaluating the effects of ZYNRELEF following intra-articular administration in the knee joint demonstrated cartilage necrosis and degeneration (5.10, 13.2).

Chondrolysis: Limit exposure to articular cartilage due to the potential risk of chondrolysis (5.11).

Methemoglobinemia: Cases of methemoglobinemia have been reported in association with local anesthetic use (5.12).

Serious Skin Reactions: NSAIDs, including meloxicam, can cause serious skin adverse reactions. If symptoms present, evaluate clinically (5.14).

Drug Reaction with Eosinophilia and Systemic Symptoms (DRESS): If symptoms are present, evaluate clinically (5.15).

Fetal Toxicity: Limit use of NSAIDs, including ZYNRELEF, between about 20 to 30 weeks in pregnancy due to the risk of oligohydramnios/fetal renal dysfunction. Avoid use of NSAIDs in women at about 30 weeks gestation and later in pregnancy due to the risks of oligohydramnios/fetal renal dysfunction and premature closure of the ductus arteriosus (5.16, 8.1).

Hematologic Toxicity: Monitor hemoglobin or hematocrit in patients with any signs or symptoms of anemia (5.17).

6 ADVERSE REACTIONS

Most common adverse reactions (incidence ≥5%) are:

- Soft tissue procedures: vomiting (6.1).
- Orthopedic procedures: constipation and headache (6.1).

To report SUSPECTED ADVERSE REACTIONS, contact Heron Therapeutics, Inc. at 1-844-437-6611 and www.ZYNRELEF.com or FDA at 1-800-FDA-1088 or www.fda.gov/medwatch.

7 DRUG INTERACTIONS

Drugs that Interfere with Hemostasis (e.g., warfarin, aspirin, SSRIs/SNRIs): Monitor patients for bleeding who are concomitantly taking ZYNRELEF with drugs that interfere with hemostasis (7.2).

ACE Inhibitors, Angiotensin Receptor Blockers (ARBs), or Beta-Blockers: Concomitant use with ZYNRELEF may diminish the antihypertensive effect of these drugs. Monitor blood pressure (7.2).

ACE Inhibitors and ARBs: Concomitant use with ZYNRELEF in elderly, volume-depleted, or those with renal impairment may result in deterioration of renal function. In such high-risk patients, monitor for signs of worsening renal function (7.2).

Diuretics: NSAIDs can reduce natriuretic effect of furosemide and thiazide diuretics. Monitor patients to assure diuretic efficacy including antihypertensive effect (7.2).

8 USE IN SPECIFIC POPULATIONS

Infertility: NSAIDs are associated with reversible infertility. Consider avoidance of ZYNRELEF in women who have difficulties conceiving (8.3).

Severe Hepatic Impairment: Only use if benefits are expected to outweigh risks; monitor for signs of worsening liver function (8.6).

Severe Renal Impairment: Not recommended (8.7).

FULL PRESCRIBING INFORMATION

WARNING: RISK OF SERIOUS CARDIOVASCULAR AND GASTROINTESTINAL EVENTS

Cardiovascular Thrombotic Events

- Nonsteroidal anti-inflammatory drugs (NSAIDs) cause an increased risk of serious cardiovascular thrombotic events, including myocardial infarction and stroke, which can be fatal. This risk may occur early in treatment and may increase with duration of use [see Warnings and Precautions (5.1)].
- ZYNRELEF is contraindicated in the setting of coronary artery bypass graft (CABG) surgery [see Contraindications (4) and Warnings and Precautions (5.1)].

Gastrointestinal Bleeding, Ulceration, and Perforation

- NSAIDs cause an increased risk of serious gastrointestinal (GI) adverse events including bleeding, ulceration, and perforation of the stomach or intestines, which can be fatal. These events can occur at any time during use and without warning symptoms. Elderly patients and patients with a prior history of peptic ulcer disease and/or GI bleeding are at greater risk for serious GI events [see Warnings and Precautions (5.2)].

1 INDICATIONS AND USAGE

ZYNRELEF is indicated in adults for postsurgical analgesia for up to 72 hours after:

- soft tissue surgical procedures
- orthopedic surgical procedures
  - foot and ankle procedures
  - other orthopedic surgical procedures (e.g., total joint arthroplasty) in which direct exposure to articular cartilage is avoided [see Warnings and Precautions (5.10)]

Limitations of Use

Safety and efficacy have not been established in highly vascular surgeries, such as intrathoracic, large 4 or more level spinal, and head and neck procedures.

2 DOSAGE AND ADMINISTRATION

2.1 Important Dosage and Administration Information

ADMINISTER ZYNRELEF VIA INSTILLATION ONLY.

- ZYNRELEF should not be administered via the following routes.
  - Epidural
  - Intrathecal
  - Intravascular
  - Intra-articular [see Warnings and Precautions (5.10), Nonclinical Toxicology (13.2)]
  - Regional nerve blocks
  - Pre-incisional or pre-procedural locoregional anesthetic techniques.
- ZYNRELEF is intended for single-dose administration only.
- As there is a potential risk of severe, life-threatening adverse reactions associated with the administration of bupivacaine, ZYNRELEF should be administered in a setting where trained personnel and equipment are available to promptly treat patients who show evidence of neurologic or cardiac toxicity [see Overdosage (10)].
- The toxic effects of local anesthetics are additive. Avoid additional use of local anesthetics within 96 hours following administration of ZYNRELEF.
- Avoid intravascular administration of ZYNRELEF. Convulsions and cardiac arrest have occurred following accidental intravascular injection of bupivacaine and other amide-containing products.
- Limit exposure to articular cartilage due to the potential risk of chondrolysis [see Warnings and Precautions (5.11)].
- ZYNRELEF is a viscous solution supplied as a kit consisting of a single-dose glass vial, and the following sterile components: Luer lock syringe(s), a vented vial spike or vial access needle, Luer lock cone-shaped applicator(s), and syringe tip cap(s). ZYNRELEF should only be prepared and administered with the components provided in the ZYNRELEF kit. See the ZYNRELEF Instructions for Use included in the kit for complete administration instructions with illustrations.
- The contents of the ZYNRELEF vial are sterile. The vial exterior is not sterile. Follow your facility's standard operating procedures regarding aseptic drug preparation.
- Each ZYNRELEF vial contains overfill to compensate for residual amounts that remain in the vial, vented vial spike or vial access needle, Luer lock applicator, and syringe(s) during drug withdrawal and administration.
- ZYNRELEF is applied without a needle into the surgical site after placement of implant(s) (if applicable), following final irrigation and suctioning, and prior to suturing of each layer, when multiple tissue layers are involved.
- When ZYNRELEF comes in contact with moisture in the tissues, it becomes more viscous, allowing it to stay in place.
- ZYNRELEF does not degrade sutures. When tying knots with monofilament sutures, contact with ZYNRELEF may cause knots to loosen or untie due to the viscosity of ZYNRELEF. In vitro studies showed an increase in elasticity with monofilament sutures exposed to ZYNRELEF with unknown clinical significance. Minimize administration of ZYNRELEF near the incision line and wipe off excess ZYNRELEF from the skin prior to suturing. Three (3) or more knots ending in a multi-throw knot (e.g., a Surgeon's knot) are recommended with monofilament sutures. Braided or barbed sutures are recommended, especially for closure of deeper layers.

2.2 Preparation Instructions

See the ZYNRELEF Instructions for Use included in the kit for complete administration instructions with illustrations.

1. ZYNRELEF is a clear, pale yellow to yellow, viscous liquid. Visually inspect the ZYNRELEF vial for particulate matter and discoloration. Obtain a new vial if particulate matter or discoloration is observed.
2. Prepare vial for filling of syringe(s) by attaching vented vial spike or vial access needle.
3. Syringe attachment for product withdrawal:
  - For vented vial spike, fill syringe with air prior to attaching syringe. Attach syringe to vented vial spike, invert vial and syringe to allow product to fill the vial neck, then push air into vented vial spike prior to withdrawing ZYNRELEF from vial.
  - For vial access needle, do not fill syringe with air prior to attaching syringe. Attach syringe to vial access needle, then invert vial and syringe to allow product to fill the vial neck prior to withdrawing ZYNRELEF from vial.
4. Withdraw dose of ZYNRELEF into syringe. (The dose volume takes into account the potential residual volume in the components.). Withdrawal time using the vial access needle is faster than the vented vial spike.
  Nominal Dose of Bupivacaine / Meloxicam | Number of Syringes and LLAs [LLA: Luer lock cone-shaped applicator] Per Dose | Volume to be Withdrawn
  60 mg/ 1.8 mg | 1 | 2.3 mL (using 3 mL syringe provided)
  200 mg / 6 mg | 1 | 7 mL (using 12 mL syringe provided)
  300 mg/ 9 mg | 1 | 10.5 mL (using 12 mL syringe provided)
  400 mg/ 12 mg | 2 | 14 mL (using two 12 mL syringes provided, 7 mL ZYNRELEF per syringe)
5. Repeat steps 1-3 for more than one syringe.
6. Prepare product immediately prior to use and apply syringe tip cap if needed until product delivery.

2.3 Administration Instructions

Before administration, remove the syringe tip cap and attach the Luer lock cone-shaped applicator to the syringe.

1. Using the Luer lock cone-shaped applicator attached to the syringe, apply ZYNRELEF to the tissues within the surgical site as follows:
  - For soft tissue procedures, apply ZYNRELEF into the wound prior to closure of each layer within the surgical space.
    - For abdominal procedures, apply after closure of the peritoneum (if applicable) and avoid administration below the peritoneum.
  - In general for orthopedic procedures, apply ZYNRELEF into the wound and on the periosteum from the proximal to the distal ends of the wound (i.e., beyond the boney repair).
    - For total joint arthroplasty, apply ZYNRELEF directly into the joint capsule, onto the periosteum, and the antero-, medial-, and lateral tissues (if applicable), after placement of the component(s).
    - For spinal procedures, apply ZYNRELEF after closure of the paraspinal musculature and again after closure of the subcutaneous fascia. ZYNRELEF must not be applied to the dura or spinal cord.
2. Only apply ZYNRELEF to the tissue layers below the skin incision and not directly onto the subdermal layer or the skin. Minimize administration of ZYNRELEF near the incision line.
3. Use only the amount necessary to coat the tissues, such that ZYNRELEF does not leak from the surgical wound after closure. Wipe off excess ZYNRELEF from the skin prior to or during closure of the wound.

2.4 Dosing Instructions

As a general guidance in selecting the proper dosing of ZYNRELEF, the following examples of dosing are provided:

- For soft tissue surgical procedures, such as:
  - open inguinal herniorrhaphy: up to 10.5 mL to deliver 300 mg of bupivacaine and 9 mg of meloxicam [see Clinical Studies (14)];
  - abdominoplasty: up to 14 mL to deliver 400 mg of bupivacaine and 12 mg of meloxicam [see Clinical Studies (14)];
  - Cesarean section: up to 14 mL to deliver 400 mg of bupivacaine and 12 mg of meloxicam [see Clinical Studies (14)];
  - augmentation mammoplasty: up to 7 mL per side to deliver total of 400 mg of bupivacaine and 12 mg of meloxicam [see Clinical Studies (14)].
- For orthopedic surgical procedures, such as:
  - bunionectomy: up to 2.3 mL to deliver 60 mg of bupivacaine and 1.8 mg of meloxicam [see Clinical Studies (14)];
  - total knee arthroplasty: up to 14 mL to deliver 400 mg of bupivacaine and 12 mg of meloxicam [see Clinical Studies (14)];
  - total shoulder arthroplasty: up to 14 mL to deliver 400 mg of bupivacaine and 12 mg of meloxicam [see Clinical Studies (14)];
  - 1- to 3-level spinal surgery: up to 7 mL to deliver 200 mg bupivacaine and 6 mg meloxicam [see Clinical Studies (14)].

2.5 Compatibility Considerations

- Do not dilute ZYNRELEF.
- ZYNRELEF is a nonaqueous solution. It cannot be mixed with water, saline, or other local anesthetics as the product will become more viscous and difficult to administer.
- When a topical antiseptic such as povidone iodine (e.g., Betadine®) is applied, the site should be allowed to dry before a local anesthetic, including ZYNRELEF, is administered into the site.
- When administered in recommended doses and concentrations, ZYNRELEF does not ordinarily produce irritation or tissue damage.

ZYNRELEF is compatible with:

- All components of the ZYNRELEF kit, including syringes, Luer lock cone-shaped applicator, vented vial spike, vial access needle, and syringe tip caps.
- Surgical mesh materials, including polypropylene (Prolene®), Gore-tex, and polyester.
- Silicone membranes.
- Bone cement.
- Metal alloys used in surgical implants.

3 DOSAGE FORMS AND STRENGTHS

ZYNRELEF (bupivacaine and meloxicam) extended-release solution is a sterile, clear, pale-yellow to yellow, viscous liquid in a single-dose vial containing 29.25 mg/mL bupivacaine and 0.88 mg/mL meloxicam and is available in the following four presentations:

- 14 mL containing 400 mg bupivacaine and 12 mg meloxicam
- 10.5 mL containing 300 mg bupivacaine and 9 mg meloxicam
- 7 mL containing 200 mg bupivacaine and 6 mg meloxicam
- 2.3 mL containing 60 mg bupivacaine and 1.8 mg meloxicam

4 CONTRAINDICATIONS

ZYNRELEF is contraindicated in:

- Patients with a known hypersensitivity (e.g., anaphylactic reactions and serious skin reactions) to any local anesthetic agent of the amide-type, NSAIDs, or to any of the other components of ZYNRELEF [see Warnings and Precautions (5.9, 5.14)].
- Patients with a history of asthma, urticaria, or other allergic-type reactions after taking aspirin or other NSAIDs. Severe, sometimes fatal, anaphylactic reactions to NSAIDs have been reported in such patients [see Warnings and Precautions (5.9)].
- Patients undergoing obstetrical paracervical block anesthesia. The use of bupivacaine in this technique has resulted in fetal bradycardia and death [see Use in Specific Populations (8.1)].
- Patients undergoing coronary artery bypass graft (CABG) surgery [see Warnings and Precautions (5.1)].

5 WARNINGS AND PRECAUTIONS

5.1 Cardiovascular (CV) Thrombotic Events with NSAID Use

Clinical trials of several COX-2 selective and nonselective NSAIDs of up to three years duration have shown an increased risk of serious cardiovascular thrombotic events, including myocardial infarction (MI) and stroke, which can be fatal. Based on available data, it is unclear that the risk for CV thrombotic events is similar for all NSAIDs. The relative increase in serious CV thrombotic events over baseline conferred by NSAID use appears to be similar in those with and without known CV disease or risk factors for CV disease. However, patients with known CV disease or risk factors had a higher absolute incidence of excess serious CV thrombotic events, due to their increased baseline rate. Some observational studies found that this increased risk of serious CV thrombotic events began as early as the first weeks of treatment. The increase in CV thrombotic risk has been observed most consistently at higher doses. The risk of these events following single-dose local application of ZYNRELEF is uncertain.

To minimize the potential risk for an adverse CV event in NSAID-treated patients, do not exceed the recommended dose. Physicians and patients should remain alert for the development of such events following treatment with ZYNRELEF, even in the absence of previous CV symptoms. Inform patients about the signs and symptoms of serious CV events and the steps to take if they occur.

There is no consistent evidence that concurrent use of aspirin mitigates the increased risk of serious CV thrombotic events associated with NSAID use. The concurrent use of aspirin and an NSAID, such as meloxicam, increases the risk of serious gastrointestinal (GI) events [see Warnings and Precautions (5.2)].

Coronary Artery Bypass Graft (CABG) Surgery

Two large, controlled clinical trials of a COX-2 selective NSAID for the treatment of pain in the first 10-14 days following CABG surgery found an increased incidence of myocardial infarction and stroke. ZYNRELEF is contraindicated in the setting of CABG [see Contraindications (4)].

Post-MI Patients

Observational studies conducted in the Danish National Registry have demonstrated that patients treated with NSAIDs in the post-MI period were at increased risk of reinfarction, CV-related death, and all-cause mortality beginning in the first week of treatment. In this same cohort, the incidence of death in the first year post-MI was 20 per 100 person years in NSAID-treated patients compared to 12 per 100 person years in non-NSAID exposed patients. Although the absolute rate of death declined somewhat after the first year post-MI, the increased relative risk of death in NSAID users persisted over at least the next four years of follow-up.

Avoid the use of ZYNRELEF in patients with a recent MI unless the benefits are expected to outweigh the risk of recurrent CV thrombotic events. If ZYNRELEF is used in patients with a recent MI, monitor patients for signs of cardiac ischemia. The risk of these events following single-dose local application of ZYNRELEF is uncertain.

5.2 Gastrointestinal Bleeding, Ulceration, and Perforation with NSAID Use

NSAIDs, including meloxicam in ZYNRELEF, can cause serious gastrointestinal (GI) adverse events including inflammation, bleeding, ulceration, and perforation of the esophagus, stomach, small intestine, or large intestine, which can be fatal. These serious adverse events can occur at any time, with or without warning symptoms, in patients treated with NSAIDs. Only one in five patients who develop a serious upper GI adverse event on NSAID therapy is symptomatic. Upper GI ulcers, gross bleeding, or perforation caused by NSAIDs occurred in approximately 1% of patients treated for 3 to 6 months, and in about 2 to 4% of patients treated for one year. However, even short-term NSAID therapy is not without risk.

Risk Factors for GI Bleeding, Ulceration, and Perforation

Patients with a prior history of peptic ulcer disease and/or GI bleeding who used NSAIDs have a greater than 10-fold increased risk for developing a GI bleed compared to patients without these risk factors. Other factors that increase the risk of GI bleeding in patients treated with NSAIDs include longer duration of NSAID therapy; concomitant use of oral corticosteroids, aspirin, anticoagulants, or selective serotonin reuptake inhibitors (SSRIs); smoking; use of alcohol; older age; and poor general health status. Most post marketing reports of fatal GI events occurred in elderly or debilitated patients. Additionally, patients with advanced liver disease and/or coagulopathy are at increased risk for GI bleeding.

Strategies to Minimize the GI Risks in NSAID-treated Patients

- Use the recommended dose for each indicated surgical procedure.
- Avoid administration of analgesic doses of more than one NSAID at a time. If additional NSAID medication is indicated in the postoperative period, monitor patients for signs and symptoms of NSAID-related GI adverse reactions.
- Avoid use in patients at higher risk unless benefits are expected to outweigh the increased risk of bleeding. For such patients, as well as those with active GI bleeding, consider alternate therapies other than NSAIDs.
- Remain alert for signs and symptoms of GI ulceration and bleeding following treatment with ZYNRELEF.
- If a serious GI adverse event is suspected, promptly initiate evaluation and treatment.
- In the setting of concomitant use of low-dose aspirin for cardiac prophylaxis, monitor patients more closely for evidence of GI bleeding [see Drug Interactions (7)].

5.3 Dose-Related Toxicity

The safety and effectiveness of local anesthetics depend on proper dosage, correct technique, adequate precautions, and readiness for emergencies. The toxic effects of local anesthetics are additive. Avoid additional local anesthetic administration within 96 hours following ZYNRELEF instillation. If additional local anesthetic administration with ZYNRELEF cannot be avoided based on clinical need, monitor patients for neurologic and cardiovascular effects related to local anesthetic systemic toxicity. Careful and constant monitoring of cardiovascular and respiratory (adequacy of ventilation) vital signs and the patient's state of consciousness should be performed after administration of ZYNRELEF.

Possible early warning signs of central nervous system (CNS) toxicity are restlessness, anxiety, incoherent speech, lightheadedness, numbness and tingling of the mouth and lips, metallic taste, tinnitus, dizziness, blurred vision, tremors, twitching, CNS depression, or drowsiness. Delay in proper management of dose-related toxicity, underventilation from any cause, and/or altered sensitivity may lead to the development of acidosis, cardiac arrest, and, possibly, death.

5.4 Risk of Use in Patients with Impaired Cardiovascular Function

Patients with impaired cardiovascular function (e.g., hypotension, heart block) may be less able to compensate for functional changes associated with the prolongation of AV conduction produced by ZYNRELEF. Monitor patients closely for blood pressure, heart rate, and ECG changes.

5.5 Hepatotoxicity

Local Anesthetics, Including Bupivacaine

Because amide-type local anesthetics such as bupivacaine are metabolized by the liver, these drugs should be used cautiously in patients with hepatic disease. Patients with severe hepatic disease, because of their inability to metabolize local anesthetics normally, are at a greater risk of developing toxic plasma concentrations.

NSAIDs

Elevations of ALT or AST (three or more times the upper limit of normal [ULN]) have been reported in approximately 1% of NSAID-treated patients in clinical trials. In addition, rare, sometimes fatal, cases of severe hepatic injury, including fulminant hepatitis, liver necrosis, and hepatic failure have been reported.

Elevations of ALT or AST (less than three times ULN) may occur in up to 15% of patients treated with NSAIDs including meloxicam. The risk of these events following single-dose local application of ZYNRELEF is uncertain.

Inform patients of the warning signs and symptoms of hepatotoxicity (e.g., nausea, fatigue, lethargy, diarrhea, pruritus, jaundice, right upper quadrant tenderness, and "flu-like" symptoms). If clinical signs and symptoms consistent with liver disease develop, or if systemic manifestations occur (e.g., eosinophilia, rash, etc.), perform a clinical evaluation of the patient [see Use in Specific Populations (8.6) and Clinical Pharmacology (12.3)].

5.6 Hypertension

NSAIDs, including meloxicam in ZYNRELEF, can lead to new onset of hypertension or worsening of preexisting hypertension, either of which may contribute to the increased incidence of CV events. Patients taking angiotensin converting enzyme (ACE) inhibitors, thiazide diuretics, or loop diuretics may have impaired response to these therapies when taking NSAIDs [see Drug Interactions (7)].

Monitor blood pressure (BP) after administration of ZYNRELEF.

5.7 Heart Failure and Edema

The Coxib and traditional NSAID Trialists' Collaboration meta-analysis of randomized controlled trials demonstrated an approximately two-fold increase in hospitalizations for heart failure in COX-2 selective-treated patients and nonselective NSAID-treated patients compared to placebo-treated patients. In a Danish National Registry study of patients with heart failure, NSAID use increased the risk of MI, hospitalization for heart failure, and death.

Additionally, fluid retention and edema have been observed in some patients treated with NSAIDs. Use of meloxicam may blunt the CV effects of several therapeutic agents used to treat these medical conditions (e.g., diuretics, ACE inhibitors, or angiotensin receptor blockers [ARBs]) [see Drug Interactions (7)]. The risk of these events following single-dose local application of ZYNRELEF is uncertain.

Avoid the use of ZYNRELEF in patients with severe heart failure unless the benefits are expected to outweigh the risk of worsening heart failure. If ZYNRELEF is used in patients with severe heart failure, monitor patients for signs of worsening heart failure.

5.8 Renal Toxicity and Hyperkalemia

Renal Toxicity

ZYNRELEF is a single-use product that contains an NSAID. Long-term administration of NSAIDs has resulted in renal papillary necrosis, renal insufficiency, acute renal failure, and other renal injury.

Renal toxicity has also been seen in patients in whom renal prostaglandins have a compensatory role in the maintenance of renal perfusion. In these patients, administration of an NSAID may cause a dose-dependent reduction in prostaglandin formation and, secondarily, in renal blood flow, which may precipitate overt renal decompensation. Patients at greatest risk of this reaction are those with impaired renal function, dehydration, hypovolemia, heart failure, liver dysfunction, those taking diuretics and ACE inhibitors or ARBs, and the elderly. Discontinuation of NSAID therapy is usually followed by recovery to the pretreatment state.

The renal effects of meloxicam may hasten the progression of renal dysfunction in patients with preexisting renal disease. Because some meloxicam metabolites are excreted by the kidney, monitor patients for signs of worsening renal function.

Correct volume status in dehydrated or hypovolemic patients prior to initiating ZYNRELEF. Monitor renal function in patients with renal or hepatic impairment, heart failure, dehydration, or hypovolemia during use of ZYNRELEF [see Drug Interactions (7)]. Avoid the use of ZYNRELEF in patients with advanced renal disease unless the benefits are expected to outweigh the risk of worsening renal function. If ZYNRELEF is used in patients with advanced renal disease, monitor patients for signs of worsening renal function [see Clinical Pharmacology (12.3)].

Hyperkalemia

Increases in serum potassium concentration, including hyperkalemia, have been reported with use of NSAIDs, even in some patients without renal impairment. In patients with normal renal function, these effects have been attributed to a hyporeninemic-hypoaldosteronism state.

5.9 Anaphylactic Reactions

NSAIDs

Meloxicam, contained in ZYNRELEF, has been associated with anaphylactic reactions in patients with and without known hypersensitivity to meloxicam and in patients with aspirin-sensitive asthma [see Contraindications (4)].

Seek emergency help if an anaphylactic reaction occurs.

5.10 Risk of Joint Cartilage Necrosis with Unapproved Intra-articular Use

The safety and effectiveness of intra-articular use of ZYNRELEF in orthopedic surgical procedures other than for foot and ankle procedures have not been established, and ZYNRELEF is not approved for use via other intra-articular administration routes. Animal studies evaluating the effects of ZYNRELEF following intra-articular administration in the knee joint demonstrated cartilage necrosis and degeneration [see Nonclinical Toxicology (13.2)].

5.11 Chondrolysis

Limit exposure to articular cartilage due to the potential risk of chondrolysis.

Intra-articular infusions of local anesthetics, following arthroscopic and other surgical procedures is an unapproved use, and there have been post marketing reports of chondrolysis in patients receiving such infusions. The majority of reported cases of chondrolysis have involved the shoulder joint; cases of glenohumeral chondrolysis have been described in pediatric patients and adult patients following intra-articular infusions of local anesthetics with and without epinephrine for periods of 48 to 72 hours. There is insufficient information to determine whether shorter infusion periods are associated with chondrolysis. The time of onset of symptoms, such as joint pain, stiffness, and loss of motion can be variable, but may begin as early as the 2nd month after surgery. Currently, there is no effective treatment for chondrolysis; patients who have experienced chondrolysis have required additional diagnostic and therapeutic procedures and some required arthroplasty or shoulder replacement.

5.12 Methemoglobinemia

Cases of methemoglobinemia have been reported in association with local anesthetic use. Although all patients are at risk for methemoglobinemia, patients with glucose-6-phosphate dehydrogenase deficiency, congenital or idiopathic methemoglobinemia, cardiac or pulmonary compromise, infants under 6 months of age, and concurrent exposure to oxidizing agents or their metabolites are more susceptible to developing clinical manifestations of the condition. If local anesthetics must be used in these patients, close monitoring for symptoms and signs of methemoglobinemia is recommended. Signs of methemoglobinemia may occur immediately or may be delayed some hours after exposure, and are characterized by a cyanotic skin discoloration and/or abnormal coloration of the blood.

Methemoglobin levels may continue to rise; therefore, immediate treatment is required to avert more serious central nervous system and cardiovascular adverse effects, including seizures, coma, arrhythmias, and death. Discontinue any oxidizing agents. Depending on the severity of the signs and symptoms, patients may respond to supportive care, i.e., oxygen therapy, hydration. A more severe clinical presentation may require treatment with methylene blue, exchange transfusion, or hyperbaric oxygen.

5.13 Exacerbation of Asthma Related to Aspirin Sensitivity

A subpopulation of patients with asthma may have aspirin-sensitive asthma, which may include: chronic rhinosinusitis complicated by nasal polyps; severe, potentially fatal bronchospasm; and/or intolerance to aspirin and other NSAIDs. Because cross-reactivity between aspirin and other NSAIDs has been reported in such aspirin-sensitive patients, NSAIDs are contraindicated in patients with this form of aspirin sensitivity [see Contraindications (4)]. When ZYNRELEF is used in patients with preexisting asthma (without known aspirin sensitivity), monitor patients for exacerbation of asthma symptoms.

5.14 Serious Skin Reactions

NSAIDs, including meloxicam, can cause serious skin adverse reactions such as exfoliative dermatitis, Stevens-Johnson Syndrome (SJS), and toxic epidermal necrolysis (TEN), which can be fatal. NSAIDs can also cause fixed drug eruption (FDE). FDE may present as a more severe variant known as generalized bullous fixed drug eruption (GBFDE), which can be life-threatening. These serious events may occur without warning. Inform patients about the signs and symptoms of serious skin reactions.

ZYNRELEF is contraindicated in patients with previous serious skin reactions to NSAIDs [see Contraindications (4)].

5.15 Drug Reaction with Eosinophilia and Systemic Symptoms (DRESS)

Drug Reaction with Eosinophilia and Systemic Symptoms (DRESS) has been reported in patients taking NSAIDs such as ZYNRELEF. Some of these events have been fatal or life-threatening. DRESS typically, although not exclusively, presents with fever, rash, lymphadenopathy, and/or facial swelling. Other clinical manifestations may include hepatitis, nephritis, hematological abnormalities, myocarditis, or myositis. Sometimes symptoms of DRESS may resemble an acute viral infection. Eosinophilia is often present. Because this disorder is variable in its presentation, other organ systems not noted here may be involved. It is important to note that early manifestations of hypersensitivity, such as fever or lymphadenopathy, may be present even though rash is not evident. If such signs or symptoms are present, evaluate the patient immediately and treat as clinically indicated.

5.16 Fetal Toxicity

Premature Closure of Fetal Ductus Arteriosus

Avoid use of NSAIDs, including ZYNRELEF, in pregnant women at about 30 weeks gestation and later. NSAIDs, including ZYNRELEF, increase the risk of premature closure of the fetal ductus arteriosus at approximately this gestational age.

Oligohydramnios/Neonatal Renal Impairment

Use of NSAIDs, including ZYNRELEF, at about 20 weeks gestation or later in pregnancy may cause fetal renal dysfunction leading to oligohydramnios and, in some cases, neonatal renal impairment. These adverse outcomes are seen, on average, after days to weeks of treatment, although oligohydramnios has been infrequently reported as soon as 48 hours after NSAID initiation. Oligohydramnios is often, but not always, reversible with treatment discontinuation. Complications of prolonged oligohydramnios may, for example, include limb contractures and delayed lung maturation. In some postmarketing cases of impaired neonatal renal function, invasive procedures such as exchange transfusion or dialysis were required.

If NSAID treatment is necessary between about 20 weeks and 30 weeks gestation, limit ZYNRELEF use to the lowest effective dose. Because meloxicam can be detected in plasma beyond 48 hours after administration of ZYNRELEF, consider ultrasound monitoring for oligohydramnios. If oligohydramnios occurs, follow up according to clinical practice [see Use in Specific Populations (8.1)].

5.17 Hematologic Toxicity

Anemia has occurred in NSAID-treated patients. This may be due to occult or gross blood loss, fluid retention, or an incompletely described effect on erythropoiesis. If a patient treated with ZYNRELEF has any signs or symptoms of anemia, monitor hemoglobin or hematocrit.

NSAIDs, including meloxicam, may increase the risk of bleeding events. Co-morbid conditions such as coagulation disorders or concomitant use of warfarin, other anticoagulants, antiplatelet agents (e.g., aspirin), serotonin reuptake inhibitors (SSRIs) and serotonin norepinephrine reuptake inhibitors (SNRIs) may increase this risk. Monitor these patients for signs of bleeding [see Drug Interactions (7)].

5.18 Masking of Inflammation and Fever

The pharmacological activity of ZYNRELEF in reducing inflammation, and possibly fever, may diminish the utility of diagnostic signs in detecting infections.

6 ADVERSE REACTIONS

The following serious adverse reactions have been associated with bupivacaine HCl or meloxicam and are discussed in greater detail in other sections of the labeling:

- Cardiovascular System Reactions [see Warnings and Precautions (5.1, 5.4)]
- Gastrointestinal Bleeding, Ulceration, and Perforation [see Warnings and Precautions (5.2)]
- Dose-Related Toxicity [see Warnings and Precautions (5.3)]
- Hepatotoxicity [see Warnings and Precautions (5.5)]
- Hypertension [see Warnings and Precautions (5.6)]
- Heart Failure and Edema [see Warnings and Precautions (5.7)]
- Renal Toxicity and Hyperkalemia [see Warnings and Precautions (5.8)]
- Anaphylactic Reactions [see Warnings and Precautions (5.9)]
- Chondrolysis [see Warnings and Precautions (5.11)]
- Methemoglobinemia [see Warnings and Precautions (5.12)]
- Exacerbation of Asthma Related to Aspirin Sensitivity [see Warnings and Precautions (5.13)]
- Serious Skin Reactions [see Warnings and Precautions (5.14)]
- Drug Reaction with Eosinophilia and Systemic Toxicity (DRESS) [see Warnings and Precautions (5.15)]
- Fetal Toxicity [see Warnings and Precautions (5.16)]
- Hematologic Toxicity [see Warnings and Precautions (5.17)]

6.1 Clinical Trials Experience

Because clinical studies are conducted under widely varying conditions, adverse reaction rates observed in the clinical trials of a drug cannot be directly compared to rates in the clinical studies of another drug and may not reflect the rates observed in practice.

The safety of ZYNRELEF has been evaluated in a total of 1627 patients undergoing various surgical procedures across 14 clinical studies including 7 randomized, double-blind, bupivacaine- and placebo-controlled and saline placebo-controlled studies designed to investigate ZYNRELEF to reduce postoperative pain for 72 hours and the need for opioid analgesics, of whom 1183 received ZYNRELEF by instillation. Patients treated with ZYNRELEF ranged in age from 18 to 85 years (median age 51 years), with 53.0% female, 82.1% White, 13.7% African-American, and 4.3% all other races.

Common Adverse Reactions

The safety of ZYNRELEF has been evaluated in 1064 patients who received ZYNRELEF in single doses up to 400 mg/12 mg via instillation into the surgical site, including 533 patients undergoing a soft tissue surgical procedure (herniorrhaphy, abdominoplasty, augmentation mammoplasty, or Cesarean section) and 531 patients undergoing an orthopedic surgical procedure (bunionectomy, total knee arthroplasty, total shoulder arthroplasty, or lumbar spinal surgery). The most common adverse reactions (incidence greater than or equal to 5% and higher than placebo) following ZYNRELEF administration among patients undergoing soft tissue procedures was vomiting and among patients undergoing orthopedic procedures were constipation and headache.

The safety of ZYNRELEF as part of a scheduled, non-opioid multimodal analgesic regimen including 1 or more other NSAIDs has been evaluated in a total of 473 patients undergoing soft tissue procedures or orthopedic procedures. NSAIDs included ibuprofen, ketorolac, and celecoxib. In these studies, the most common adverse reactions (incidence of greater than or equal to 2%) potentially associated with NSAIDs were pruritus and postoperative anemia. Rare but clinically serious NSAID-related adverse events, including peptic ulcer hemorrhage, gastritis requiring hospitalization, hematemesis and melena, gastrointestinal hemorrhage, and increased hepatic enzymes, were observed in subjects with predisposing risk factors (i.e., concomitant comorbidities and/or on concomitant medications such as anticoagulant and/or antiplatelet medications) that increased the risk for NSAID-related gastrointestinal toxicity.

Adverse Reactions Reported in Phase 3 and 2b Placebo-controlled Trials

Three randomized, bupivacaine-controlled and saline placebo-controlled studies were conducted in patients undergoing bunionectomy (STUDY 1, Table 1 and Table 2), open inguinal herniorrhaphy (STUDY 2, Table 3), and total knee arthroplasty (STUDY 3, Table 4). The bunionectomy procedures in STUDY 1 were performed under regional anesthesia, a lidocaine Mayo block, and intravenous sedation. The herniorrhaphy procedures in STUDY 2 were performed under general anesthesia. The total knee arthroplasty procedures in STUDY 3 were performed under either general or spinal anesthesia. Patients in STUDY 1 and STUDY 2 were allowed opioid rescue with intravenous (IV) morphine and oral oxycodone, and/or non-opioid rescue with oral acetaminophen. Patients in STUDY 3 were pretreated with oral pregabalin and acetaminophen, and allowed opioid rescue with IV morphine and oral oxycodone postoperatively.

Table 1. Adverse Reactions with ZYNRELEF in Study 1 (Bunionectomy) Occurring with ≥5% Incidence and Higher than with Saline Placebo
Preferred Term | Saline Placebo (N=101), % | Bupivacaine HCl 50 mg (N=154), % | ZYNRELEF 60 mg/1.8 mg (N=157), %
Dizziness | 18 | 23 | 22
Incision site edema | 13 | 14 | 17
Headache | 10 | 13 | 14
Incision site erythema | 8 | 12 | 13
Bradycardia | 6 | 8 | 8
Impaired healing | 1 | 4 | 6
Muscle twitching | 5 | 5 | 6

In STUDY 1, bone healing was assessed by X-ray on Days 28 and 42. There was no clinically meaningful difference in bone healing between treatment groups. A total of 4 subjects had delayed bone healing: 1 in the ZYNRELEF group, 1 in the saline placebo group, and 2 in the bupivacaine HCl group.

The incidence of local inflammatory adverse events was higher in the ZYNRELEF group than in either control group (Table 2).

Table 2. Incidence of Local Inflammatory Adverse Events with ZYNRELEF in Study 1 (Bunionectomy) Occurring with ≥2% Incidence and Higher than with Saline Placebo
 | Saline Placebo (N=101), % | Bupivacaine HCl 50 mg (N=154), % | ZYNRELEF 60 mg/1.8 mg (N=157), %
Incision site edema | 13 | 14 | 17
Incision site erythema | 8 | 12 | 13
Impaired healing | 1 | 4 | 6
Incision site cellulitis | 1 | 1 | 4
Wound dehiscence | 2 | 1 | 4
Incision site infection | 0 | 1 | 3

Table 3. Adverse Reactions with ZYNRELEF in Study 2 (Herniorrhaphy) Occurring with ≥5% Incidence and Higher than with Saline Placebo
Preferred Term | Saline Placebo (N=82), % | Bupivacaine HCl 75 mg (N=173), % | ZYNRELEF 300 mg/9 mg (N=163), %
Headache | 12 | 14 | 13
Bradycardia | 7 | 9 | 9
Dysgeusia | 4 | 12 | 9
Skin odor abnormal [All TEAEs of skin odor abnormal were recorded at a single site.] | 1 | 1 | 8

Table 4. Adverse Reactions with ZYNRELEF in Study 3 (Total Knee Arthroplasty) Occurring with ≥5% Incidence and Higher than with Saline Placebo
Preferred Term | Saline Placebo (N=53), % | Bupivacaine HCl 125 mg (N=55), % | ZYNRELEF 400 mg/12 mg (N=58), %
Nausea | 47 | 55 | 50
Constipation | 23 | 33 | 24
Vomiting | 19 | 27 | 26
Hypertension | 15 | 13 | 19
Pyrexia | 4 | 15 | 14
Leukocytosis | 0 | 2 | 7
Pruritis | 2 | 5 | 7
Headache | 0 | 7 | 7
Anemia | 2 | 0 | 5
Hyperhidrosis | 4 | 0 | 5
Hypotension | 4 | 2 | 5

6.2 Postmarketing Experience

The following adverse reactions have been identified during postapproval use of ZYNRELEF or other products containing NSAIDs. Because these reactions are reported voluntarily from a population of uncertain size, it is not always possible to reliably estimate their frequency or establish a causal relationship to drug exposure.

ZYNRELEF

Injury, Poisoning, and Procedural Complications: Wound necrosis, Wound dehiscence.

Surgical and Medical Procedures: Post-procedural drainage.

NSAIDs

Skin and Appendages: Exfoliative dermatitis, SJS, TEN, and FDE [see Warnings and Precautions (5.14)].

7 DRUG INTERACTIONS

7.1 Bupivacaine Drug Interactions

In clinical studies, other local anesthetics (including ropivacaine and lidocaine) have been administered before, during, or after application of ZYNRELEF without evidence of local anesthetic systemic toxicity. Administration of ZYNRELEF with other formulations of local anesthetics, including bupivacaine liposome injectable suspension, has not been studied [see Warnings and Precautions (5.3)].

The toxic effects of local anesthetics are additive. Avoid additional use of local anesthetics within 96 hours following administration of ZYNRELEF. If co-administration cannot be avoided, monitor patients for neurologic and cardiovascular effects related to local anesthetic systemic toxicity [see Dosage and Administration (2.1), Warnings and Precautions (5.1) and Overdosage (10)].

Patients who are administered local anesthetics may be at increased risk of developing methemoglobinemia when concurrently exposed to the following drugs, which could include other local anesthetics (Table 5).

Table 5. Examples of Drugs Associated with Methemoglobinemia
Class | Examples
Nitrates/Nitrites | nitric oxide, nitroglycerin, nitroprusside, nitrous oxide
Local anesthetics | articaine, benzocaine, bupivacaine, lidocaine, mepivacaine, prilocaine, procaine, ropivacaine, tetracaine
Antineoplastic agents | cyclophosphamide, flutamide, hydroxyurea, ifosfamide, rasburicase
Antibiotics | dapsone, nitrofurantoin, para-aminosalicylic acid, sulfonamides
Antimalarials | chloroquine, primaquine
Anticonvulsants | phenobarbital, phenytoin, sodium valproate
Other drugs | acetaminophen, metoclopramide, quinine, sulfasalazine

7.2 Meloxicam Drug Interactions

See Table 6 for clinically significant drug interactions with meloxicam.

Table 6. Clinically Significant Drug Interactions with Meloxicam
Drugs that Interfere with Hemostasis
Clinical Impact: | Meloxicam and anticoagulants such as warfarin have a synergistic effect on bleeding. The concomitant use of meloxicam and anticoagulants have an increased risk of serious bleeding compared to the use of either drug alone. Serotonin release by platelets plays an important role in hemostasis. Case-control and cohort epidemiological studies showed that concomitant use of drugs that interfere with serotonin reuptake and an NSAID may potentiate the risk of bleeding more than an NSAID alone.
Intervention: | Monitor patients with concomitant use of ZYNRELEF with anticoagulants (e.g., warfarin), antiplatelet agents (e.g., aspirin), selective serotonin reuptake inhibitors (SSRIs), and serotonin norepinephrine reuptake inhibitors (SNRIs) for signs of bleeding [see Warnings and Precautions (5.17)].
Aspirin
Clinical Impact: | In a clinical study, the concomitant use of an NSAID and aspirin was associated with a significantly increased incidence of GI adverse reactions as compared to use of the NSAID alone [see Warnings and Precautions (5.2)].
Intervention: | If aspirin is indicated in the postoperative period, monitor patients for signs and symptoms of GI bleeding [see Clinical Pharmacology (12.3)].
ACE Inhibitors, Angiotensin Receptor Blockers, or Beta-Blockers
Clinical Impact: | NSAIDs may diminish the antihypertensive effect of angiotensin converting enzyme (ACE) inhibitors, angiotensin receptor blockers (ARBs), or beta-blockers (including propranolol). In patients who are elderly, volume-depleted (including those on diuretic therapy), or have renal impairment, coadministration of an NSAID with ACE inhibitors or ARBs may result in deterioration of renal function, including possible acute renal failure. These effects are usually reversible.
Intervention: | During concomitant use of ZYNRELEF and ACE inhibitors, ARBs, or beta-blockers, monitor blood pressure to ensure that the desired blood pressure is obtained. During concomitant use of ZYNRELEF and ACE inhibitors or ARBs in patients who are elderly, volume-depleted, or have impaired renal function, monitor for signs of worsening renal function [see Warnings and Precautions (5.6)]. When these drugs are administered concomitantly, patients should be adequately hydrated. Assess renal function at the beginning of the concomitant treatment and periodically thereafter.
Diuretics
Clinical Impact: | Clinical studies, as well as post-marketing observations, showed that NSAIDs have reduced the natriuretic effect of loop diuretics (e.g., furosemide) and thiazide diuretics in some patients. This effect has been attributed to the NSAID inhibition of renal prostaglandin synthesis. However, studies with furosemide agents and meloxicam have not demonstrated a reduction in natriuretic effect. Furosemide single and multiple dose pharmacodynamics and pharmacokinetics are not affected by multiple doses of meloxicam.
Intervention: | During concomitant use of ZYNRELEF with diuretics, observe patients for signs of worsening renal function, in addition to assuring diuretic efficacy including antihypertensive effects.
Digoxin
Clinical Impact: | The concomitant use of NSAIDS with digoxin has been reported to increase the serum concentration and prolong the half-life of digoxin.
Intervention: | During concomitant use of ZYNRELEF and digoxin, monitor serum digoxin levels.
Lithium
Clinical Impact: | NSAIDs have produced elevations in plasma lithium levels and reductions in renal lithium clearance. The mean minimum lithium concentration increased 15%, and the renal clearance decreased by approximately 20%. This effect has been attributed to NSAID inhibition of renal prostaglandin synthesis [see Clinical Pharmacology (12.3)].
Intervention: | Monitor patients on lithium for signs of lithium toxicity.
Methotrexate
Clinical Impact: | Concomitant use of NSAIDs and methotrexate may increase the risk for methotrexate toxicity (e.g., neutropenia, thrombocytopenia, renal dysfunction).
Intervention: | During concomitant use of ZYNRELEF and methotrexate, monitor patients for methotrexate toxicity.
Cyclosporine
Clinical Impact: | Concomitant use of NSAIDs and cyclosporine may increase cyclosporine's nephrotoxicity.
Intervention: | During concomitant use of ZYNRELEF and cyclosporine, monitor patients for signs of worsening renal function.
NSAIDs and Salicylates
Clinical Impact: | Concomitant use of meloxicam with other NSAIDs or salicylates (e.g., diflunisal, salsalate) increases the risk of GI toxicity [see Warnings and Precautions (5.2)].
Intervention: | If additional NSAID or salicylate medication is indicated in the postoperative period, monitor patients for signs and symptoms of GI toxicity [see Clinical Pharmacology (12.3)].
Pemetrexed
Clinical Impact: | Concomitant use of NSAIDs and pemetrexed may increase the risk of pemetrexed-associated myelosuppression, renal, and GI toxicity (see the pemetrexed prescribing information).
Intervention: | During concomitant use of ZYNRELEF and pemetrexed, in patients with renal impairment whose creatinine clearance ranges from 45 to 79 mL/min, monitor for myelosuppression, renal and GI toxicity. Patients taking meloxicam should interrupt dosing for at least five days before, the day of, and two days following pemetrexed administration. In patients with creatinine clearance below 45 mL/min, the concomitant administration of meloxicam with pemetrexed is not recommended.

8 USE IN SPECIFIC POPULATIONS

8.1 Pregnancy

Risk Summary

There are no available human data on use of ZYNRELEF in pregnant women to evaluate for a drug-associated risk of major birth defects, miscarriage or adverse maternal or fetal outcomes. However, there are available data on the individual components of ZYNRELEF, bupivacaine and meloxicam.

Bupivacaine

The available data on bupivacaine use in pregnant women for epidural anesthesia (excluding paracervical block) are insufficient to draw conclusions about a drug-associated risk of major birth defects, miscarriage or adverse maternal or fetal outcomes. There are no adequate and well-controlled studies with bupivacaine in pregnant women. In animal studies, embryo-fetal lethality was noted when bupivacaine was administered subcutaneously to pregnant rabbits during organogenesis at a comparable bupivacaine dose level of 400 mg at the maximum recommended human dose (MRHD) of ZYNRELEF. Decreased pup survival was observed in a rat pre- and post-natal developmental study (dosing from implantation through weaning) at a comparable bupivacaine dose to the MRHD (see Data). Based on animal data, pregnant women should be advised of the potential risks to a fetus.

Meloxicam

Use of NSAIDs, including ZYNRELEF, can cause premature closure of the fetal ductus arteriosus and fetal renal dysfunction leading to oligohydramnios and, in some cases, neonatal renal impairment. Because of these risks, limit dose and duration of ZYNRELEF use between about 20 and 30 weeks of gestation and avoid ZYNRELEF use at about 30 weeks of gestation and later in pregnancy (see Clinical Considerations, Data).

Premature Closure of Fetal Ductus Arteriosus

Use of NSAIDs, including ZYNRELEF, at about 30 weeks gestation or later in pregnancy increases the risk of premature closure of the fetal ductus arteriosus.

Oligohydramnios/Neonatal Renal Impairment

Use of NSAIDs at about 20 weeks gestation or later in pregnancy has been associated with cases of fetal renal dysfunction leading to oligohydramnios, and in some cases, neonatal renal impairment.

Data from observational studies regarding other potential embryofetal risks of NSAID use in women in the first or second trimesters of pregnancy are inconclusive. In animal reproduction studies, embryofetal death was observed in rats and rabbits treated during the period of organogenesis with meloxicam at oral doses equivalent to 0.8 and 8 times, respectively, the meloxicam dose level of 12 mg at the MRHD of ZYNRELEF. Increased incidence of septal heart defects was observed in rabbits treated throughout embryogenesis with meloxicam at an oral dose equivalent to 97 times the MRHD. In pre- and post-natal reproduction studies, there was an increased incidence of dystocia, delayed parturition, and decreased offspring survival at 0.1 times the MRHD. No malformations were observed in rats and rabbits treated with meloxicam during organogenesis at an oral dose equivalent to 3.2 and 32 times, respectively, the MRHD (see Data).

Based on animal data, prostaglandins have been shown to have an important role in endometrial vascular permeability, blastocyst implantation, and decidualization. In animal studies, administration of prostaglandin synthesis inhibitors such as meloxicam, resulted in increased pre- and post-implantation loss. Prostaglandins also have been shown to have an important role in fetal kidney development. In published animal studies, prostaglandin synthesis inhibitors have been reported to impair kidney development when administered at clinically relevant doses.

The estimated background risk of major birth defects and miscarriage for the indicated population(s) is unknown. All pregnancies have a background risk of birth defect, loss, or other adverse outcomes. In the U.S. general population, the estimated background risk of major birth defects and miscarriage in clinically recognized pregnancies is 2% to 4% and 15% to 20%, respectively.

Clinical Considerations

Fetal/Neonatal Adverse Reactions

Meloxicam

Premature Closure of the Fetal Ductus Arteriosus:

Avoid use of NSAIDs in women at about 30 weeks gestation and later in pregnancy, because NSAIDs, including ZYNRELEF, can cause premature closure of the fetal ductus arteriosus (see Data).

Oligohydramnios/Neonatal Renal Impairment:

If an NSAID is necessary at about 20 weeks gestation or later in pregnancy, limit the use to the lowest effective dose and shortest duration possible. Because meloxicam can be detected in plasma beyond 48 hours after administration of ZYNRELEF, consider monitoring with ultrasound for oligohydramnios. If oligohydramnios occurs, follow up according to clinical practice (see Data).

Labor or Delivery

Bupivacaine

Bupivacaine is contraindicated in obstetrical paracervical block anesthesia. The use of bupivacaine for obstetrical paracervical block anesthesia has resulted in fetal bradycardia and death [see Contraindications (4)].

Bupivacaine can rapidly cross the placenta, and when used for epidural, caudal, or pudendal block anesthesia, can cause varying degrees of maternal, fetal, and neonatal toxicity [see Clinical Pharmacology (12.3)]. The incidence and degree of toxicity depend upon the procedure performed, the type and amount of drug used, and the technique of drug administration. Adverse reactions in the parturient, fetus, and neonate involve alterations of the central nervous system, peripheral vascular tone, and cardiac function.

Meloxicam

There are no studies on the effects of meloxicam during labor or delivery. In animal studies, NSAIDs, including meloxicam, inhibit prostaglandin synthesis, cause delayed parturition, and increase the incidence of stillbirth.

Data

Human Data

Meloxicam

Premature Closure of Fetal Ductus Arteriosus:

Published literature reports that the use of NSAIDs at about 30 weeks of gestation and later in pregnancy may cause premature closure of the fetal ductus arteriosus.

Oligohydramnios/Neonatal Renal Impairment:

Published studies and postmarketing reports describe maternal NSAID use at about 20 weeks gestation or later in pregnancy associated with fetal renal dysfunction leading to oligohydramnios, and in some cases, neonatal renal impairment. These adverse outcomes are seen, on average, after days to weeks of treatment, although oligohydramnios has been infrequently reported as soon as 48 hours after NSAID initiation. In many cases, but not all, the decrease in amniotic fluid was transient and reversible with cessation of the drug. There have been a limited number of case reports of maternal NSAID use and neonatal renal dysfunction without oligohydramnios, some of which were irreversible. Some cases of neonatal renal dysfunction required treatment with invasive procedures, such as exchange transfusion or dialysis.

Methodological limitations of these postmarketing studies and reports include lack of a control group; limited information regarding dose, duration, and timing of drug exposure; and concomitant use of other medications. These limitations preclude establishing a reliable estimate of the risk of adverse fetal and neonatal outcomes with maternal NSAID use. Because the published safety data on neonatal outcomes involved mostly preterm infants, the generalizability of certain reported risks to the full-term infant exposed to NSAIDs through maternal use is uncertain.

Animal Data

Reproduction studies have not been conducted with ZYNRELEF.

Bupivacaine

Bupivacaine HCl was administered subcutaneously to rats at doses of 4.4, 13.3, and 40 mg/kg and to rabbits at doses of 1.3, 5.8, and 22.2 mg/kg during the period of organogenesis (implantation to closure of the hard palate). The high doses are comparable to the daily MRHD of 400 mg on a mg/m^2 (BSA) basis. No embryo-fetal effects were observed in rats at the high dose which caused increased maternal lethality. An increase in embryo-fetal deaths was observed in rabbits at the high dose in the absence of maternal toxicity with the fetal No Observed Adverse Effect Level representing approximately 0.3 times the MRHD on a BSA basis.

In a rat pre- and post-natal developmental study (dosing from implantation through weaning) conducted at subcutaneous doses of 4.4, 13.3, and 40 mg/kg, decreased pup survival was observed at the high dose. The high dose is comparable to the daily MRHD of 400 mg on a BSA basis.

Meloxicam

Meloxicam did not cause malformations when administered to pregnant rats during fetal organogenesis at oral doses up to 4 mg/kg/day (3.2 times the meloxicam dose level of 12 mg at the MRHD of ZYNRELEF based on BSA comparison). Administration of meloxicam to pregnant rabbits throughout embryogenesis produced an increased incidence of septal defects of the heart at an oral dose of 60 mg/kg/day (97 times the MRHD based on BSA comparison). The no effect level was 20 mg/kg/day (32 times the MRHD based on BSA comparison). In rats and rabbits, embryolethality occurred at oral meloxicam doses of 1 mg/kg/day and 5 mg/kg/day, respectively (0.8 and 8 times the MRHD, respectively, based on BSA comparison) when administered throughout organogenesis.

Oral administration of meloxicam to pregnant rats during late gestation through lactation increased the incidence of dystocia, delayed parturition, and decreased offspring survival at meloxicam doses of 0.125 mg/kg/day or greater (0.1 times the MRHD based on BSA comparison).

8.2 Lactation

Risk Summary

Limited published literature reports that bupivacaine and its primary metabolite, pipecoloxylidine (PPX), are present in human milk at low levels. There are no human data available on whether meloxicam is present in human milk. There is no available information on effects of bupivacaine or meloxicam in the breastfed infant or effects of the drugs on milk production.

The developmental and health benefits of breastfeeding should be considered along with the mother's clinical need for ZYNRELEF and any potential adverse effects on the breastfed infant from ZYNRELEF or from the underlying maternal condition.

Data

Animal Data

Following administration of ZYNRELEF to lactating pigs, bupivacaine and meloxicam were detected in milk, but only bupivacaine was detected in the plasma of piglets allowed to suckle milk from the treated animals. Meloxicam was present in the milk of lactating rats at concentrations higher than those in plasma.

8.3 Females and Males of Reproductive Potential

Infertility

Females

Based on the mechanism of action, the use of prostaglandin-mediated NSAIDs, including meloxicam, may delay or prevent rupture of ovarian follicles, which has been associated with reversible infertility in some women. Published animal studies have shown that administration of prostaglandin synthesis inhibitors has the potential to disrupt prostaglandin-mediated follicular rupture required for ovulation. Small studies in women treated with NSAIDs have also shown a reversible delay in ovulation. Consider withdrawal of NSAIDs and avoidance of ZYNRELEF in women who have difficulties conceiving or who are undergoing investigation of infertility.

Males

In a published study, oral administration of meloxicam to male rats for 35 days resulted in decreased sperm count and motility and histopathological evidence of testicular degeneration at 0.8 times the MRHD based on BSA comparison [see Nonclinical Toxicology (13.1)]. It is not known if these effects on fertility are reversible. The clinical relevance of these findings is unknown.

8.4 Pediatric Use

Safety and effectiveness of ZYNRELEF in pediatric patients has not been established.

8.5 Geriatric Use

Of the total number of patients undergoing various surgical procedures who were exposed to ZYNRELEF in clinical studies (N=1627), 288 patients (17.7%) were ≥ 65 years old, while 83 (5.1%) were ≥75 years old. No overall differences in safety or efficacy were observed between elderly patients and younger patients, but greater sensitivity of some older individuals cannot be ruled out.

Elderly patients, compared to younger patients, are at greater risk for NSAID-associated serious cardiovascular, gastrointestinal, and/or renal adverse reactions, although the applicability of this to a single administration of low-dose meloxicam in ZYNRELEF is uncertain [see Warnings and Precautions (5.1, 5.2, 5.8)].

In clinical studies, differences in various pharmacokinetic parameters have been observed with bupivacaine HCl between elderly and younger patients. Bupivacaine is known to be substantially excreted by the kidney, and the risk of toxic reactions to bupivacaine may be greater in patients with impaired renal function. Because elderly patients are more likely to have decreased renal function, care should be taken in ZYNRELEF dose selection, and it may be useful to monitor renal function [see Clinical Pharmacology (12.3)]. Consider reducing the dose of ZYNRELEF for elderly patients.

8.6 Hepatic Impairment

Amide-type local anesthetics such as bupivacaine are metabolized primarily in the liver. Patients with severe hepatic disease, because of their inability to metabolize local anesthetics normally, are at a greater risk of developing toxic plasma concentrations, and potentially local anesthetic systemic toxicity.

Because meloxicam is primarily metabolized in the liver and hepatotoxicity may occur, monitor patients with hepatic impairment for signs and symptoms of worsening disease. Meloxicam has not been adequately studied in patients with severe hepatic impairment.

No dose adjustment of ZYNRELEF is necessary in patients with mild to moderate hepatic impairment. ZYNRELEF should only be used in patients with severe hepatic impairment if the benefits are expected to outweigh the risks; monitor patients for signs of worsening liver function. Consider increased monitoring for local anesthetic systemic toxicity in subjects with moderate to severe hepatic disease [see Warnings and Precautions (5.5), and Clinical Pharmacology (12.3)].

8.7 Renal Impairment

Because bupivacaine and meloxicam and their metabolites are excreted by the kidney, the risk of toxic reactions to these drugs may be greater in patients with impaired renal function. This should be considered when performing dose selection of ZYNRELEF. Consider reducing the dose of ZYNRELEF for patients with mild to moderate renal impairment.

Patients with severe renal disease, may be more susceptible to the potential toxicities of the amide-type local anesthetics. Patients with severe renal impairment have not been studied. The use of ZYNRELEF in patients with severe renal impairment is not recommended. Meloxicam is not dialyzable. When using ZYNRELEF in patients on hemodialysis do not exceed maximum recommended dose or use with other meloxicam-containing products [see Clinical Pharmacology (12.3)].

8.8 Poor Metabolizers of CYP2C9 Substrates

In patients who are known or suspected to be poor CYP2C9 metabolizers based on genotype or previous history/experience with other CYP2C9 substrates (such as warfarin or phenytoin), consider dose reduction, as these patients may have abnormally high plasma levels of meloxicam due to reduced metabolic clearance. Monitor these patients for adverse effects.

10 OVERDOSAGE

No data are available with regard to overdose of ZYNRELEF. Findings related to the individual active substances are listed below.

10.1 Bupivacaine

Clinical Presentation

Acute emergencies from local anesthetics are generally related to high plasma concentrations encountered during therapeutic use of local anesthetics or to unintended intravascular injection of local anesthetic solution [see (Warnings and Precautions (5.3) and Adverse Reactions (6)].

Following administration of ZYNRELEF (400 mg/12 mg) by instillation, a highest individual maximum plasma concentration (Cmax) of bupivacaine of 1830 ng/mL was reported. No apparent bupivacaine-related systemic toxicity was observed.

Signs and symptoms of overdose include CNS symptoms (dizziness, sensory and visual disturbances, and eventually convulsions) and cardiovascular effects (that range from hypertension and tachycardia to myocardial depression, hypotension, bradycardia, and asystole).

Plasma levels of bupivacaine associated with toxicity can vary. Although concentrations of 2,000 to 4,000 ng/mL have been reported to elicit early subjective CNS symptoms of bupivacaine toxicity, symptoms of toxicity have been reported at levels as low as 800 ng/mL.

Management of Local Anesthetic Overdose

At the first sign of change, oxygen should be administered.

The first step in the management of convulsions, as well as underventilation or apnea, consists of immediate attention to the maintenance of a patent airway and assisted or controlled ventilation with oxygen and a delivery system capable of permitting immediate positive airway pressure by mask. Immediately after the institution of these ventilatory measures, the adequacy of the circulation should be evaluated, keeping in mind that drugs used to treat convulsions sometimes depress the circulation when administered intravenously. Should convulsions persist despite adequate respiratory support, and if the status of the circulation permits, small increments of an ultra-short acting barbiturate (such as thiopental or thiamylal) or a benzodiazepine (such as diazepam) may be administered intravenously. The clinician should be familiar, prior to the use of anesthetics, with these anticonvulsant drugs. Supportive treatment of circulatory depression may require administration of intravenous fluids and, when appropriate, a vasopressor dictated by the clinical situation (such as ephedrine to enhance myocardial contractile force).

If not treated immediately, both convulsions and cardiovascular depression can result in hypoxia, acidosis, bradycardia, arrhythmias, and cardiac arrest. If cardiac arrest should occur, standard cardiopulmonary resuscitative measures should be instituted.

Endotracheal intubation, employing drugs, and techniques familiar to the clinician, may be indicated after initial administration of oxygen by mask if difficulty is encountered in the maintenance of a patent airway or if prolonged ventilatory support (assisted or controlled) is indicated.

10.2 Meloxicam

Symptoms following acute NSAID overdosages have been typically limited to lethargy, drowsiness, nausea, vomiting, and epigastric pain, which have been generally reversible with supportive care. Gastrointestinal bleeding has occurred. Hypertension, acute renal failure, respiratory depression, and coma have occurred, but were rare [see Warnings and Precautions (5.2, 5.6, 5.8)]. There is limited experience with meloxicam overdosage. Manage patients with symptomatic and supportive care following an NSAID overdosage. There are no specific antidotes. Forced diuresis, alkalinization of urine, hemodialysis, or hemoperfusion may not be useful due to high protein binding.

For additional information about overdosage treatment, call a poison control center (1-800-222-1222).

11 DESCRIPTION

ZYNRELEF (bupivacaine and meloxicam) extended-release solution, for soft tissue or periarticular instillation use, contains bupivacaine, an amide local anesthetic, and meloxicam, a nonsteroidal anti-inflammatory drug (NSAID).

Bupivacaine

Bupivacaine is a white to off-white crystalline powder, crystals, or granules. The chemical name for bupivacaine is (±)-1-butyl-N-(2,6-dimethylphenyl)piperidine-2-carboxamide, and its empirical formula is C18H28N2O. The molecular weight of bupivacaine is 288.4. Bupivacaine is sparingly soluble in water and freely soluble in alcohol. Bupivacaine has a log Pow of 1.82 and a pKa of 8.1. Bupivacaine has the following structural formula:

Meloxicam

Meloxicam is a pale yellow solid, practically insoluble in water, with higher solubility observed in strong acids and bases. It is very slightly soluble in methanol. Meloxicam has an apparent partition coefficient (log P)app = 0.1 in n-octanol/buffer pH 7.4. Meloxicam has pKa values of 1.1 and 4.2. Meloxicam is chemically designated as 4-hydroxy-2-methyl-N-(5-methyl-2-thiazolyl)-2H-1,2-benzothiazine-3-carboxamide-1,1-dioxide. The molecular weight is 351.4. Its empirical formula is C14H13N3O4S2 and it has the following structural formula:

ZYNRELEF is a sterile, clear, pale yellow to yellow, viscous liquid provided in single-dose vials (10 mL or 20 mL) for instillation into the surgical site. Each mL of the solution contains active ingredients bupivacaine 29.25 mg and meloxicam 0.88 mg; and inactive ingredients tri(ethylene glycol) poly(orthoester) (730 mg), triacetin (293 mg), dimethyl sulfoxide (117 mg), and maleic acid (0.59 mg).

12 CLINICAL PHARMACOLOGY

12.1 Mechanism of Action

ZYNRELEF is a fixed-dose combination of bupivacaine and meloxicam.

Bupivacaine

Local anesthetics block the generation and the conduction of nerve impulses presumably by increasing the threshold for electrical excitation in the nerve, by slowing the propagation of the nerve impulse, and by reducing the rate of rise of the action potential. In general, the progression of anesthesia is related to the diameter, myelination, and conduction velocity of affected nerve fibers. Clinically, the order of loss of nerve function is as follows: (1) pain, (2) temperature, (3) touch, (4) proprioception, and (5) skeletal muscle tone.

Meloxicam

The mechanism of action of meloxicam, like that of other NSAIDs, is not completely understood but involves inhibition of cyclooxygenase (COX-1 and COX-2).

Meloxicam is a potent inhibitor of prostaglandin synthesis in vitro. Prostaglandins sensitize afferent nerves and potentiate the action of bradykinin in inducing pain in animal models. Prostaglandins are mediators of inflammation. Because meloxicam is an inhibitor of prostaglandin synthesis, its mode of action may be due to a decrease of prostaglandins in peripheral tissues.

12.2 Pharmacodynamics

Additional pharmacodynamic data in clinical studies

Additional pharmacodynamic data for ZYNRELEF was evaluated in patients undergoing abdominoplasty, Cesarean section, total shoulder arthroplasty, and 1- to 3-level lumbar spinal surgery. Refer to Dosage and Administration for specific doses used for each study [see Dosage and Administration (2.4)].

Contribution of Meloxicam and Bupivacaine to Activity of ZYNRELEF

The contribution of each active ingredient in ZYNRELEF was demonstrated in Phase 2 double-blind, randomized, active- and placebo-controlled clinical studies in subjects undergoing herniorrhaphy or bunionectomy, utilizing ZYNRELEF and formulations of meloxicam alone or bupivacaine alone in the ZYNRELEF vehicle. In both studies, meloxicam alone demonstrated negligible local analgesia and bupivacaine alone demonstrated greater analgesia compared with placebo through 24 hours post surgery, despite exposure to bupivacaine for approximately 72 hours. Compared with bupivacaine alone in both studies, ZYNRELEF (at the same bupivacaine doses) demonstrated greater and longer analgesia through 24, 48, and 72 hours.

Effect on Cardiac Repolarization

The effect of ZYNRELEF on cardiac repolarization as assessed by the QTc interval was evaluated following a single administration in patients undergoing surgical procedures. ZYNRELEF, at single doses up to the maximum recommended dose, did not demonstrate an effect on the QTc interval.

Bupivacaine

Systemic absorption of local anesthetics, including bupivacaine, produces effects on the cardiovascular and central nervous systems (CNS), which can be serious at toxic blood concentrations [see Warnings and Precautions (5.3)]. At blood concentrations achieved with normal therapeutic doses, manifestations of CNS stimulation and depression or changes in cardiac conduction, excitability, refractoriness, contractility, and peripheral vascular resistance are minimal. Clinical reports and animal research suggest that cardiovascular changes are more likely to occur after unintended intravascular injection of bupivacaine.

12.3 Pharmacokinetics

The instillation of ZYNRELEF into the surgical site results in systemic plasma levels of bupivacaine and meloxicam for up to the duration as described in Table 7 for soft tissue surgical procedures and Table 8 for orthopedic surgical procedures. Systemic plasma levels of bupivacaine or meloxicam following application of ZYNRELEF do not correlate with local efficacy.

Absorption

The rate of systemic absorption of bupivacaine or meloxicam from ZYNRELEF is dependent upon the total dose of drug administered and the vascularity of the administration site.

Pharmacokinetic parameters of bupivacaine and meloxicam after single dose administration by instillation of ZYNRELEF were evaluated following multiple surgical procedures.

Descriptive statistics of pharmacokinetic parameters of representative ZYNRELEF doses are provided in Table 7 for soft tissue surgical procedures and Table 8 for orthopedic surgical procedures.

Table 7. Summary of Pharmacokinetic Parameters for Bupivacaine and Meloxicam After Single Dose Administration of ZYNRELEF by Instillation for Soft Tissue Surgical Procedures
Active Ingredient | Parameter | Herniorrhaphy: 300 mg/9 mg ZYNRELEF (N=16) | Abdominoplasty: 400 mg/12 mg ZYNRELEF (N=22) | Augmentation Mammoplasty: 400 mg/12 mg ZYNRELEF (N=49) | Cesarean Section: 400 mg/12 mg ZYNRELEF (N=11)
Bupivacaine | Cmax (ng/mL) | 271 (147) | 382 (149) | 710 (246) | 291 (70)
Bupivacaine | Tmax (h) | 18 (3, 30) | 31 (20, 54) | 3.6 (1.3, 35) | 24 (1.1, 48)
Bupivacaine | AUC(0-t) [AUC(0-t): 0 to 120 h post-dose for herniorrhaphy, augmentation mammoplasty, and Cesarean section; 0 to 144 h post-dose for abdominoplasty.] (h×ng/mL) | 15174 (8545) | 24411 (10072) | 27363 (9227) | 17923 (5069)
Bupivacaine | AUC(inf) (h×ng/mL) | 15524 (8921) | 24930 (10105) | 31072 (17998) | 17983 (5065)
Bupivacaine | t½ (h) | 16 (9) | 20 (8) | 25 (20) | 10 (2)
Bupivacaine | C72h (ng/mL) | 96 (75) | 202 (118) | 149 (68) [N=48;] | 127 (56)
Bupivacaine | C96h (ng/mL) | 37 (43) | 86 (52) [N=21;] | NS | 27 (16)
Bupivacaine | C144h (ng/mL) | NS | 16 (11) | NS | 0.8 (1.0) [N=10]
Meloxicam | Cmax (ng/mL) | 225 (96) | 116 (62) | 527 (149) | 114 (49)
Meloxicam | Tmax (h) | 54 (24, 96) | 24 (4.0, 72) | 20 (5.6, 49) | 60 (8.5, 73)
Meloxicam | AUC(0-t) (h×ng/mL) | 18721 (7923) | 7924 (4197) | 30499 (9460) | 9710 (4560)
Meloxicam | AUC(inf) (h×ng/mL) | NR | 8304 (4422) | 41809 (38414) | 9778 (4592)
Meloxicam | t½ (h) | NR | 21 (9) | 42 (70) | 21 (9)
Meloxicam | C72h (ng/mL) | 197 (95) | 70 (44) | 214 (105) | 86 (43)
Meloxicam | C96h (ng/mL) | 146 (86) | 33 (25) | NS | 48 (32)
Meloxicam | C144h (ng/mL) | NS | 7.1 (10) | NS | 11 (12)
Note: Arithmetic mean (standard deviation) except Tmax where it is median (min, max). Doses of ZYNRELEF are shown as bupivacaine dose (mg)/meloxicam dose (mg).
NS = not sampled; NR= not reported, since the terminal elimination phase was not adequately characterized in sufficient number of patients.

Table 8. Summary of Pharmacokinetic Parameters for Bupivacaine and Meloxicam After Single Dose Administration of ZYNRELEF by Instillation for Orthopedic Surgical Procedures
Active Ingredient | Parameter | Bunionectomy: 60 mg/1.8 mg ZYNRELEF (N=17) | Total Knee Arthroplasty: 400 mg/12 mg ZYNRELEF (N=53) | Total Shoulder Arthroplasty: 400 mg/12 mg ZYNRELEF (N=20) | 1-Level Spinal Surgery: 92 mg/2.8 mg ZYNRELEF (N=13) | 2- or 3-Level Spinal Surgery: 191 mg/5.7 mg ZYNRELEF (N=13)
Bupivacaine | Cmax (ng/mL) | 54 (33) | 695 (411) | 372 (165) | 95 (105) | 163 (67)
Bupivacaine | Tmax (h) | 3.0 (1.6, 24) | 21 (4, 59) | 20 (1.8, 48) | 23 (1.9, 38) | 24 (4.1, 69)
Bupivacaine | AUC(0-t) [AUC(0-t): 0 to 120 h post-dose for bunionectomy and lumbar spinal decompression; 0 to 144 h post-dose for total knee arthroplasty and total shoulder arthroplasty.] (h×ng/mL) | 1681 (1154) | 35889 (28399) | 21132 (12331) | 4467 (4977) | 8488 (4086)
Bupivacaine | AUC(inf) (h×ng/mL) | 1718 (1211) | 38173 (29401) [N=50;] | 21193 (12329) | 5535 (6091) [N=12;] | 8659 (4288) [N=11;]
Bupivacaine | t½ (h) | 15 (8) | 17 (7) | 10 (3) | 25 (25) | 14 (5)
Bupivacaine | C72h (ng/mL) | 5.0 (5.3) | 227 (283) | 145 (117) | 34 (48) | 61 (49)
Bupivacaine | C96h (ng/mL) | 1.7 (2.9) [N=16;] | NS | 30 (32) | 5.2 (7.3) | 24 (27)
Bupivacaine | C144h (ng/mL) | NS | 5.3 (21) [N=32;] | 1.1 (2.2) [N=19;] | NS | NS
Meloxicam | Cmax (ng/mL) | 26 (14) | 275 (134) | 248 (125) [N=18;] | 53 (41) [N=13;] | 90 (36)
Meloxicam | Tmax (h) | 18 (8, 60) | 36 (12, 72) | 57 (12, 72) | 18 (12, 72) | 43 (23, 69)
Meloxicam | AUC(0-t) (h×ng/mL) | 1621 (927) | 19525 (12259) | 22292 (12250) | 3556 (2665) | 6269 (3133)
Meloxicam | AUC(inf) (h×ng/mL) | 2079 (1631) | 25673 (17666) [N=35;] | 24133 (15285) [N=17;] | 3826 (3890) | 8265 (5874) [N=10;]
Meloxicam | t½ (h) | 33 (36) | 42 (37) | 29 (11) | 35 (15) | 38 (22)
Meloxicam | C72h (ng/mL) | 13 (9) | 202 (120) | 228 (131) | 44 (44) | 69 (37)
Meloxicam | C96h (ng/mL) | 7.7 (5.8) [N=15;] | NS | 158 (126) | 21 (23) | 43 (28)
Meloxicam | C144h (ng/mL) | NS | 28 (37) [N=28] | 52 (56) | NS | NS
Note: Arithmetic mean (standard deviation) except Tmax where it is median (min, max). Doses of ZYNRELEF are shown as bupivacaine dose (mg)/meloxicam dose (mg). For spinal surgery, ZYNRELEF mean doses for single-level and multilevel surgeries are shown; individual doses ranged from 45 mg/1.4 mg to 248 mg/7.4 mg.
NS = not sampled.

Distribution

After bupivacaine and meloxicam have been released from ZYNRELEF and are absorbed systemically, their distribution is expected to be the same as for other bupivacaine HCl solution formulations or meloxicam oral formulation.

Bupivacaine

Local anesthetics including bupivacaine are distributed to some extent to all body tissues, with high concentrations found in highly perfused organs such as the liver, lungs, heart, and brain. Local anesthetics are bound to plasma proteins in varying degrees. Generally, the lower the plasma concentration of drug, the higher the percentage of drug bound to plasma proteins.

Local anesthetics including bupivacaine appear to cross the placenta by passive diffusion. The rate and degree of diffusion is governed by (1) the degree of plasma protein binding, (2) the degree of ionization, and (3) the degree of lipid solubility. Fetal/maternal ratios of local anesthetics appear to be inversely related to the degree of plasma protein binding, because only the free, unbound drug is available for placental transfer. Bupivacaine with a high protein binding capacity (95%) has a low fetal/maternal ratio (0.2 to 0.4). The extent of placental transfer is also determined by the degree of ionization and lipid solubility of the drug. Lipid soluble, non-ionized drugs, such as bupivacaine, readily enter the fetal blood from the maternal circulation.

Meloxicam

Meloxicam is ~99.4% bound to human plasma proteins (primarily albumin) within the therapeutic dose range of oral meloxicam. The fraction of protein binding is independent of drug concentration, over the clinically relevant concentration range, but decreases to ~99% in patients with renal disease. Meloxicam penetration into human red blood cells, after oral dosing, is less than 10%. Following a radiolabeled dose, over 90% of the radioactivity detected in the plasma was present as unchanged meloxicam. Meloxicam concentrations in synovial fluid, after a single oral dose, range from 40% to 50% of those in plasma. The free fraction in synovial fluid is 2.5 times higher than in plasma, due to the lower albumin content in synovial fluid as compared to plasma. The significance of this penetration is unknown.

Elimination

Metabolism

Bupivacaine

Amide-type local anesthetics such as bupivacaine are metabolized primarily in the liver via conjugation with glucuronic acid. Pipecoloxylidine is the major metabolite of bupivacaine. The elimination of drug from tissue distribution depends largely upon the ability of plasma protein binding sites in the circulation to carry it to the liver where it is metabolized [see Use in Specific Populations (8.6)].

Meloxicam

Meloxicam is extensively metabolized in the liver. Meloxicam metabolites include 5'-carboxy meloxicam (60% of dose), from P450 mediated metabolism formed by oxidation of an intermediate metabolite 5'‑hydroxymethyl meloxicam which is also excreted to a lesser extent (9% of dose). In vitro studies indicate that CYP2C9 (cytochrome P450 metabolizing enzyme) plays an important role in this metabolic pathway with a minor contribution of the CYP3A4 isozyme. Patients' peroxidase activity is probably responsible for the other two metabolites which account for 16% and 4% of the administered dose, respectively. The four metabolites are not known to have any in vivo pharmacological activity.

Excretion

After bupivacaine and meloxicam have been released from ZYNRELEF and are absorbed systemically, their excretion is expected to be the same as for other bupivacaine HCl solution formulations or meloxicam oral formulations.

Bupivacaine

The kidney is the main excretory organ for most local anesthetics and their metabolites. Urinary excretion is affected by urinary perfusion and factors affecting urinary pH. Only 6% of bupivacaine is excreted unchanged in the urine.

When administered in recommended doses and concentrations, bupivacaine HCl does not ordinarily produce irritation or tissue damage. The mean apparent terminal half-life (t1/2) for bupivacaine from ZYNRELEF is approximately 10 to 25 hours.

Meloxicam

Meloxicam excretion is predominately in the form of metabolites, and occurs to equal extents in the urine and feces. Following oral meloxicam, only traces of the unchanged parent compound are excreted in the urine (0.2%) and feces (1.6%). The extent of the urinary excretion was confirmed for unlabeled multiple 7.5 mg oral meloxicam doses: 0.5%, 6%, and 13% of the dose were found in urine in the form of meloxicam, and the 5'-hydroxymethyl and 5'-carboxy metabolites, respectively. There is significant biliary and/or enteral secretion of the drug. This was demonstrated when oral administration of cholestyramine following a single IV dose of meloxicam decreased the AUC of meloxicam by 50%.

The mean apparent terminal half-life (t1/2) for meloxicam from ZYNRELEF is approximately 21 to 42 hours.

Specific Populations

Effect of Age, Sex, Race, and Ethnicity on Pharmacokinetics

Based on the population pharmacokinetic analysis, age, sex, race, and ethnicity do not have a clinically meaningful effect on the pharmacokinetics of bupivacaine and meloxicam in ZYNRELEF [see Use in Special Populations (8.5)].

Hepatic Impairment

After bupivacaine and meloxicam have been released from ZYNRELEF and are absorbed systemically, the effects of hepatic impairment are expected to be the same as for other bupivacaine and meloxicam formulations [see Warnings and Precautions (5.5)].

Bupivacaine

Various pharmacokinetic parameters of the local anesthetics can be significantly altered by the presence of hepatic disease. Patients with hepatic disease, especially those with severe hepatic disease, may be more susceptible to the potential toxicities of the amide-type local anesthetics [see Use in Specific Populations (8.6)].

Meloxicam

Following a single 15 mg dose of oral meloxicam there was no marked difference in plasma concentrations in patients with mild (Child-Pugh Class I) or moderate (Child-Pugh Class II) hepatic impairment compared to healthy volunteers. Protein binding of oral meloxicam was not affected by hepatic impairment. No dosage adjustment of ZYNRELEF is necessary in patients with mild to moderate hepatic impairment. Patients with severe hepatic impairment (Child-Pugh Class III) have not been adequately studied [see Use in Specific Populations (8.6)].

Renal Impairment

After bupivacaine and meloxicam have been released from ZYNRELEF and are absorbed systemically, the effects of renal impairment are expected to be the same as for other bupivacaine and meloxicam formulations.

Bupivacaine

Various pharmacokinetic parameters of the local anesthetics can be significantly altered by the presence of renal disease, factors affecting urinary pH, and renal blood flow [see Warnings and Precautions (5.8) and Use in Specific Populations (8.7)].

Meloxicam

Meloxicam pharmacokinetics with oral meloxicam have been investigated in patients with mild and moderate renal impairment. Following oral meloxicam, total drug plasma concentrations of meloxicam decreased and total clearance of meloxicam increased with the degree of renal impairment while free AUC values were similar in all groups. The higher meloxicam clearance in patients with renal impairment may be due to increased fraction of unbound meloxicam which is available for hepatic metabolism and subsequent excretion. No dosage adjustment of ZYNRELEF is necessary in patients with mild to moderate renal impairment. Patients with severe renal impairment have not been adequately studied. The use of ZYNRELEF in patients with severe renal impairment is not recommended [see Warnings and Precautions (5.8) and Use in Specific Populations (8.7)].

Hemodialysis: Following a single oral dose of meloxicam, the free Cmax plasma concentrations were higher in patients with renal failure on chronic hemodialysis (1% free fraction) in comparison to healthy volunteers (0.3% free fraction). Hemodialysis did not lower the total drug concentration in plasma. Meloxicam is not dialyzable [see Use in Specific Populations (8.7)].

Drug Interaction Studies

Aspirin: When NSAIDs were administered with aspirin, the protein binding of NSAIDs were reduced, although the clearance of free NSAID was not altered. The clinical significance of this interaction is not known. See Table 6 for clinically significant drug interactions of NSAIDs with aspirin [see Drug Interactions (7)].

Cholestyramine: Pretreatment for four days with cholestyramine significantly increased the clearance of oral meloxicam by 50%. This resulted in a decrease in t1/2, from 19.2 hours to 12.5 hours, and a 35% reduction in AUC. This suggests the existence of a recirculation pathway for oral meloxicam in the gastrointestinal tract. The clinical relevance of this interaction has not been established.

Cimetidine: Concomitant administration of 200 mg cimetidine four times daily did not alter the single-dose pharmacokinetics of 30 mg oral meloxicam.

Digoxin: Oral meloxicam 15 mg once daily for 7 days did not alter the plasma concentration profile of digoxin after β-acetyldigoxin administration for 7 days at clinical doses. In vitro testing found no protein binding drug interaction between digoxin and meloxicam.

Lithium: In a study conducted in healthy patients, mean pre-dose lithium concentration and AUC were increased by 21% in patients receiving lithium doses ranging from 804 to 1072 mg twice daily with oral meloxicam 15 mg QD every day as compared to patients receiving lithium alone [see Drug Interactions (7)].

Methotrexate: A study in 13 rheumatoid arthritis (RA) patients evaluated the effects of multiple doses of meloxicam on the pharmacokinetics of methotrexate taken once weekly. Meloxicam did not have a significant effect on the pharmacokinetics of single doses of methotrexate. In vitro, methotrexate did not displace meloxicam from its human serum binding sites.

Warfarin: The effect of oral meloxicam on the anticoagulant effect of warfarin was studied in a group of healthy patients receiving daily doses of warfarin that produced an INR (International Normalized Ratio) between 1.2 and 1.8. In these patients, oral meloxicam did not alter warfarin pharmacokinetics and the average anticoagulant effect of warfarin as determined by prothrombin time. However, one patient showed an increase in INR from 1.5 to 2.1. Caution should be used when administering oral meloxicam with warfarin since patients on warfarin may experience changes in INR and an increased risk of bleeding complications when a new medication is introduced.

12.5 Pharmacogenomics

CYP2C9 activity is reduced in individuals with genetic variants such as CYP2C9*2 and CYP2C9*3 polymorphisms. Limited data from three published reports showed that meloxicam AUC was substantially higher in individuals with reduced CYP2C9 activity, particularly in poor metabolizers (e.g., *3/*3), compared to normal metabolizers (*1/*1). The frequency of CYP2C9 poor metabolizer genotypes varies based on racial/ethnic background but is generally present in <5% of the population.

13 NONCLINICAL TOXICOLOGY

13.1 Carcinogenesis, Mutagenesis, and Impairment of Fertility

The maximum recommended human dose (MRHD) of ZYNRELEF is 400 mg and 12 mg of bupivacaine and meloxicam, respectively.

Carcinogenesis

Bupivacaine

Long-term studies in animals to evaluate the carcinogenic potential of ZYNRELEF or bupivacaine have not been conducted.

Meloxicam

There was no increase in tumor incidence in long-term carcinogenicity studies in rats (104 weeks) or mice (99 weeks) administered meloxicam at oral doses up to 0.8 mg/kg/day in rats and up to 8.0 mg/kg/day in mice (up to 0.6 and 3.2 times, respectively, the meloxicam dose level of 12 mg at the MRHD of ZYNRELEF based on BSA comparison).

Mutagenesis

Bupivacaine

The mutagenic potential of bupivacaine has not been determined.

Meloxicam

Meloxicam was not mutagenic in an Ames assay, or clastogenic in a chromosome aberration assay with human lymphocytes and an in vivo micronucleus test in mouse bone marrow.

Impairment of Fertility

Bupivacaine

The effect of ZYNRELEF and bupivacaine on fertility has not been determined.

Meloxicam

Meloxicam did not impair male and female fertility in rats at oral doses up to 9 mg/kg/day in males and 5 mg/kg/day in females (up to 7.3 and 4 times, respectively, the MRHD based on BSA comparison).

In a published study, oral administration of 1 mg/kg (0.8 times the MRHD) meloxicam to male rats for 35 days resulted in decreased sperm count and motility and histopathological evidence of testicular degeneration. The clinical relevance of these findings is unknown.

13.2 Animal Toxicology and/or Pharmacology

Necrosis and degeneration of cartilage and chondrocytes were observed following intra-articular injection of a single dose of ZYNRELEF in the knee joint of rabbits. Cartilage degeneration was also observed following intra-articular injection of a single dose of ZYNRELEF in the knee joints of dogs.

14 CLINICAL STUDIES

The efficacy of ZYNRELEF was established in 3 double-blind, controlled studies in patients undergoing bunionectomy (Study 1), unilateral open inguinal herniorrhaphy (Study 2), and total knee arthroplasty (Study 3). Refer to 12.2 for additional supportive pharmacodynamic data for ZYNRELEF [see Pharmacodynamics (12.2)].

Based on the extrapolation of efficacy of ZYNRELEF across the 3 double-blind, controlled studies in patients undergoing bunionectomy, unilateral open inguinal herniorrhaphy, and total knee arthroplasty, and the pharmacokinetic profiles across surgical procedures with varied characteristics, such as anatomic location, tissue type, length and depth of surgical area, and vascularity, the pharmacokinetic profile and effectiveness of ZYNRELEF are not expected to be clinically significantly different when ZYNRELEF is administered at an appropriate dose in other soft tissue and orthopedic surgical procedures [see Dosage and Administration (2.4), Adverse Reactions (6.1) and Clinical Pharmacology (12.3)].

Study 1

In this multicenter, double-blind, parallel-group, active- and placebo-controlled clinical trial (NCT03295721), 412 patients undergoing unilateral simple bunionectomy with a lidocaine Mayo block were randomized to 1 of the following 3 treatment groups in a 3:3:2 ratio (respectively): ZYNRELEF 60 mg/1.8 mg, bupivacaine HCl 50 mg, or saline placebo. The mean patient age was 47 years (range 18 to 77) and patients were predominantly female (86%). ZYNRELEF was applied directly into the surgical site, using the cone-shaped applicator, at the end of the procedure, after final irrigation and suction but prior to closure. Bupivacaine HCl and saline placebo were administered by injection and instillation, respectively. Pain intensity was rated by patients using an 11-point numeric rating scale (NRS) out to 72 hours post-dose. Postoperatively, there was no scheduled pain medication regimen; however, patients were allowed rescue medication as needed, and included oxycodone 10 mg orally every 4 hours, morphine 10 mg IV every 2 hours, and/or acetaminophen 1000 mg orally every 6 hours. The primary endpoint was the mean area under the curve (AUC) of the NRS pain intensity scores (cumulative pain scores) with activity over the 72-hour period for the ZYNRELEF treatment group compared to the saline placebo treatment group. Secondary endpoints included mean AUC of NRS pain intensity scores over the 72-hour period for the ZYNRELEF treatment group compared to the bupivacaine HCl treatment group, proportion of patients who did not receive opioid analgesia, and total opioid consumption.

Patients treated with ZYNRELEF demonstrated a significant reduction in pain intensity compared to those treated with either bupivacaine HCl or saline placebo for up to 72 hours (Figure 1). A significant proportion of patients treated with ZYNRELEF did not receive opioid analgesia (29%) over 72 hours compared to those treated with either bupivacaine HCl (11%) or saline placebo (2%).

Figure 1. Mean Pain Intensity with Activity Over 72 Hours for STUDY 1 (Bunionectomy)

Study 2

In this multicenter, double-blind, parallel-group, active- and placebo-controlled clinical trial (NCT03237481), 418 patients undergoing unilateral open inguinal herniorrhaphy with mesh under general anesthesia were randomized to 1 of the following 3 treatment groups in a 2:2:1 ratio (respectively): ZYNRELEF 300 mg/9 mg, bupivacaine HCl 75 mg, or saline placebo. The mean patient age was 49 years (range 18 to 83) and patients were predominantly male (94%). ZYNRELEF was applied directly into the surgical site, using the cone-shaped applicator, at the end of the procedure, following irrigation and suction of each fascial layer but prior to closure. Bupivacaine HCl and saline placebo were administered by injection and instillation, respectively. Pain intensity was rated by patients using an 11-point NRS out to 72 hours post-dose. Postoperatively, there was no scheduled pain medication regimen; however, patients were allowed rescue medication as needed, which included oxycodone 10 mg orally every 4 hours, morphine 10 mg IV every 2 hours, and/or acetaminophen 1000 mg orally every 6 hours. The primary endpoint was the mean AUC of the NRS pain intensity scores (cumulative pain scores) with activity over the 72-hour period for the ZYNRELEF treatment group compared to the saline placebo treatment group. Secondary endpoints included mean AUC of NRS pain intensity scores over the 72-hour period for the ZYNRELEF treatment group compared to the bupivacaine HCl treatment group, proportion of patients who did not receive opioid analgesia, and total opioid consumption.

Patients treated with ZYNRELEF demonstrated a statistically significant reduction in pain intensity compared to those treated with either bupivacaine HCl or saline placebo for up to 72 hours (Figure 2). A significant proportion of patients treated with ZYNRELEF did not receive opioid analgesia (51%) over 72 hours compared to those treated with either bupivacaine HCl (40%) or saline placebo (22%). A significant reduction in total opioid consumption over 72 hours was also observed for patients treated with ZYNRELEF (median consumption 0 mg) compared to those treated with either bupivacaine HCl (7.3 mg) or saline placebo (11.3 mg).

Figure 2. Mean Pain Intensity with Activity Over 72 Hours for STUDY 2 (Herniorrhaphy)

Study 3

In this multicenter, double-blind, parallel-group, active- and placebo-controlled clinical study (NCT03015532), 222 patients undergoing primary unilateral total knee arthroplasty under general anesthesia were randomized to one of the following treatment groups in a 1:1:1:1 ratio; ZYNRELEF 400 mg/12 mg, ZYNRELEF 400 mg/12 mg plus ropivacaine 50 mg (injected into the posterior capsule), bupivacaine HCl 125 mg, or saline placebo. The mean age was 62 years (range 33 to 85) and 51% of patients were female.

ZYNRELEF was administered, using the cone-shaped applicator, onto the posterior capsule, the anteromedial tissues and periosteum, and the anterolateral tissues and periosteum after cementation of the components. Preoperatively, patients were administered pregabalin 150 mg as a single oral dose and acetaminophen up to 1 g IV. Pain intensity was rated by the patients using an 11-point NRS out to 72 hours post-dose. Postoperatively, there was no scheduled pain medication regimen, and patients were allowed only opioid rescue medication as needed (10 mg oxycodone orally every 4 hours, and/or 10-15 mg morphine IV every 2 hours). The primary endpoint was the AUC of the NRS pain intensity scores (cumulative pain scores) at rest collected over the first 48 hours.

Patients treated with ZYNRELEF demonstrated a significant reduction in pain intensity compared to patients treated with saline placebo for the first 48-hour and 72-hour postoperative periods (Figure 3). There were two patients who did not receive opioid analgesia over 72 hours; one in the ZYNRELEF 400 mg/12 mg + ropivacaine treatment group and one in the bupivacaine HCl treatment group.

Figure 3. Mean Pain Intensity at Rest Over 72 Hours for STUDY 3 (Total Knee Arthroplasty)

16 HOW SUPPLIED/STORAGE AND HANDLING

ZYNRELEF® (bupivacaine and meloxicam) extended-release solution is a clear, pale-yellow to yellow viscous liquid available in 4 presentations. Each single-dose glass vial is filled with a solution of 29.25 mg/mL bupivacaine and 0.88 mg/mL meloxicam. Each presentation described below is supplied in the ZYNRELEF kit containing a vial (packaged in an individual carton) along with sterile, individually packaged components for administration.

Product Presentation (Kit Supplied with Vial Access Needle) |  |  | Vial Access Needle Provided | Luer Lock Syringe(s) Provided | Luer Lock Applicator(s) Provided | Syringe Tip Cap(s) Provided
NDC | Bupivacaine/Meloxicam | Net Quantity Volume [Each ZYNRELEF vial contains overfill to compensate for residual amounts that remain in the vial, vial access needle, Luer lock applicator, and syringe(s) during drug withdrawal and administration] | Vial Access Needle Provided | Luer Lock Syringe(s) Provided | Luer Lock Applicator(s) Provided
47426-501-02 | 400 mg/12 mg | 14 mL | 1 × 20 mL | 2 × 12 mL | 2 | 2
47426-502-02 | 300 mg/9 mg | 10.5 mL | 1 × 20 mL | 1 × 12 mL | 1 | 1
47426-503-01 | 200 mg/6 mg | 7 mL | 1 × 10 mL | 1 × 12 mL | 1 | 1
47426-504-01 | 60 mg/1.8 mg | 2.3 mL | 1 × 10 mL | 1 × 3 mL | 1 | 1

Product Presentation (Kit Supplied with Vented Vial Spike) |  |  | Vented Vial Spike Provided | Luer Lock Syringe(s) Provided | Luer Lock Applicator(s) Provided | Syringe Tip Cap(s) Provided
NDC | Bupivacaine/Meloxicam | Net Quantity Volume [Each ZYNRELEF vial contains overfill to compensate for residual amounts that remain in the vial, vented vial spike, Luer lock applicator, and syringe(s) during drug withdrawal and administration] | Vented Vial Spike Provided | Luer Lock Syringe(s) Provided | Luer Lock Applicator(s) Provided | Syringe Tip Cap(s) Provided
47426-301-02 | 400 mg/12 mg | 14 mL | 1 | 2 × 12 mL | 2 | 2
47426-302-02 | 300 mg/9 mg | 10.5 mL | 1 | 1 × 12 mL | 1 | 1
47426-303-01 | 200 mg/6 mg | 7 mL | 1 | 1 × 12 mL | 1 | 1
47426-304-01 | 60 mg/1.8 mg | 2.3 mL | 1 | 1 × 3 mL | 1 | 1

The following replacement components are individually supplied separate from the kit:

- Carton containing 5 vented vial spikes
- Carton containing 10 Luer lock applicators
- Carton containing 10 sterile 3 mL Luer lock syringes
- Carton containing 8 sterile 12 mL Luer lock syringes
- Carton containing 8 sterile 10 mL vial access needles
- Carton containing 6 sterile 20 mL vial access needles

Storage

Store ZYNRELEF kits at 20°C to 25°C (68°F to 77°F) with excursions permitted between 15°C to 30°C (59°F to 86°F) [see USP Controlled Room Temperature]. Protect from moisture and light.

If ZYNRELEF vials are removed from the kit, store them at controlled room temperature. Protect from light during storage.

17 PATIENT COUNSELING INFORMATION

Cardiovascular Thrombotic Events

Advise patients to be alert for the symptoms of cardiovascular thrombotic events, including chest pain, shortness of breath, weakness, or slurring of speech, and to report any of these symptoms to their health care provider immediately [see Warnings and Precautions (5.1)].

Gastrointestinal Bleeding, Ulceration, and Perforation

Advise patients to report symptoms of ulcerations and bleeding, including epigastric pain, dyspepsia, melena, and hematemesis to their health care provider. In the setting of concomitant use of low-dose aspirin for cardiac prophylaxis, inform patients of the increased risk for and the signs and symptoms of GI bleeding [see Warnings and Precautions (5.2)].

Anaphylactic Reactions

Inform patients of the signs of an anaphylactic reaction (e.g., difficulty breathing, swelling of the face or throat). Instruct patients to seek immediate emergency help if these occur [see Warnings and Precautions (5.9)].

Serious Skin Reactions, including DRESS

Advise patients to contact their healthcare provider as soon as possible if they develop any type of rash or fever [see Warnings and Precautions (5.14, 5.15)].

Methemoglobinemia

Inform patients that use of local anesthetics may cause methemoglobinemia, a serious condition that must be treated promptly. Advise patients or caregivers to seek immediate medical attention if they or someone in their care experience the following signs or symptoms: pale, gray, or blue colored skin (cyanosis); headache; rapid heart rate; shortness of breath; lightheadedness; or fatigue [see Warnings and Precautions (5.12)].

Fetal Toxicity

Inform pregnant women of the risk of the premature closing of the fetal ductus arteriosus if ZYNRELEF or other NSAIDs are used starting at 30 weeks gestation because of the risk of the premature closing of the fetal ductus arteriosus. If treatment with ZYNRELEF is needed for a pregnant woman between about 20 to 30 weeks gestation, advise her that she may need to be monitored for oligohydramnios because meloxicam can be detected in plasma beyond 48 hours after administration [see Warnings and Precautions (5.16) and Use in Specific Populations (8.1)].

Temporary Loss of Sensation Near the Surgical Site

Inform patients in advance that ZYNRELEF can cause temporary loss of sensation near the surgical site.

Use of NSAIDs

Inform patients of the increased risk of gastrointestinal toxicity if an NSAID or salicylate (e.g., diflunisal, salsalate) is used in the postoperative period following administration of ZYNRELEF [see Drug Interactions (7)].

Manufactured for: Heron Therapeutics, Inc., 4242 Campus Point Court, Suite 200, San Diego, CA, 92121, USA.

Patent: https://www.herontx.com/patents/

ZYNRELEF® is a registered trademark of Heron Therapeutics, Inc.

Copyright © 2021 - 2024 Heron Therapeutics, Inc. All rights reserved.

Instructions For Use

ZYNRELEF®
(bupivacaine and meloxicam)
extended-release solution,
for instillation use

400 mg bupivacaine and 12 mg meloxicam
Each mL contains 29.25 mg bupivacaine and 0.88 mg meloxicam

Intended Use

ZYNRELEF is indicated in adults to produce postsurgical analgesia for up to 72 hours after soft tissue, foot and ankle, and other orthopedic procedures in which direct exposure to articular cartilage is avoided.

Limitations of Use

Safety and efficacy have not been established in highly vascular surgeries, such as intrathoracic, large 4 or more level spinal, and head and neck procedures.

Dose Information

A single-dose application of a viscous solution administered directly via a needle-free syringe to coat the affected tissue within the surgical site prior to suturing. Two syringes are provided to aid in application.

Preparing the Product

Only withdraw 7 mL of ZYNRELEF into each syringe. This product does not require mixing. During preparation, do not mix with water, saline or other local anesthetics. Preparation is typically done in the Operating Room. Follow your facility's standard operating procedures regarding aseptic and sterile preparation and disposal of unused contents in the vial.

Storing the Product

ZYNRELEF kit should be stored at 20°C to 25°C (68°F to 77°F) with excursions permitted between 15°C to 30°C (59°F to 86°F) [See USP Controlled Room Temperature], protected from light and moisture.

For Operating Room Preparation

It is recommended that a 2-person team prepare this product: one sterile person and one non-sterile person. If product is prepared in advance of surgery, blue syringe tip caps ➍ may be used to cap the syringe until ready for application. Before administration, remove the blue syringe tip cap and attach the Luer lock applicator ➌.

The ZYNRELEF Kit Contents

Use only the components listed below supplied for use with ZYNRELEF.

➊ Vented Vial Spike (sterile)
➋ 12 mL Luer Lock Syringe (sterile) (2×)
➌ Luer Lock Applicator (sterile) (2×)
➍ Blue Tip Caps (sterile) (2×) (preparation in advance)
➎ 14 mL ZYNRELEF Vial (contents sterile, exterior not sterile)

Preparation
① Prepare Components STERILE Open all components onto sterile field. Note: Prepare all syringe(s) provided in kit. Do not substitute any of the components. Only withdraw 7 mL of ZYNRELEF into each syringe. Note: Vial contains overfill to account for amount that remains in the vial, vented vial spike, Luer lock applicator, and syringe(s) during drug withdrawal and administration. | ② Prepare Vial NON-STERILE; A) Flip cap off of vial and place onto stable non-sterile surface. B) Cleanse septum with alcohol wipe. C) Hold the vial in place for the sterile person to safely insert the vented vial spike.; Do not remove the stopper or attempt to pour the vial contents. |  | ③ Remove Protective Sheath STERILE; A) Remove blue protective sheath from vented vial spike. B) Remove luer cap. | ④ Attach Vented Vial Spike STERILE Push the spike through the septum of the vial until it "snaps" into place. Hold the vented vial spike by the adapter neck to maintain sterility of the vented vial spike and sterile person. NON-STERILE Hold the vial in place while sterile person attaches spike. Note: Place the vial on a firm, flat surface and hold in place while the sterile person attaches the spike.
⑤ Prepare Syringe STERILE Fill the syringe with 7 mL of air before attaching to the vented vial spike. Air from syringe will be pushed into the vial at Step 7 after the vial has been inverted and product has filled the neck of the vial. | ⑥ Prepare for Withdrawal STERILE Attach the air-filled syringe to the vented vial spike. Note: Avoid pushing or pumping the plunger rod up and down at any point in the withdrawal process. NON-STERILE Hold the vial in place until the syringe is attached. |  | ⑦ Withdraw Product STERILE; A) Invert the vial using the syringe. B) Allow product to fill the neck of the vial. C) Push air into vial and wait for the air bubble to rise. D) Withdraw 7 mL of product. It is normal for there to be small air bubbles in the syringe.; Note: Product is very thick. It may take a few minutes to withdraw. NON-STERILE You may assist the sterile person with inverting the vial if necessary by holding the non-sterile vial. | ⑧ Repeat With Second Syringe STERILE; A) Return vial to non-sterile surface. B) Remove syringe from vial and attach Luer lock applicator. C) Place syringe on sterile surface. D) Repeat steps 5–8 with second syringe.; NON-STERILE Hold the vial in place for attachment of second syringe.

Frequently Asked Questions

Can I attempt to do the entire preparation process on my own? It is recommended that this be done as a 2-person team to maintain sterility.

Is there any way to speed up the withdrawal time? The withdrawal time is faster when the vial is at the upper end of the recommended storage conditions (25°C or 77°F). Do not dilute this product in any way.

What if I touch the aluminum collar when attaching the vented vial spike adapter? Replace your sterile gloves and continue with next steps.

Do I have to wait until the vial is inverted to push in air? Proper insertion of air after inverting the vial improves withdrawal time.

Do I need to dilute this product to expand the volume? No. The product should not be diluted.

Can I pour this product in a sterile cup? No, you will be unable to pull an effective dose from the sterile cup due to the thick nature of the product.

What should I do if I drop a syringe or any of the other components? Use replacement kit components that are individually supplied separate from the kit.

Administration Information

Please familiarize yourself with this information before you use this product for the first time.

ZYNRELEF should only be administered with the syringe and Luer lock applicator provided in the ZYNRELEF kit.

Administration

1. ADMINISTER ZYNRELEF VIA INSTILLATION ONLY.
2. ZYNRELEF should not be administered via the following routes:
  - Epidural
  - Intrathecal
  - Intravascular
  - Intra-articular
  - Regional nerve blocks
  - Pre-incisional or pre-procedural locoregional anesthetic techniques
3. ZYNRELEF is applied without a needle into the surgical site following final irrigation and suction and prior to suturing.
  Only apply ZYNRELEF after final irrigation and suction of each layer before closing, if multiple tissue layers are involved.
4. Using the Luer lock applicator attached to the syringe, apply ZYNRELEF to the tissues within the surgical site that could result in pain generation.
5. Use a sufficient amount to coat the tissues. For small spaces, ensure there is not an excess that could be expressed from the site during closure.
6. Only apply ZYNRELEF to the tissue layers below the skin incision and not directly onto the skin.
7. ZYNRELEF does not degrade sutures.
  When tying knots with monofilament sutures, contact with ZYNRELEF may cause knots to loosen or untie due to the viscosity of ZYNRELEF. In vitro studies showed an increase in elasticity with monofilament sutures exposed to ZYNRELEF with unknown clinical significance. Minimize administration of ZYNRELEF near the incision line and wipe off excess ZYNRELEF from the skin prior to suturing. Three or more knots ending in a multi-throw knot (e.g. a Surgeon's knot) are recommended with monofilament sutures. Braided or barbed sutures are recommended, especially for closure of deeper layers.

Important Information

A. The amount of ZYNRELEF required depends upon the surgical area of tissue to be treated.
B. ZYNRELEF spreads easily and covers a large area.
C. Diluting ZYNRELEF is not needed for efficacy.
  ZYNRELEF cannot be mixed with water, saline, or other local anesthetics as the product will become very viscous and difficult to administer.
D. When ZYNRELEF comes in contact with moisture in the tissues, it becomes more viscous, allowing it to stay in place.
E. Avoid additional use of local anesthetics within 96 hours following administration of ZYNRELEF.
  Overall local anesthetic exposure must be considered.

HERON
THERAPEUTICS

Instructions For Use

ZYNRELEF®
(bupivacaine and meloxicam)
extended-release solution,
for instillation use

300 mg bupivacaine and 9 mg meloxicam
Each mL contains 29.25 mg bupivacaine and 0.88 mg meloxicam

Intended Use

ZYNRELEF is indicated in adults to produce postsurgical analgesia for up to 72 hours after soft tissue, foot and ankle, and other orthopedic procedures in which direct exposure to articular cartilage is avoided.

Limitations of Use

Safety and efficacy have not been established in highly vascular surgeries, such as intrathoracic, large 4 or more level spinal, and head and neck procedures.

Dose Information

A single-dose application of a viscous solution administered directly via a needle-free syringe to coat the affected tissue within the surgical site prior to suturing. One syringe is provided to aid in application.

Preparing the Product

Withdraw 10.5 mL of ZYNRELEF into the syringe. This product does not require mixing. During preparation, do not mix with water, saline or other local anesthetics. Preparation is typically done in the Operating Room. Follow your facility's standard operating procedures regarding aseptic and sterile preparation and disposal of unused contents in the vial.

Storing the Product

ZYNRELEF kit should be stored at 20°C to 25°C (68°F to 77°F) with excursions permitted between 15°C to 30°C (59°F to 86°F) [See USP Controlled Room Temperature], protected from light and moisture.

For Operating Room Preparation

It is recommended that a 2-person team prepare this product: one sterile person and one non-sterile person. If product is prepared in advance of surgery, a blue syringe tip cap ➍ may be used to cap the syringe until ready for application. Before administration, remove the blue syringe tip cap and attach the Luer lock applicator ➌.

The ZYNRELEF Kit Contents

Use only the components listed below supplied for use with ZYNRELEF.

➊ Vented Vial Spike (sterile)
➋ 12 mL Luer Lock Syringe (sterile)
➌ Luer Lock Applicator (sterile)
➍ Blue Tip Cap (sterile) (preparation in advance)
➎ 10.5 mL ZYNRELEF Vial (contents sterile, exterior not sterile)

Preparation
① Prepare Components STERILE Open all components onto sterile field. Do not substitute any of the components. Withdraw 10.5 mL of ZYNRELEF into the syringe. Note: Vial contains overfill to account for amount that remains in the vial, vented vial spike, Luer lock applicator, and syringe(s) during drug withdrawal and administration. | ② Prepare Vial NON-STERILE; A) Flip cap off of vial and place onto stable non-sterile surface. B) Cleanse septum with alcohol wipe. C) Hold the vial in place for the sterile person to safely insert the vented vial spike.; Do not remove the stopper or attempt to pour the vial contents. |  | ③ Remove Protective Sheath STERILE; A) Remove blue protective sheath from vented vial spike. B) Remove luer cap. | ④ Attach Vented Vial Spike STERILE Push the spike through the septum of the vial until it "snaps" into place. Hold the vented vial spike by the adapter neck to maintain sterility of the vented vial spike and sterile person. NON-STERILE Hold the vial in place while sterile person attaches spike. Note: Place the vial on a firm, flat surface and hold in place while the sterile person attaches the spike.
⑤ Prepare Syringe STERILE Fill the syringe with 10.5 mL of air before attaching to the vented vial spike. Air from syringe will be pushed into the vial at Step 7 after the vial has been inverted and product has filled the neck of the vial. | ⑥ Prepare for Withdrawal STERILE Attach the air-filled syringe to the vented vial spike. Note: Avoid pushing or pumping the plunger rod up and down at any point in the withdrawal process. NON-STERILE Hold the vial in place until the syringe is attached. |  | ⑦ Withdraw Product STERILE; A) Invert the vial using the syringe. B) Allow product to fill the neck of the vial. C) Push air into vial and wait for the air bubble to rise. D) Withdraw 10.5 mL of product. It is normal for there to be small air bubbles in the syringe.; Note: Product is very thick. It may take a few minutes to withdraw. NON-STERILE You may assist the sterile person with inverting the vial if necessary by holding the non-sterile vial. | ⑧ Attach Luer Lock Applicator STERILE; A) Return vial to non-sterile surface. B) Remove syringe from vial and attach Luer lock applicator. C) Place syringe on sterile surface.

Frequently Asked Questions

Can I attempt to do the entire preparation process on my own? It is recommended that this be done as a 2-person team to maintain sterility.

Is there any way to speed up the withdrawal time? The withdrawal time is faster when the vial is at the upper end of the recommended storage conditions (25°C or 77°F). Do not dilute this product in any way.

What if I touch the aluminum collar when attaching the vented vial spike adapter? Replace your sterile gloves and continue with next steps.

Do I have to wait until the vial is inverted to push in air? Proper insertion of air after inverting the vial improves withdrawal time.

Do I need to dilute this product to expand the volume? No. The product should not be diluted.

Can I pour this product in a sterile cup? No, you will be unable to pull an effective dose from the sterile cup due to the thick nature of the product.

What should I do if I drop a syringe or any of the other components? Use replacement kit components that are individually supplied separate from the kit.

Administration Information

Please familiarize yourself with this information before you use this product for the first time.

ZYNRELEF should only be administered with the syringe and Luer lock applicator provided in the ZYNRELEF kit.

Administration

1. ADMINISTER ZYNRELEF VIA INSTILLATION ONLY.
2. ZYNRELEF should not be administered via the following routes:
  - Epidural
  - Intrathecal
  - Intravascular
  - Intra-articular
  - Regional nerve blocks
  - Pre-incisional or pre-procedural locoregional anesthetic techniques
3. ZYNRELEF is applied without a needle into the surgical site following final irrigation and suction and prior to suturing.
  Only apply ZYNRELEF after final irrigation and suction of each layer before closing, if multiple tissue layers are involved.
4. Using the Luer lock applicator attached to the syringe, apply ZYNRELEF to the tissues within the surgical site that could result in pain generation.
5. Use a sufficient amount to coat the tissues. For small spaces, ensure there is not an excess that could be expressed from the site during closure.
6. Only apply ZYNRELEF to the tissue layers below the skin incision and not directly onto the skin.
7. ZYNRELEF does not degrade sutures.
  When tying knots with monofilament sutures, contact with ZYNRELEF may cause knots to loosen or untie due to the viscosity of ZYNRELEF. In vitro studies showed an increase in elasticity with monofilament sutures exposed to ZYNRELEF with unknown clinical significance. Minimize administration of ZYNRELEF near the incision line and wipe off excess ZYNRELEF from the skin prior to suturing. Three or more knots ending in a multi-throw knot (e.g. a Surgeon's knot) are recommended with monofilament sutures. Braided or barbed sutures are recommended, especially for closure of deeper layers.

Important Information

A. The amount of ZYNRELEF required depends upon the surgical area of tissue to be treated.
B. ZYNRELEF spreads easily and covers a large area.
C. Diluting ZYNRELEF is not needed for efficacy.
  ZYNRELEF cannot be mixed with water, saline, or other local anesthetics as the product will become very viscous and difficult to administer.
D. When ZYNRELEF comes in contact with moisture in the tissues, it becomes more viscous, allowing it to stay in place.
E. Avoid additional use of local anesthetics within 96 hours following administration of ZYNRELEF.
  Overall local anesthetic exposure must be considered.

HERON
THERAPEUTICS

Instructions For Use

ZYNRELEF®
(bupivacaine and meloxicam)
extended-release solution,
for instillation use

200 mg bupivacaine and 6 mg meloxicam
Each mL contains 29.25 mg bupivacaine and 0.88 mg meloxicam

Intended Use

ZYNRELEF is indicated in adults to produce postsurgical analgesia for up to 72 hours after soft tissue, foot and ankle, and other orthopedic procedures in which direct exposure to articular cartilage is avoided.

Limitations of Use

Safety and efficacy have not been established in highly vascular surgeries, such as intrathoracic, large 4 or more level spinal, and head and neck procedures.

Dose Information

A single-dose application of a viscous solution administered directly via a needle-free syringe to coat the affected tissue within the surgical site prior to suturing. One syringe is provided to aid in application.

Preparing the Product

Withdraw 7 mL of ZYNRELEF into the syringe. This product does not require mixing. During preparation, do not mix with water, saline or other local anesthetics. Preparation is typically done in the Operating Room. Follow your facility's standard operating procedures regarding aseptic and sterile preparation and disposal of unused contents in the vial.

Storing the Product

ZYNRELEF kit should be stored at 20°C to 25°C (68°F to 77°F) with excursions permitted between 15°C to 30°C (59°F to 86°F) [See USP Controlled Room Temperature], protected from light and moisture.

For Operating Room Preparation

It is recommended that a 2-person team prepare this product: one sterile person and one non-sterile person. If product is prepared in advance of surgery, a blue syringe tip cap ➍ may be used to cap the syringe until ready for application. Before administration, remove the blue syringe tip cap and attach the Luer lock applicator ➌.

The ZYNRELEF Kit Contents

Use only the components listed below supplied for use with ZYNRELEF.

➊ Vented Vial Spike (sterile)
➋ 12 mL Luer Lock Syringe (sterile)
➌ Luer Lock Applicator (sterile)
➍ Blue Tip Cap (sterile) (preparation in advance)
➎ 7 mL ZYNRELEF Vial (contents sterile, exterior not sterile)

Preparation
① Prepare Components STERILE Open all components onto sterile field. Do not substitute any of the components. Withdraw 7 mL of ZYNRELEF into the syringe. Note: Vial contains overfill to account for amount that remains in the vial, vented vial spike, Luer lock applicator, and syringe during drug withdrawal and administration. | ② Prepare Vial NON-STERILE; A) Flip cap off of vial and place onto stable non-sterile surface. B) Cleanse septum with alcohol wipe. C) Hold the vial in place for the sterile person to safely insert the vented vial spike.; Do not remove the stopper or attempt to pour the vial contents. |  | ③ Remove Protective Sheath STERILE; A) Remove blue protective sheath from vented vial spike. B) Remove luer cap. | ④ Attach Vented Vial Spike STERILE Push the spike through the septum of the vial until it "snaps" into place. Hold the vented vial spike by the adapter neck to maintain sterility of the vented vial spike and sterile person. NON-STERILE Hold the vial in place while sterile person attaches spike. Note: Place the vial on a firm, flat surface and hold in place while the sterile person attaches the spike.
⑤ Prepare Syringe STERILE Fill the syringe with 7 mL of air before attaching to the vented vial spike. Air from syringe will be pushed into the vial at Step 7 after the vial has been inverted and product has filled the neck of the vial. | ⑥ Prepare for Withdrawal STERILE Attach the air-filled syringe to the vented vial spike. Note: Avoid pushing or pumping the plunger rod up and down at any point in the withdrawal process. NON-STERILE Hold the vial in place until the syringe is attached. |  | ⑦ Withdraw Product STERILE; A) Invert the vial using the syringe. B) Allow product to fill the neck of the vial. C) Push air into vial and wait for the air bubble to rise. D) Withdraw 7 mL of product. It is normal for there to be small air bubbles in the syringe.; Note: Product is very thick. It may take a few minutes to withdraw. NON-STERILE You may assist the sterile person with inverting the vial if necessary by holding the non-sterile vial. | ⑧ Attach Luer Lock Applicator STERILE; A) Return vial to non-sterile surface. B) Remove syringe from vial and attach Luer lock applicator. C) Place syringe on sterile surface.

Frequently Asked Questions

Can I attempt to do the entire preparation process on my own? It is recommended that this be done as a 2-person team to maintain sterility.

Is there any way to speed up the withdrawal time? The withdrawal time is faster when the vial is at the upper end of the recommended storage conditions (25°C or 77°F). Do not dilute this product in any way.

What if I touch the aluminum collar when attaching the vented vial spike adapter? Replace your sterile gloves and continue with next steps.

Do I have to wait until the vial is inverted to push in air? Proper insertion of air after inverting the vial improves withdrawal time.

Do I need to dilute this product to expand the volume? No. The product should not be diluted.

Can I pour this product in a sterile cup? No, you will be unable to pull an effective dose from the sterile cup due to the thick nature of the product.

What should I do if I drop a syringe or any of the other components? Use replacement kit components that are individually supplied separate from the kit.

Administration Information

Please familiarize yourself with this information before you use this product for the first time.

ZYNRELEF should only be administered with the syringe and Luer lock applicator provided in the ZYNRELEF kit.

Administration

1. ADMINISTER ZYNRELEF VIA INSTILLATION ONLY.
2. ZYNRELEF should not be administered via the following routes:
  - Epidural
  - Intrathecal
  - Intravascular
  - Intra-articular
  - Regional nerve blocks
  - Pre-incisional or pre-procedural locoregional anesthetic techniques
3. ZYNRELEF is applied without a needle into the surgical site following final irrigation and suction and prior to suturing.
  Only apply ZYNRELEF after final irrigation and suction of each layer before closing, if multiple tissue layers are involved.
4. Using the Luer lock applicator attached to the syringe, apply ZYNRELEF to the tissues within the surgical site that could result in pain generation.
5. Use a sufficient amount to coat the tissues. For small spaces, ensure there is not an excess that could be expressed from the site during closure.
6. Only apply ZYNRELEF to the tissue layers below the skin incision and not directly onto the skin.
7. ZYNRELEF does not degrade sutures.
  When tying knots with monofilament sutures, contact with ZYNRELEF may cause knots to loosen or untie due to the viscosity of ZYNRELEF. In vitro studies showed an increase in elasticity with monofilament sutures exposed to ZYNRELEF with unknown clinical significance. Minimize administration of ZYNRELEF near the incision line and wipe off excess ZYNRELEF from the skin prior to suturing. Three or more knots ending in a multi-throw knot (e.g. a Surgeon's knot) are recommended with monofilament sutures. Braided or barbed sutures are recommended, especially for closure of deeper layers.

Important Information

A. The amount of ZYNRELEF required depends upon the surgical area of tissue to be treated.
B. ZYNRELEF spreads easily and covers a large area.
C. Diluting ZYNRELEF is not needed for efficacy.
  ZYNRELEF cannot be mixed with water, saline, or other local anesthetics as the product will become very viscous and difficult to administer.
D. When ZYNRELEF comes in contact with moisture in the tissues, it becomes more viscous, allowing it to stay in place.
E. Avoid additional use of local anesthetics within 96 hours following administration of ZYNRELEF.
  Overall local anesthetic exposure must be considered.

HERON
THERAPEUTICS

Instructions For Use

ZYNRELEF®
(bupivacaine and meloxicam)
extended-release solution,
for instillation use

60 mg bupivacaine and 1.8 mg meloxicam
Each mL contains 29.25 mg bupivacaine and 0.88 mg meloxicam

Intended Use

ZYNRELEF is indicated in adults to produce postsurgical analgesia for up to 72 hours after soft tissue, foot and ankle, and other orthopedic procedures in which direct exposure to articular cartilage is avoided.

Limitations of Use

Safety and efficacy have not been established in highly vascular surgeries, such as intrathoracic, large 4 or more level spinal, and head and neck procedures.

Dose Information

A single-dose application of a viscous solution administered directly via a needle-free syringe to coat the affected tissue within the surgical site prior to suturing. One syringe is provided to aid in application.

Preparing the Product

Withdraw 2.3 mL of ZYNRELEF into the syringe. This product does not require mixing. During preparation, do not mix with water, saline or other local anesthetics. Preparation is typically done in the Operating Room. Follow your facility's standard operating procedures regarding aseptic and sterile preparation and disposal of unused contents in the vial.

Storing the Product

ZYNRELEF kit should be stored at 20°C to 25°C (68°F to 77°F) with excursions permitted between 15°C to 30°C (59°F to 86°F) [See USP Controlled Room Temperature], protected from light and moisture.

For Operating Room Preparation

It is recommended that a 2-person team prepare this product: one sterile person and one non-sterile person. If product is prepared in advance of surgery, a blue syringe tip cap ➍ may be used to cap the syringe until ready for application. Before administration, remove the blue syringe tip cap and attach the Luer lock applicator ➌.

The ZYNRELEF Kit Contents

Use only the components listed below supplied for use with ZYNRELEF.

➊ Vented Vial Spike (sterile)
➋ 3 mL Luer Lock Syringe (sterile)
➌ Luer Lock Applicator (sterile)
➍ Blue Tip Cap (sterile) (preparation in advance)
➎ 2.3 mL ZYNRELEF Vial (contents sterile, exterior not sterile)

Preparation
① Prepare Components STERILE Open all components onto sterile field. Do not substitute any of the components. Withdraw 2.3 mL of ZYNRELEF into the syringe. Note: Vial contains overfill to account for amount that remains in the vial, vented vial spike, Luer lock applicator, and syringe during drug withdrawal and administration. | ② Prepare Vial NON-STERILE; A) Flip cap off of vial and place onto stable non-sterile surface. B) Cleanse septum with alcohol wipe. C) Hold the vial in place for the sterile person to safely insert the vented vial spike.; Do not remove the stopper or attempt to pour the vial contents. |  | ③ Remove Protective Sheath STERILE; A) Remove blue protective sheath from vented vial spike. B) Remove luer cap. | ④ Attach Vented Vial Spike STERILE Push the spike through the septum of the vial until it "snaps" into place. Hold the vented vial spike by the adapter neck to maintain sterility of the vented vial spike and sterile person. NON-STERILE Hold the vial in place while sterile person attaches spike. Note: Place the vial on a firm, flat surface and hold in place while the sterile person attaches the spike.
⑤ Prepare Syringe STERILE Fill the syringe with 2.3 mL of air before attaching to the vented vial spike. Air from syringe will be pushed into the vial at Step 7 after the vial has been inverted and product has filled the neck of the vial. | ⑥ Prepare for Withdrawal STERILE Attach the air-filled syringe to the vented vial spike. Note: Avoid pushing or pumping the plunger rod up and down at any point in the withdrawal process. NON-STERILE Hold the vial in place until the syringe is attached. |  | ⑦ Withdraw Product STERILE; A) Invert the vial using the syringe. B) Allow product to fill the neck of the vial. C) Push air into vial and wait for the air bubble to rise. D) Withdraw 2.3 mL of product. It is normal for there to be small air bubbles in the syringe.; Note: Product is very thick. It may take a few minutes to withdraw. NON-STERILE You may assist the sterile person with inverting the vial if necessary by holding the non-sterile vial. | ⑧ Attach Luer Lock Applicator STERILE; A) Return vial to non-sterile surface. B) Remove syringe from vial and attach Luer lock applicator. C) Place syringe on sterile surface.

Frequently Asked Questions

Can I attempt to do the entire preparation process on my own? It is recommended that this be done as a 2-person team to maintain sterility.

Is there any way to speed up the withdrawal time? The withdrawal time is faster when the vial is at the upper end of the recommended storage conditions (25°C or 77°F). Do not dilute this product in any way.

What if I touch the aluminum collar when attaching the vented vial spike adapter? Replace your sterile gloves and continue with next steps.

Do I have to wait until the vial is inverted to push in air? Proper insertion of air after inverting the vial improves withdrawal time.

Do I need to dilute this product to expand the volume? No. The product should not be diluted.

Can I pour this product in a sterile cup? No, you will be unable to pull an effective dose from the sterile cup due to the thick nature of the product.

What should I do if I drop a syringe or any of the other components? Use replacement kit components that are individually supplied separate from the kit.

Administration Information

Please familiarize yourself with this information before you use this product for the first time.

ZYNRELEF should only be administered with the syringe and Luer lock applicator provided in the ZYNRELEF kit.

Administration

1. ADMINISTER ZYNRELEF VIA INSTILLATION ONLY.
2. ZYNRELEF should not be administered via the following routes:
  - Epidural
  - Intrathecal
  - Intravascular
  - Intra-articular
  - Regional nerve blocks
  - Pre-incisional or pre-procedural locoregional anesthetic techniques
3. ZYNRELEF is applied without a needle into the surgical site following final irrigation and suction and prior to suturing.
  Only apply ZYNRELEF after final irrigation and suction of each layer before closing, if multiple tissue layers are involved.
4. Using the Luer lock applicator attached to the syringe, apply ZYNRELEF to the tissues within the surgical site that could result in pain generation.
5. Use a sufficient amount to coat the tissues. For small spaces, ensure there is not an excess that could be expressed from the site during closure.
6. Only apply ZYNRELEF to the tissue layers below the skin incision and not directly onto the skin.
7. ZYNRELEF does not degrade sutures.
  When tying knots with monofilament sutures, contact with ZYNRELEF may cause knots to loosen or untie due to the viscosity of ZYNRELEF. In vitro studies showed an increase in elasticity with monofilament sutures exposed to ZYNRELEF with unknown clinical significance. Minimize administration of ZYNRELEF near the incision line and wipe off excess ZYNRELEF from the skin prior to suturing. Three or more knots ending in a multi-throw knot (e.g. a Surgeon's knot) are recommended with monofilament sutures. Braided or barbed sutures are recommended, especially for closure of deeper layers.

Important Information

A. The amount of ZYNRELEF required depends upon the surgical area of tissue to be treated.
B. ZYNRELEF spreads easily and covers a large area.
C. Diluting ZYNRELEF is not needed for efficacy.
  ZYNRELEF cannot be mixed with water, saline, or other local anesthetics as the product will become very viscous and difficult to administer.
D. When ZYNRELEF comes in contact with moisture in the tissues, it becomes more viscous, allowing it to stay in place.
E. Avoid additional use of local anesthetics within 96 hours following administration of ZYNRELEF.
  Overall local anesthetic exposure must be considered.

HERON
THERAPEUTICS

Instructions For Use

ZYNRELEF®
(bupivacaine and meloxicam)
extended-release solution,
for instillation use

400 mg bupivacaine and 12 mg meloxicam
Each mL contains 29.25 mg bupivacaine and 0.88 mg meloxicam

Intended Use

ZYNRELEF is indicated in adults to produce postsurgical analgesia for up to 72 hours after soft tissue, foot and ankle, and other orthopedic procedures in which direct exposure to articular cartilage is avoided.

Limitations of Use

Safety and efficacy have not been established in highly vascular surgeries, such as intrathoracic, large 4 or more level spinal, and head and neck procedures.

Dose Information

A single-dose application of a viscous solution administered directly via a needle-free syringe to coat the affected tissue within the surgical site prior to suturing. Two syringes are provided to aid in application.

Preparing the Product

Withdraw the amount needed up to 14 mL. This product does not require mixing. During preparation, do not mix with water, saline or other local anesthetics. Preparation is typically done in the Operating Room. Follow your facility's standard operating procedures regarding aseptic and sterile preparation and disposal of unused contents in the vial.

Storing the Product

ZYNRELEF kit should be stored at 20°C to 25°C (68°F to 77°F) with excursions permitted between 15°C to 30°C (59°F to 86°F) [See USP Controlled Room Temperature], protected from light and moisture.

For Operating Room Preparation

It is recommended that a 2-person team prepare this product: one sterile person and one non-sterile person. If product is prepared in advance of surgery, blue syringe tip caps ➍ may be used to cap the syringe until ready for application. Before administration, remove the blue syringe tip cap and attach the Luer lock applicator ➌.

The ZYNRELEF Kit Contents

Use only the components listed below supplied for use with ZYNRELEF.

➊ 20 mL Vial Access Needle (VAN) (sterile)
➋ 12 mL Luer Lock Syringe (sterile) (2×)
➌ Luer Lock Applicator (sterile) (2×)
➍ Blue Tip Caps (sterile) (2×) (preparation in advance)
➎ 14 mL ZYNRELEF Vial (contents sterile, exterior not sterile)

Preparation
① Prepare Components NON-STERILE; A) Check packaging for damage or tears. B) Open all components onto the sterile field.; Do not substitute any of the components. | ② Prepare Vial Access Needle STERILE; A) In the sterile field, separate the Vial Access Needle (VAN) into two pieces – base and shroud. B) If the two pieces are locked together, twist and pull apart at the same time. |  | ③ Prepare Vial NON-STERILE; A) Flip cap off of vial. B) Cleanse septum with alcohol wipe. C) Place non-sterile vial into base of sterile VAN.; Do not remove the stopper or attempt to pour the vial contents. Do not touch base of VAN. | ④ Attach Vial Access Needle Shroud STERILE; A) Position shroud above vial. B) Insert needle into the septum of the vial. C) Push down firmly on the shroud until the shroud "snaps" into the base and the needle is fully inserted.; Ensure shroud is fully connected to the base to avoid compromising sterility.
⑤ Attach Syringe STERILE; A) Attach the provided syringe to the top (Luer) of the VAN shroud.; Note: Air does not need to be pushed into the vial. | ⑥ Invert Syringe STERILE; A) Invert syringe and VAN as pictured above. B) Wait until the drug product fills the neck of the vial to cover drug inlet.; Note: Drug inlet is at the base of the needle, not at the tip. |  | ⑦ Withdraw Product STERILE; A) Using a continuous motion, slowly withdraw the desired amount of ZYNRELEF from the vial.; Note: It is normal for there to be air bubbles in the syringe. Note: Product is very thick. It may take approximately 30 seconds to withdraw per syringe. Note: Pushing or pumping the plunger rod up and down at any point may prolong the withdrawal process. | ⑧ Attach Luer Lock Applicator STERILE; A) Remove syringe from VAN and attach Luer lock applicator.; - If product is prepared in advance of surgery, attach only the blue tip cap to the syringe until ready for application. - Before administration, remove the blue tip cap and attach the Luer lock applicator.; B) Place syringe on sterile surface.; Note: Vial contains overfill to account for amount that remains in the components.

Frequently Asked Questions

Can I attempt to do the entire preparation process on my own? A non-sterile person is needed to place the non-sterile vial in the VAN; all other steps are to be performed by the sterile person.

Is there any way to speed up the withdrawal time? The withdrawal time is faster when the vial is at the upper end of the recommended storage condition (25 °C or 77 °F).

Do I need to dilute this product to expand the volume? No. The product should not be diluted.

Can I pour this product in a sterile cup? No, you will be unable to pull an effective dose from the sterile cup due to the thick nature of the product.

What should I do if I drop a syringe or any of the other components? If you compromise sterility of any sterile component of the ZYNRELEF kit, use a new kit or contact HERON CONNECT at 1-844-437-6611 for a replacement.

Administration Information

Please familiarize yourself with this information before you use this product for the first time.

ZYNRELEF should only be administered with the syringe and Luer lock applicator provided in the ZYNRELEF kit.

Administration

1. ADMINISTER ZYNRELEF VIA INSTILLATION ONLY.
2. ZYNRELEF should not be administered via the following routes:
  - Epidural
  - Intrathecal
  - Intravascular
  - Intra-articular
  - Regional nerve blocks
  - Pre-incisional or pre-procedural locoregional anesthetic techniques
3. ZYNRELEF is applied without a needle into the surgical site following final irrigation and suction and prior to suturing.
  Only apply ZYNRELEF after final irrigation and suction of each layer before closing, if multiple tissue layers are involved.
4. Using the Luer lock applicator attached to the syringe, apply ZYNRELEF to the tissues within the surgical site that could result in pain generation.
5. Use a sufficient amount to coat the tissues. For small spaces, ensure there is not an excess that could be expressed from the site during closure.
6. Only apply ZYNRELEF to the tissue layers below the skin incision and not directly onto the skin.
7. ZYNRELEF does not degrade sutures.
  When tying knots with monofilament sutures, contact with ZYNRELEF may cause knots to loosen or untie due to the viscosity of ZYNRELEF. In vitro studies showed an increase in elasticity with monofilament sutures exposed to ZYNRELEF with unknown clinical significance. Minimize administration of ZYNRELEF near the incision line and wipe off excess ZYNRELEF from the skin prior to suturing. Three or more knots ending in a multi-throw knot (e.g. a Surgeon's knot) are recommended with monofilament sutures. Braided or barbed sutures are recommended, especially for closure of deeper layers.

Important Information

A. The amount of ZYNRELEF required depends upon the surgical area of tissue to be treated.
B. ZYNRELEF spreads easily and covers a large area.
C. Diluting ZYNRELEF is not needed for efficacy.
  ZYNRELEF cannot be mixed with water, saline, or other local anesthetics as the product will become very viscous and difficult to administer.
D. When ZYNRELEF comes in contact with moisture in the tissues, it becomes more viscous, allowing it to stay in place.
E. Avoid additional use of local anesthetics within 96 hours following administration of ZYNRELEF.
  Overall local anesthetic exposure must be considered.

HERON
THERAPEUTICS

Instructions For Use

ZYNRELEF®
(bupivacaine and meloxicam)
extended-release solution,
for instillation use

300 mg bupivacaine and 9 mg meloxicam
Each mL contains 29.25 mg bupivacaine and 0.88 mg meloxicam

Intended Use

ZYNRELEF is indicated in adults to produce postsurgical analgesia for up to 72 hours after soft tissue, foot and ankle, and other orthopedic procedures in which direct exposure to articular cartilage is avoided.

Limitations of Use

Safety and efficacy have not been established in highly vascular surgeries, such as intrathoracic, large 4 or more level spinal, and head and neck procedures.

Dose Information

A single-dose application of a viscous solution administered directly via a needle-free syringe to coat the affected tissue within the surgical site prior to suturing. One syringe is provided to aid in application.

Preparing the Product

Withdraw the amount needed up to 10.5 mL. This product does not require mixing. During preparation, do not mix with water, saline or other local anesthetics. Preparation is typically done in the Operating Room. Follow your facility's standard operating procedures regarding aseptic and sterile preparation and disposal of unused contents in the vial.

Storing the Product

ZYNRELEF kit should be stored at 20°C to 25°C (68°F to 77°F) with excursions permitted between 15°C to 30°C (59°F to 86°F) [See USP Controlled Room Temperature], protected from light and moisture.

For Operating Room Preparation

It is recommended that a 2-person team prepare this product: one sterile person and one non-sterile person. If product is prepared in advance of surgery, blue syringe tip cap ➍ may be used to cap the syringe until ready for application. Before administration, remove the blue syringe tip cap and attach the Luer lock applicator ➌.

The ZYNRELEF Kit Contents

Use only the components listed below supplied for use with ZYNRELEF.

➊ 20 mL Vial Access Needle (VAN) (sterile)
➋ 12 mL Luer Lock Syringe (sterile)
➌ Luer Lock Applicator (sterile)
➍ Blue Tip Cap (sterile) (preparation in advance)
➎ 10.5 mL ZYNRELEF Vial (contents sterile, exterior not sterile)

Preparation
① Prepare Components NON-STERILE; A) Check packaging for damage or tears. B) Open all components onto the sterile field.; Do not substitute any of the components. | ② Prepare Vial Access Needle STERILE; A) In the sterile field, separate the Vial Access Needle (VAN) into two pieces – base and shroud. B) If the two pieces are locked together, twist and pull apart at the same time. |  | ③ Prepare Vial NON-STERILE; A) Flip cap off of vial. B) Cleanse septum with alcohol wipe. C) Place non-sterile vial into base of sterile VAN.; Do not remove the stopper or attempt to pour the vial contents. Do not touch base of VAN. | ④ Attach Vial Access Needle Shroud STERILE; A) Position shroud above vial. B) Insert needle into the septum of the vial. C) Push down firmly on the shroud until the shroud "snaps" into the base and the needle is fully inserted.; Ensure shroud is fully connected to the base to avoid compromising sterility.
⑤ Attach Syringe STERILE; A) Attach the provided syringe to the top (Luer) of the VAN shroud.; Note: Air does not need to be pushed into the vial. | ⑥ Invert Syringe STERILE; A) Invert syringe and VAN as pictured above. B) Wait until the drug product fills the neck of the vial to cover drug inlet.; Note: Drug inlet is at the base of the needle, not at the tip. |  | ⑦ Withdraw Product STERILE; A) Using a continuous motion, slowly withdraw the desired amount of ZYNRELEF from the vial.; Note: It is normal for there to be air bubbles in the syringe. Note: Product is very thick. It may take approximately 30 seconds to withdraw per syringe. Note: Pushing or pumping the plunger rod up and down at any point may prolong the withdrawal process. | ⑧ Attach Luer Lock Applicator STERILE; A) Remove syringe from VAN and attach Luer lock applicator.; - If product is prepared in advance of surgery, attach only the blue tip cap to the syringe until ready for application. - Before administration, remove the blue tip cap and attach the Luer lock applicator.; B) Place syringe on sterile surface.; Note: Vial contains overfill to account for amount that remains in the components.

Frequently Asked Questions

Can I attempt to do the entire preparation process on my own? A non-sterile person is needed to place the non-sterile vial in the VAN; all other steps are to be performed by the sterile person.

Is there any way to speed up the withdrawal time? The withdrawal time is faster when the vial is at the upper end of the recommended storage condition (25 °C or 77 °F).

Do I need to dilute this product to expand the volume? No. The product should not be diluted.

Can I pour this product in a sterile cup? No, you will be unable to pull an effective dose from the sterile cup due to the thick nature of the product.

What should I do if I drop a syringe or any of the other components? If you compromise sterility of any sterile component of the ZYNRELEF kit, use a new kit or contact HERON CONNECT at 1-844-437-6611 for a replacement.

Administration Information

Please familiarize yourself with this information before you use this product for the first time.

ZYNRELEF should only be administered with the syringe and Luer lock applicator provided in the ZYNRELEF kit.

Administration

1. ADMINISTER ZYNRELEF VIA INSTILLATION ONLY.
2. ZYNRELEF should not be administered via the following routes:
  - Epidural
  - Intrathecal
  - Intravascular
  - Intra-articular
  - Regional nerve blocks
  - Pre-incisional or pre-procedural locoregional anesthetic techniques
3. ZYNRELEF is applied without a needle into the surgical site following final irrigation and suction and prior to suturing.
  Only apply ZYNRELEF after final irrigation and suction of each layer before closing, if multiple tissue layers are involved.
4. Using the Luer lock applicator attached to the syringe, apply ZYNRELEF to the tissues within the surgical site that could result in pain generation.
5. Use a sufficient amount to coat the tissues. For small spaces, ensure there is not an excess that could be expressed from the site during closure.
6. Only apply ZYNRELEF to the tissue layers below the skin incision and not directly onto the skin.
7. ZYNRELEF does not degrade sutures.
  When tying knots with monofilament sutures, contact with ZYNRELEF may cause knots to loosen or untie due to the viscosity of ZYNRELEF. In vitro studies showed an increase in elasticity with monofilament sutures exposed to ZYNRELEF with unknown clinical significance. Minimize administration of ZYNRELEF near the incision line and wipe off excess ZYNRELEF from the skin prior to suturing. Three or more knots ending in a multi-throw knot (e.g. a Surgeon's knot) are recommended with monofilament sutures. Braided or barbed sutures are recommended, especially for closure of deeper layers.

Important Information

A. The amount of ZYNRELEF required depends upon the surgical area of tissue to be treated.
B. ZYNRELEF spreads easily and covers a large area.
C. Diluting ZYNRELEF is not needed for efficacy.
  ZYNRELEF cannot be mixed with water, saline, or other local anesthetics as the product will become very viscous and difficult to administer.
D. When ZYNRELEF comes in contact with moisture in the tissues, it becomes more viscous, allowing it to stay in place.
E. Avoid additional use of local anesthetics within 96 hours following administration of ZYNRELEF.
  Overall local anesthetic exposure must be considered.

HERON
THERAPEUTICS

Instructions For Use

ZYNRELEF®
(bupivacaine and meloxicam)
extended-release solution,
for instillation use

200 mg bupivacaine and 6 mg meloxicam
Each mL contains 29.25 mg bupivacaine and 0.88 mg meloxicam

Intended Use

ZYNRELEF is indicated in adults to produce postsurgical analgesia for up to 72 hours after soft tissue, foot and ankle, and other orthopedic procedures in which direct exposure to articular cartilage is avoided.

Limitations of Use

Safety and efficacy have not been established in highly vascular surgeries, such as intrathoracic, large 4 or more level spinal, and head and neck procedures.

Dose Information

A single-dose application of a viscous solution administered directly via a needle-free syringe to coat the affected tissue within the surgical site prior to suturing. One syringe is provided to aid in application.

Preparing the Product

Withdraw the amount needed up to 7 mL. This product does not require mixing. During preparation, do not mix with water, saline or other local anesthetics. Preparation is typically done in the Operating Room. Follow your facility's standard operating procedures regarding aseptic and sterile preparation and disposal of unused contents in the vial.

Storing the Product

ZYNRELEF kit should be stored at 20°C to 25°C (68°F to 77°F) with excursions permitted between 15°C to 30°C (59°F to 86°F) [See USP Controlled Room Temperature], protected from light and moisture.

For Operating Room Preparation

It is recommended that a 2-person team prepare this product: one sterile person and one non-sterile person. If product is prepared in advance of surgery, blue syringe tip cap ➍ may be used to cap the syringe until ready for application. Before administration, remove the blue syringe tip cap and attach the Luer lock applicator ➌.

The ZYNRELEF Kit Contents

Use only the components listed below supplied for use with ZYNRELEF.

➊ 10 mL Vial Access Needle (VAN) (sterile)
➋ 12 mL Luer Lock Syringe (sterile)
➌ Luer Lock Applicator (sterile)
➍ Blue Tip Cap (sterile) (preparation in advance)
➎ 7 mL ZYNRELEF Vial (contents sterile, exterior not sterile)

Preparation
① Prepare Components NON-STERILE; A) Check packaging for damage or tears. B) Open all components onto the sterile field.; Do not substitute any of the components. | ② Prepare Vial Access Needle STERILE; A) In the sterile field, separate the Vial Access Needle (VAN) into two pieces – base and shroud. B) If the two pieces are locked together, twist and pull apart at the same time. |  | ③ Prepare Vial NON-STERILE; A) Flip cap off of vial. B) Cleanse septum with alcohol wipe. C) Place non-sterile vial into base of sterile VAN.; Do not remove the stopper or attempt to pour the vial contents. Do not touch base of VAN. | ④ Attach Vial Access Needle Shroud STERILE; A) Position shroud above vial. B) Insert needle into the septum of the vial. C) Push down firmly on the shroud until the shroud "snaps" into the base and the needle is fully inserted.; Ensure shroud is fully connected to the base to avoid compromising sterility.
⑤ Attach Syringe STERILE; A) Attach the provided syringe to the top (Luer) of the VAN shroud.; Note: Air does not need to be pushed into the vial. | ⑥ Invert Syringe STERILE; A) Invert syringe and VAN as pictured above. B) Wait until the drug product fills the neck of the vial to cover drug inlet.; Note: Drug inlet is at the base of the needle, not at the tip. |  | ⑦ Withdraw Product STERILE; A) Using a continuous motion, slowly withdraw the desired amount of ZYNRELEF from the vial.; Note: It is normal for there to be air bubbles in the syringe. Note: Product is very thick. It may take approximately 30 seconds to withdraw per syringe. Note: Pushing or pumping the plunger rod up and down at any point may prolong the withdrawal process. | ⑧ Attach Luer Lock Applicator STERILE; A) Remove syringe from VAN and attach Luer lock applicator.; - If product is prepared in advance of surgery, attach only the blue tip cap to the syringe until ready for application. - Before administration, remove the blue tip cap and attach the Luer lock applicator.; B) Place syringe on sterile surface.; Note: Vial contains overfill to account for amount that remains in the components.

Frequently Asked Questions

Can I attempt to do the entire preparation process on my own? A non-sterile person is needed to place the non-sterile vial in the VAN; all other steps are to be performed by the sterile person.

Is there any way to speed up the withdrawal time? The withdrawal time is faster when the vial is at the upper end of the recommended storage condition (25 °C or 77 °F).

Do I need to dilute this product to expand the volume? No. The product should not be diluted.

Can I pour this product in a sterile cup? No, you will be unable to pull an effective dose from the sterile cup due to the thick nature of the product.

What should I do if I drop a syringe or any of the other components? If you compromise sterility of any sterile component of the ZYNRELEF kit, use a new kit or contact HERON CONNECT at 1-844-437-6611 for a replacement.

Administration Information

Please familiarize yourself with this information before you use this product for the first time.

ZYNRELEF should only be administered with the syringe and Luer lock applicator provided in the ZYNRELEF kit.

Administration

1. ADMINISTER ZYNRELEF VIA INSTILLATION ONLY.
2. ZYNRELEF should not be administered via the following routes:
  - Epidural
  - Intrathecal
  - Intravascular
  - Intra-articular
  - Regional nerve blocks
  - Pre-incisional or pre-procedural locoregional anesthetic techniques
3. ZYNRELEF is applied without a needle into the surgical site following final irrigation and suction and prior to suturing.
  Only apply ZYNRELEF after final irrigation and suction of each layer before closing, if multiple tissue layers are involved.
4. Using the Luer lock applicator attached to the syringe, apply ZYNRELEF to the tissues within the surgical site that could result in pain generation.
5. Use a sufficient amount to coat the tissues. For small spaces, ensure there is not an excess that could be expressed from the site during closure.
6. Only apply ZYNRELEF to the tissue layers below the skin incision and not directly onto the skin.
7. ZYNRELEF does not degrade sutures.
  When tying knots with monofilament sutures, contact with ZYNRELEF may cause knots to loosen or untie due to the viscosity of ZYNRELEF. In vitro studies showed an increase in elasticity with monofilament sutures exposed to ZYNRELEF with unknown clinical significance. Minimize administration of ZYNRELEF near the incision line and wipe off excess ZYNRELEF from the skin prior to suturing. Three or more knots ending in a multi-throw knot (e.g. a Surgeon's knot) are recommended with monofilament sutures. Braided or barbed sutures are recommended, especially for closure of deeper layers.

Important Information

A. The amount of ZYNRELEF required depends upon the surgical area of tissue to be treated.
B. ZYNRELEF spreads easily and covers a large area.
C. Diluting ZYNRELEF is not needed for efficacy.
  ZYNRELEF cannot be mixed with water, saline, or other local anesthetics as the product will become very viscous and difficult to administer.
D. When ZYNRELEF comes in contact with moisture in the tissues, it becomes more viscous, allowing it to stay in place.
E. Avoid additional use of local anesthetics within 96 hours following administration of ZYNRELEF.
  Overall local anesthetic exposure must be considered.

HERON
THERAPEUTICS

Instructions For Use

ZYNRELEF®
(bupivacaine and meloxicam)
extended-release solution,
for instillation use

60 mg bupivacaine and 1.8 mg meloxicam
Each mL contains 29.25 mg bupivacaine and 0.88 mg meloxicam

Intended Use

ZYNRELEF is indicated in adults to produce postsurgical analgesia for up to 72 hours after soft tissue, foot and ankle, and other orthopedic procedures in which direct exposure to articular cartilage is avoided.

Limitations of Use

Safety and efficacy have not been established in highly vascular surgeries, such as intrathoracic, large 4 or more level spinal, and head and neck procedures.

Dose Information

A single-dose application of a viscous solution administered directly via a needle-free syringe to coat the affected tissue within the surgical site prior to suturing. One syringe is provided to aid in application.

Preparing the Product

Withdraw the amount needed up to 2.3 mL. This product does not require mixing. During preparation, do not mix with water, saline or other local anesthetics. Preparation is typically done in the Operating Room. Follow your facility's standard operating procedures regarding aseptic and sterile preparation and disposal of unused contents in the vial.

Storing the Product

ZYNRELEF kit should be stored at 20°C to 25°C (68°F to 77°F) with excursions permitted between 15°C to 30°C (59°F to 86°F) [See USP Controlled Room Temperature], protected from light and moisture.

For Operating Room Preparation

It is recommended that a 2-person team prepare this product: one sterile person and one non-sterile person. If product is prepared in advance of surgery, blue syringe tip cap ➍ may be used to cap the syringe until ready for application. Before administration, remove the blue syringe tip cap and attach the Luer lock applicator ➌.

The ZYNRELEF Kit Contents

Use only the components listed below supplied for use with ZYNRELEF.

➊ 10 mL Vial Access Needle (VAN) (sterile)
➋ 3 mL Luer Lock Syringe (sterile)
➌ Luer Lock Applicator (sterile)
➍ Blue Tip Cap (sterile) (preparation in advance)
➎ 2.3 mL ZYNRELEF Vial (contents sterile, exterior not sterile)

Preparation
① Prepare Components NON-STERILE; A) Check packaging for damage or tears. B) Open all components onto the sterile field.; Do not substitute any of the components. | ② Prepare Vial Access Needle STERILE; A) In the sterile field, separate the Vial Access Needle (VAN) into two pieces – base and shroud. B) If the two pieces are locked together, twist and pull apart at the same time. |  | ③ Prepare Vial NON-STERILE; A) Flip cap off of vial. B) Cleanse septum with alcohol wipe. C) Place non-sterile vial into base of sterile VAN.; Do not remove the stopper or attempt to pour the vial contents. Do not touch base of VAN. | ④ Attach Vial Access Needle Shroud STERILE; A) Position shroud above vial. B) Insert needle into the septum of the vial. C) Push down firmly on the shroud until the shroud "snaps" into the base and the needle is fully inserted.; Ensure shroud is fully connected to the base to avoid compromising sterility.
⑤ Attach Syringe STERILE; A) Attach the provided syringe to the top (Luer) of the VAN shroud.; Note: Air does not need to be pushed into the vial. | ⑥ Invert Syringe STERILE; A) Invert syringe and VAN as pictured above. B) Wait until the drug product fills the neck of the vial to cover drug inlet.; Note: Drug inlet is at the base of the needle, not at the tip. |  | ⑦ Withdraw Product STERILE; A) Using a continuous motion, slowly withdraw the desired amount of ZYNRELEF from the vial.; Note: It is normal for there to be air bubbles in the syringe. Note: Product is very thick. It may take approximately 30 seconds to withdraw per syringe. Note: Pushing or pumping the plunger rod up and down at any point may prolong the withdrawal process. | ⑧ Attach Luer Lock Applicator STERILE; A) Remove syringe from VAN and attach Luer lock applicator.; - If product is prepared in advance of surgery, attach only the blue tip cap to the syringe until ready for application. - Before administration, remove the blue tip cap and attach the Luer lock applicator.; B) Place syringe on sterile surface.; Note: Vial contains overfill to account for amount that remains in the components.

Frequently Asked Questions

Can I attempt to do the entire preparation process on my own? A non-sterile person is needed to place the non-sterile vial in the VAN; all other steps are to be performed by the sterile person.

Is there any way to speed up the withdrawal time? The withdrawal time is faster when the vial is at the upper end of the recommended storage condition (25 °C or 77 °F).

Do I need to dilute this product to expand the volume? No. The product should not be diluted.

Can I pour this product in a sterile cup? No, you will be unable to pull an effective dose from the sterile cup due to the thick nature of the product.

What should I do if I drop a syringe or any of the other components? If you compromise sterility of any sterile component of the ZYNRELEF kit, use a new kit or contact HERON CONNECT at 1-844-437-6611 for a replacement.

Administration Information

Please familiarize yourself with this information before you use this product for the first time.

ZYNRELEF should only be administered with the syringe and Luer lock applicator provided in the ZYNRELEF kit.

Administration

1. ADMINISTER ZYNRELEF VIA INSTILLATION ONLY.
2. ZYNRELEF should not be administered via the following routes:
  - Epidural
  - Intrathecal
  - Intravascular
  - Intra-articular
  - Regional nerve blocks
  - Pre-incisional or pre-procedural locoregional anesthetic techniques
3. ZYNRELEF is applied without a needle into the surgical site following final irrigation and suction and prior to suturing.
  Only apply ZYNRELEF after final irrigation and suction of each layer before closing, if multiple tissue layers are involved.
4. Using the Luer lock applicator attached to the syringe, apply ZYNRELEF to the tissues within the surgical site that could result in pain generation.
5. Use a sufficient amount to coat the tissues. For small spaces, ensure there is not an excess that could be expressed from the site during closure.
6. Only apply ZYNRELEF to the tissue layers below the skin incision and not directly onto the skin.
7. ZYNRELEF does not degrade sutures.
  When tying knots with monofilament sutures, contact with ZYNRELEF may cause knots to loosen or untie due to the viscosity of ZYNRELEF. In vitro studies showed an increase in elasticity with monofilament sutures exposed to ZYNRELEF with unknown clinical significance. Minimize administration of ZYNRELEF near the incision line and wipe off excess ZYNRELEF from the skin prior to suturing. Three or more knots ending in a multi-throw knot (e.g. a Surgeon's knot) are recommended with monofilament sutures. Braided or barbed sutures are recommended, especially for closure of deeper layers.

Important Information

A. The amount of ZYNRELEF required depends upon the surgical area of tissue to be treated.
B. ZYNRELEF spreads easily and covers a large area.
C. Diluting ZYNRELEF is not needed for efficacy.
  ZYNRELEF cannot be mixed with water, saline, or other local anesthetics as the product will become very viscous and difficult to administer.
D. When ZYNRELEF comes in contact with moisture in the tissues, it becomes more viscous, allowing it to stay in place.
E. Avoid additional use of local anesthetics within 96 hours following administration of ZYNRELEF.
  Overall local anesthetic exposure must be considered.

HERON
THERAPEUTICS

PRINCIPAL DISPLAY PANEL - Kit Carton - 14 mL

ZYNRELEF®
(bupivacaine and meloxicam)
extended-release solution

400 mg bupivacaine and 12 mg meloxicam
Each mL contains 29.25 mg bupivacaine and 0.88 mg meloxicam

Single-Dose Application
For Instillation Use

Refer to Instructions for Use

See Prescribing Information for Dosage, Preparation, and
Administration

Do Not Substitute Components

Use only the supplied components in this kit for preparation

Do NOT remove crimp seal

NDC 47426-301-02

Store ZYNRELEF kit at 20°C to 25°C
(68°F to 77°F) with excursions
permitted between 15°C to 30°C (59°F
to 86°F) [See USP Controlled Room
Temperature]

Protect from light and moisture

Each Kit Contains:

- One single-dose vial containing 400 mg
  bupivacaine and 12 mg meloxicam in a
  non-sterile carton. The contents of the vial
  are sterile.
  Discard unused portion.

Vial Contents Sterile
Vial exterior NOT STERILE

- One sterile vented vial spike
- Two sterile 12 mL Luer Lock syringes
- Two sterile Luer lock applicators
- Two sterile syringe tip caps
- Instructions for Use and
  Prescribing Information

Vial Contents: 14 mL*
Withdraw 14 mL to deliver 13.5 mL

Rx Only

PRINCIPAL DISPLAY PANEL - Kit Carton - 10.5 mL

ZYNRELEF®
(bupivacaine and meloxicam)
extended-release solution

300 mg bupivacaine and 9 mg meloxicam
Each mL contains 29.25 mg bupivacaine and 0.88 mg meloxicam

Single-Dose Application
For Instillation Use

Refer to Instructions for Use

See Prescribing Information for Dosage, Preparation, and
Administration

Do Not Substitute Components

Use only the supplied components in this kit for preparation

Do NOT remove crimp seal

NDC 47426-302-02

Store ZYNRELEF kit at 20°C to 25°C
(68°F to 77°F) with excursions
permitted between 15°C to 30°C (59°F
to 86°F) [See USP Controlled Room
Temperature]

Protect from light and moisture

Each Kit Contains:

- One single-dose vial containing 300 mg
  bupivacaine and 9 mg meloxicam in a
  non-sterile carton. The contents of the vial
  are sterile.
  Discard unused portion.

Vial Contents Sterile
Vial exterior NOT STERILE

- One sterile vented vial spike
- One sterile 12 mL Luer Lock syringe
- One sterile Luer lock applicator
- One sterile syringe tip cap
- Instructions for Use and
  Prescribing Information

Vial Contents: 10.5 mL*
Withdraw 10.5 mL to deliver 10.2 mL

Rx Only

PRINCIPAL DISPLAY PANEL - Kit Carton - 7 mL

ZYNRELEF®
(bupivacaine and meloxicam)
extended-release solution

200 mg bupivacaine and 6 mg meloxicam
Each mL contains 29.25 mg bupivacaine and 0.88 mg meloxicam

Single-Dose Application
For Instillation Use

Refer to Instructions for Use

See Prescribing Information for Dosage, Preparation, and
Administration

Do Not Substitute Components

Use only the supplied components in this kit for preparation

Do NOT remove crimp seal

NDC 47426-303-01

Store ZYNRELEF kit at 20°C to 25°C
(68°F to 77°F) with excursions
permitted between 15°C to 30°C (59°F
to 86°F) [See USP Controlled Room
Temperature]

Protect from light and moisture

Each Kit Contains:

- One single-dose vial containing 200 mg
  bupivacaine and 6 mg meloxicam in a
  non-sterile carton. The contents of the vial
  are sterile.
  Discard unused portion.

Vial Contents Sterile
Vial exterior NOT STERILE

- One sterile vented vial spike
- One sterile 12 mL Luer Lock syringe
- One sterile Luer lock applicator
- One sterile syringe tip cap
- Instructions for Use and
  Prescribing Information

Vial Contents: 7 mL*
Withdraw 7 mL to deliver 6.7 mL

Rx Only

PRINCIPAL DISPLAY PANEL - Kit Carton - 2.3 mL

ZYNRELEF®
(bupivacaine and meloxicam)
extended-release solution

60 mg bupivacaine and 1.8 mg meloxicam
Each mL contains 29.25 mg bupivacaine and 0.88 mg meloxicam

Single-Dose Application
For Instillation Use

Refer to Instructions for Use

See Prescribing Information for Dosage, Preparation, and
Administration

Do Not Substitute Components

Use only the supplied components in this kit for preparation

Do NOT remove crimp seal

NDC 47426-304-01

Store ZYNRELEF kit at 20°C to 25°C
(68°F to 77°F) with excursions
permitted between 15°C to 30°C (59°F
to 86°F) [See USP Controlled Room
Temperature]

Protect from light and moisture

Each Kit Contains:

- One single-dose vial containing 60 mg
  bupivacaine and 1.8 mg meloxicam in a
  non-sterile carton. The contents of the vial
  are sterile.
  Discard unused portion.

Vial Contents Sterile
Vial exterior NOT STERILE

- One sterile vented vial spike
- One sterile 3 mL Luer Lock syringe
- One sterile Luer lock applicator
- One sterile syringe tip cap
- Instructions for Use and
  Prescribing Information

Vial Contents: 2.3 mL*
Withdraw 2.3 mL to deliver 2 mL

Rx Only

PRINCIPAL DISPLAY PANEL - Kit Carton - 14 mL - NDC 47426-501

ZYNRELEF®
(bupivacaine and meloxicam)
extended-release solution

400 mg bupivacaine and 12 mg meloxicam
Each mL contains 29.25 mg bupivacaine and 0.88 mg meloxicam

Single-Dose Application
For Instillation Use

Refer to Instructions for Use

See Prescribing Information for Dosage, Preparation,
and Administration

Do Not Substitute Components

Use only the supplied components in this kit for preparation

Do NOT remove crimp seal

NDC 47426-501-02

Store ZYNRELEF kit at 20°C to 25°C
(68°F to 77°F) with excursions
permitted between 15°C to 30°C (59°F
to 86°F) [See USP Controlled Room
Temperature]

Protect from light and moisture

Each Kit Contains:

- One single-dose vial containing 400 mg
  bupivacaine and 12 mg meloxicam in a
  non-sterile carton. The contents of the vial
  are sterile.
  Discard unused portion.

Vial Contents Sterile
Vial exterior NOT STERILE

- One 20 mL sterile vial access needle
- Two sterile 12 mL Luer Lock syringes
- Two sterile Luer lock applicators
- Two sterile syringe tip caps
- Instructions for Use and
  Prescribing Information

Vial Contents: 14 mL*
Withdraw 14 mL to deliver 13.5 mL

Rx Only

PRINCIPAL DISPLAY PANEL - Kit Carton - 10.5 mL - NDC 47426-502

ZYNRELEF®
(bupivacaine and meloxicam)
extended-release solution

300 mg bupivacaine and 9 mg meloxicam
Each mL contains 29.25 mg bupivacaine and 0.88 mg meloxicam

Single-Dose Application
For Instillation Use

Refer to Instructions for Use

See Prescribing Information for Dosage, Preparation,
and Administration

Do Not Substitute Components

Use only the supplied components in this kit for preparation

Do NOT remove crimp seal

NDC 47426-502-02

Store ZYNRELEF kit at 20°C to 25°C
(68°F to 77°F) with excursions
permitted between 15°C to 30°C (59°F
to 86°F) [See USP Controlled Room
Temperature]

Protect from light and moisture

Each Kit Contains:

- One single-dose vial containing 300 mg
  bupivacaine and 9 mg meloxicam in a non-sterile
  carton. The contents of the vial
  are sterile.
  Discard unused portion.

Vial Contents Sterile
Vial exterior NOT STERILE

- One 20 mL sterile vial access needle
- One sterile 12 mL Luer Lock syringe
- One sterile Luer lock applicator
- One sterile syringe tip cap
- Instructions for Use and
  Prescribing Information

Vial Contents: 10.5 mL*
Withdraw 10.5 mL to deliver 10.2 mL

Rx Only

PRINCIPAL DISPLAY PANEL - Kit Carton - 7 mL - NDC 47426-503

ZYNRELEF®
(bupivacaine and meloxicam)
extended-release solution

200 mg bupivacaine and 6 mg meloxicam
Each mL contains 29.25 mg bupivacaine and 0.88 mg meloxicam

Single-Dose Application
For Instillation Use

Refer to Instructions for Use

See Prescribing Information for Dosage, Preparation, and
Administration

Do Not Substitute Components

Use only the supplied components in this kit for preparation

Do NOT remove crimp seal

NDC 47426-503-01

Store ZYNRELEF kit at 20°C to 25°C
(68°F to 77°F) with excursions
permitted between 15°C to 30°C (59°F
to 86°F) [See USP Controlled Room
Temperature]

Protect from light and moisture

Each Kit Contains:

- One single-dose vial containing 200 mg
  bupivacaine and 6 mg meloxicam in a
  non-sterile carton. The contents of the vial
  are sterile.
  Discard unused portion.

Vial Contents Sterile
Vial exterior NOT STERILE

- One 10 mL sterile vial access needle
- One sterile 12 mL Luer Lock syringe
- One sterile Luer lock applicator
- One sterile syringe tip cap
- Instructions for Use and
  Prescribing Information

Vial Contents: 7 mL*
Withdraw 7 mL to deliver 6.7 mL

Rx Only

PRINCIPAL DISPLAY PANEL - Kit Carton - 2.3 mL - NDC 47426-504

ZYNRELEF®
(bupivacaine and meloxicam)
extended-release solution

60 mg bupivacaine and 1.8 mg meloxicam
Each mL contains 29.25 mg bupivacaine and 0.88 mg meloxicam

Single-Dose Application
For Instillation Use

Refer to Instructions for Use

See Prescribing Information for Dosage, Preparation, and
Administration

Do Not Substitute Components

Use only the supplied components in this kit for preparation

Do NOT remove crimp seal

NDC 47426-504-01

Store ZYNRELEF kit at 20°C to 25°C
(68°F to 77°F) with excursions
permitted between 15°C to 30°C (59°F
to 86°F) [See USP Controlled Room
Temperature]

Protect from light and moisture

Each Kit Contains:

- One single-dose vial containing 60 mg
  bupivacaine and 1.8 mg meloxicam in a
  non-sterile carton. The contents of the vial
  are sterile.
  Discard unused portion.

Vial Contents Sterile
Vial exterior NOT STERILE

- One 10 mL sterile vial access needle
- One sterile 3 mL Luer Lock syringe
- One sterile Luer lock applicator
- One sterile syringe tip cap
- Instructions for Use and
  Prescribing Information

Vial Contents: 2.3 mL*
Withdraw 2.3 mL to deliver 2 mL

Rx Only